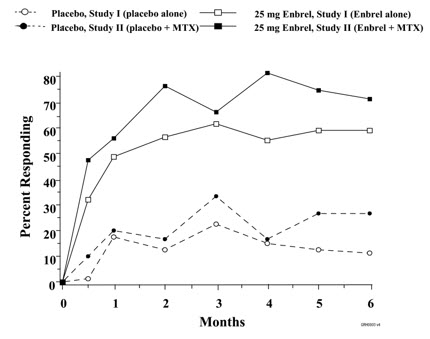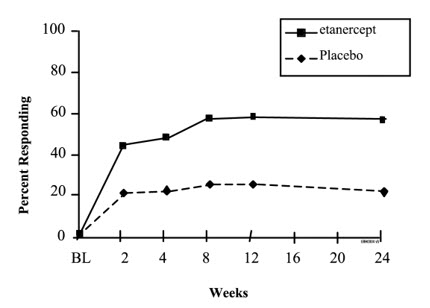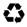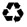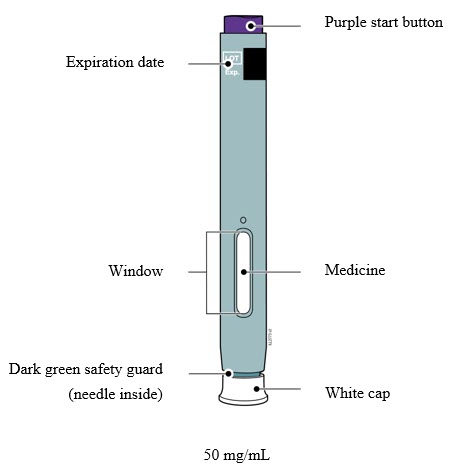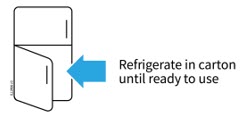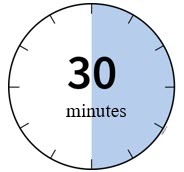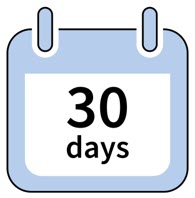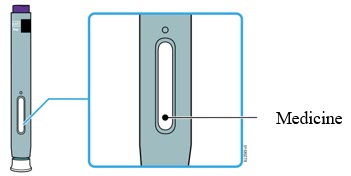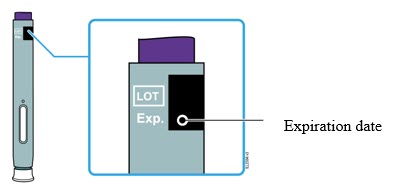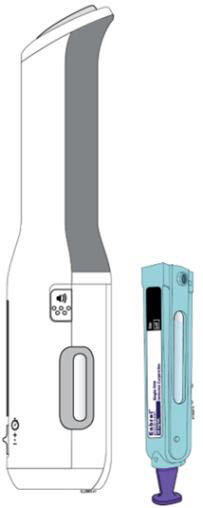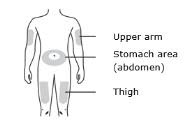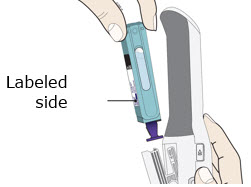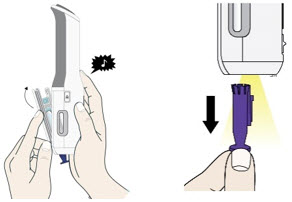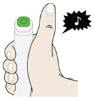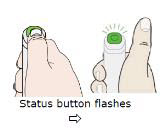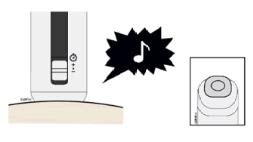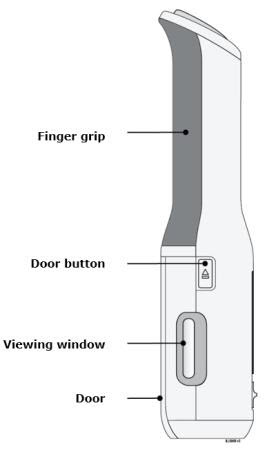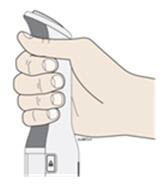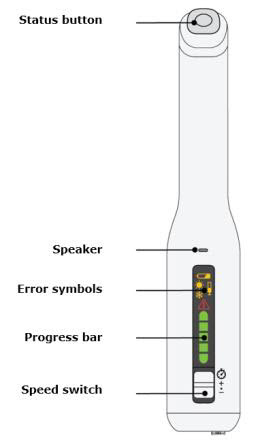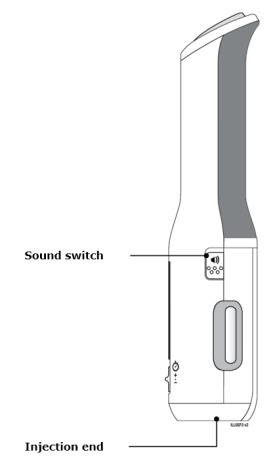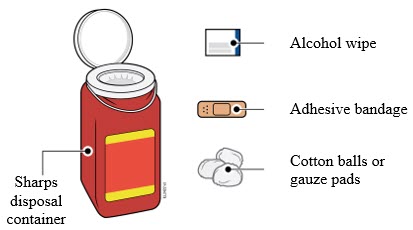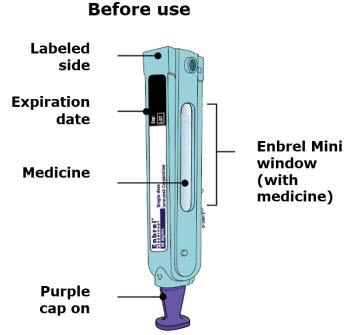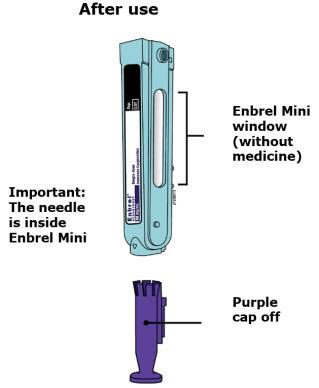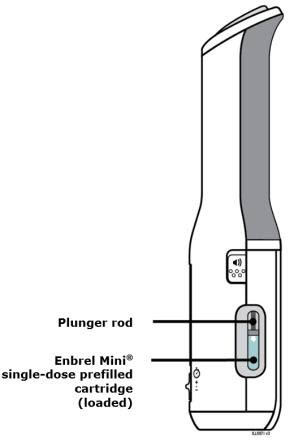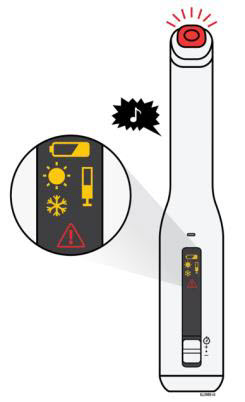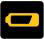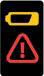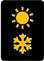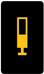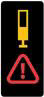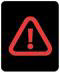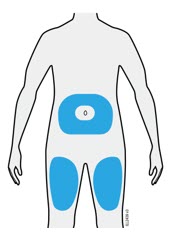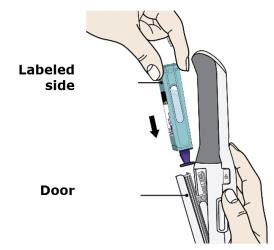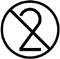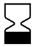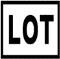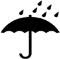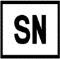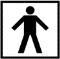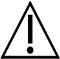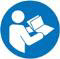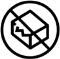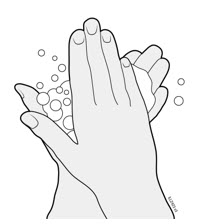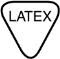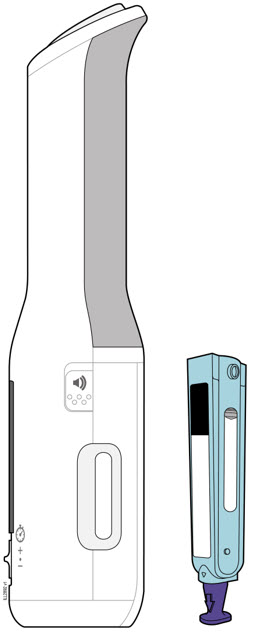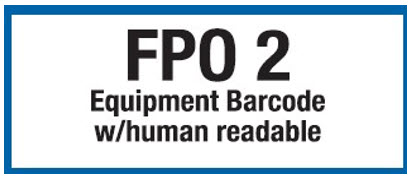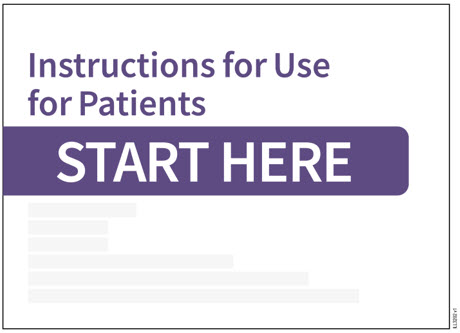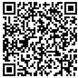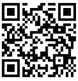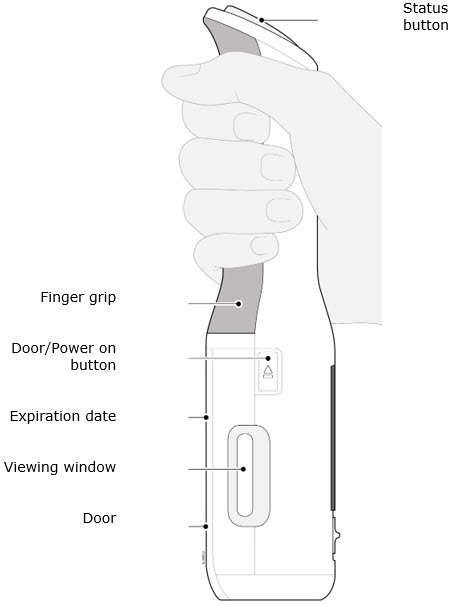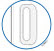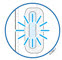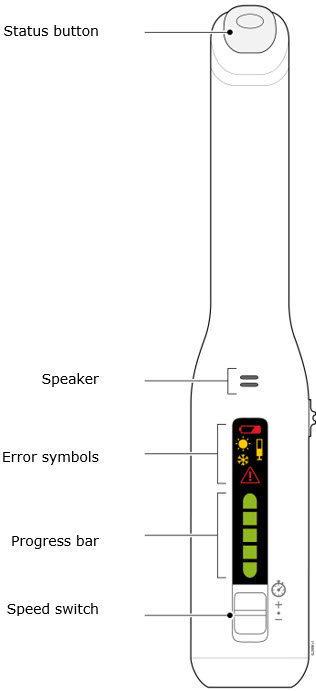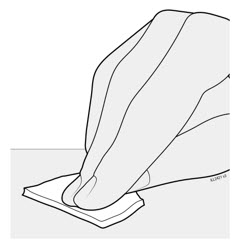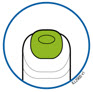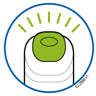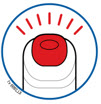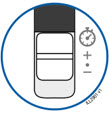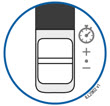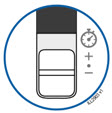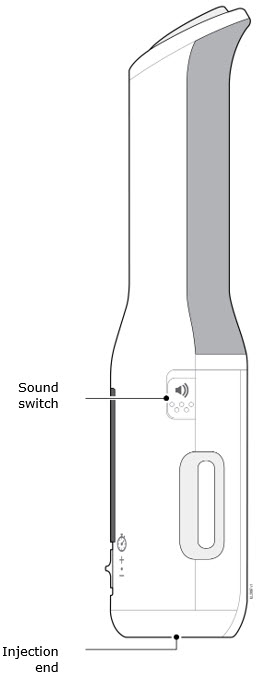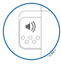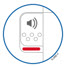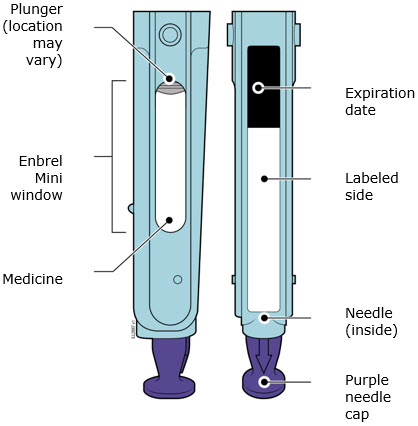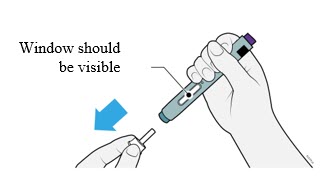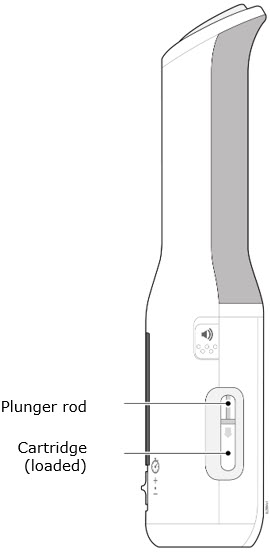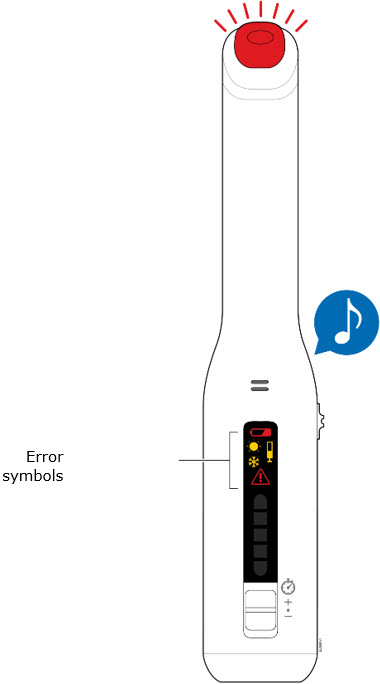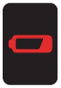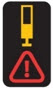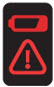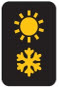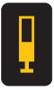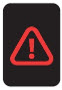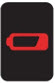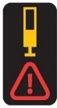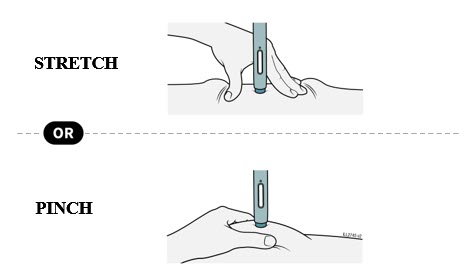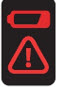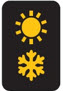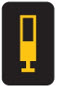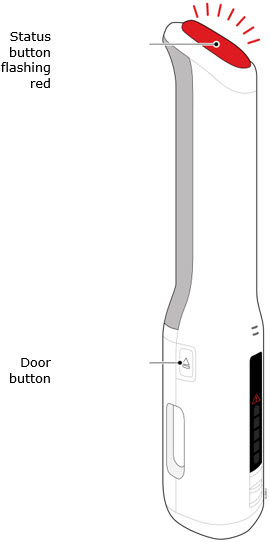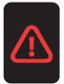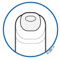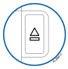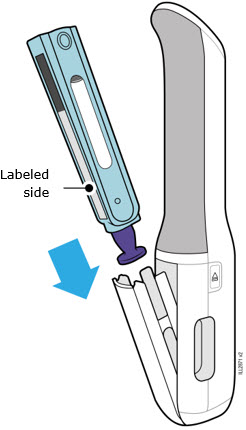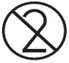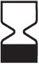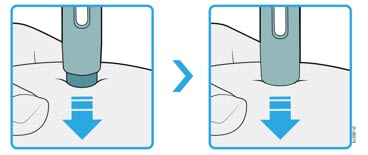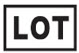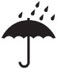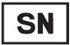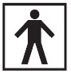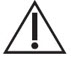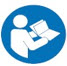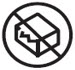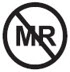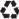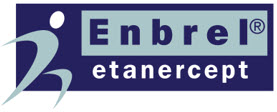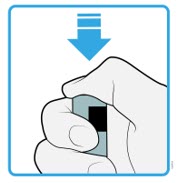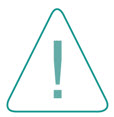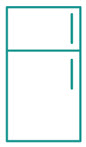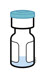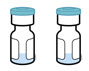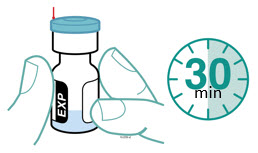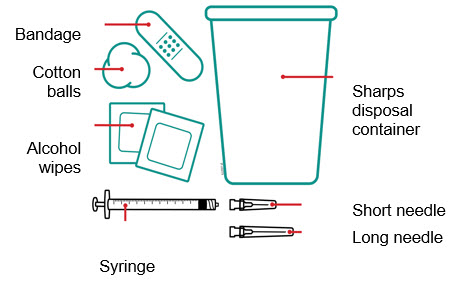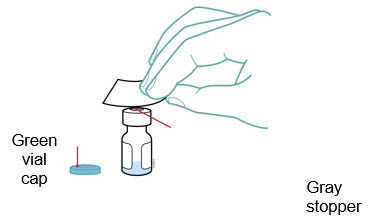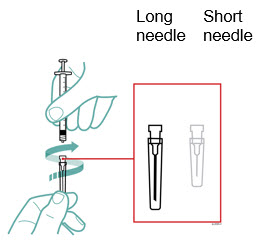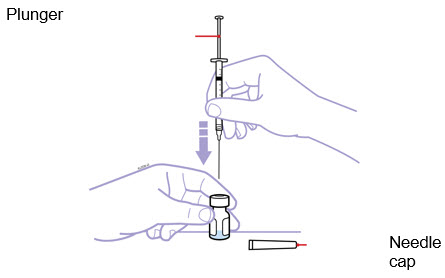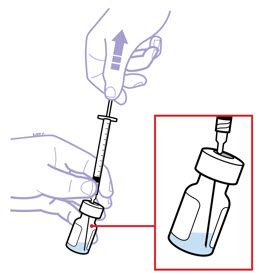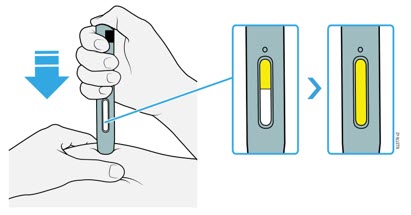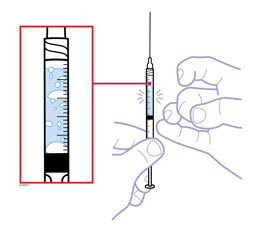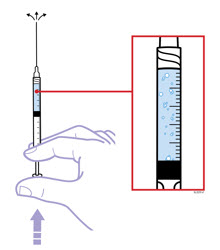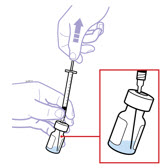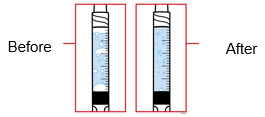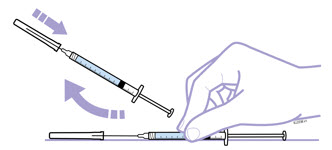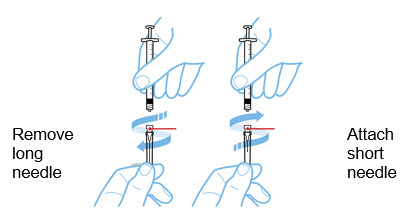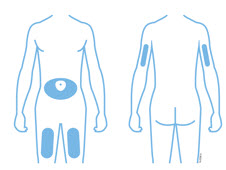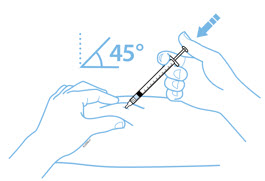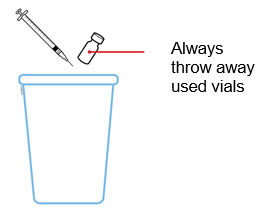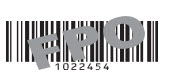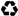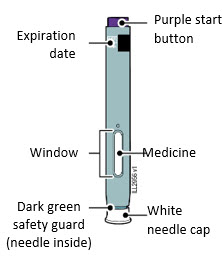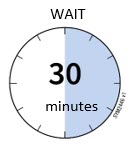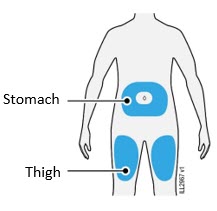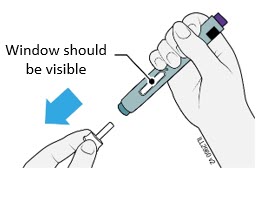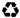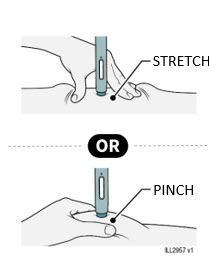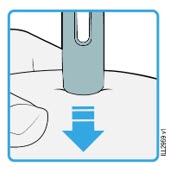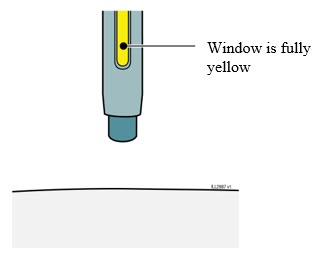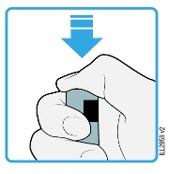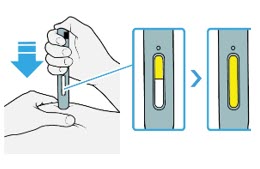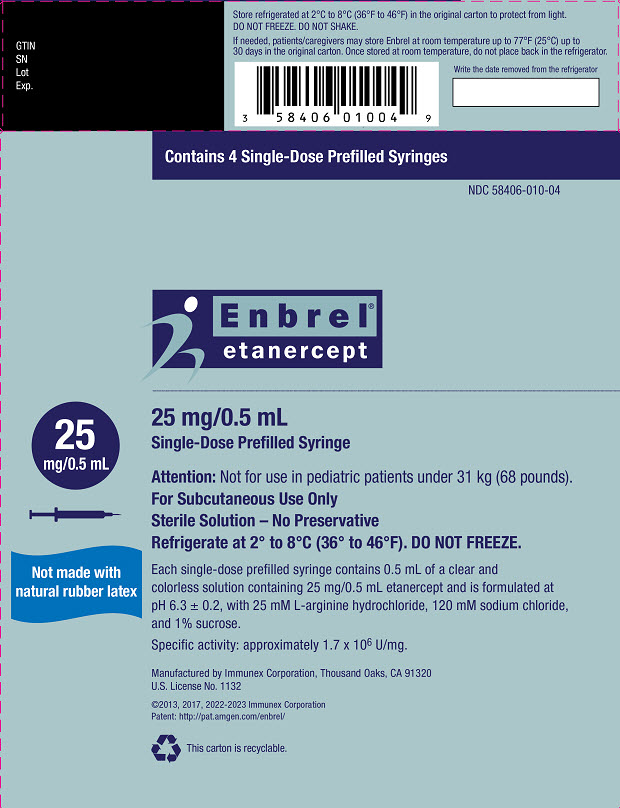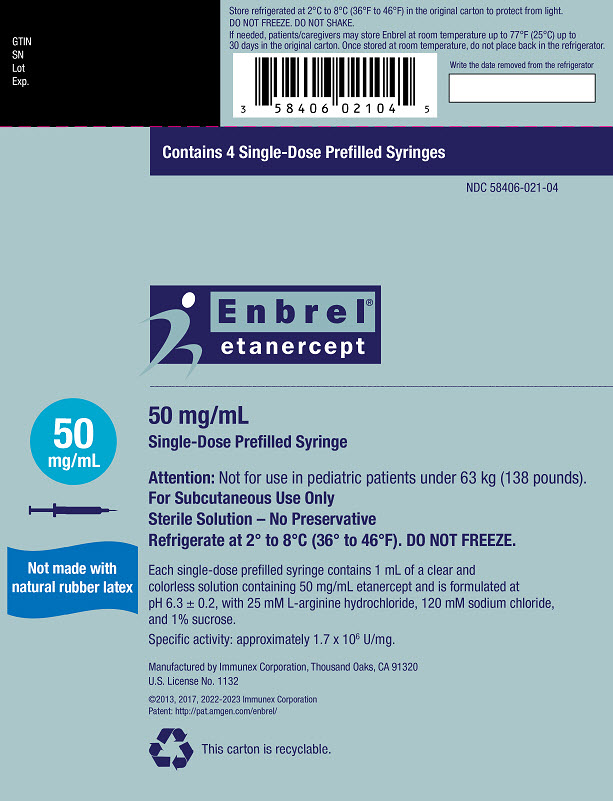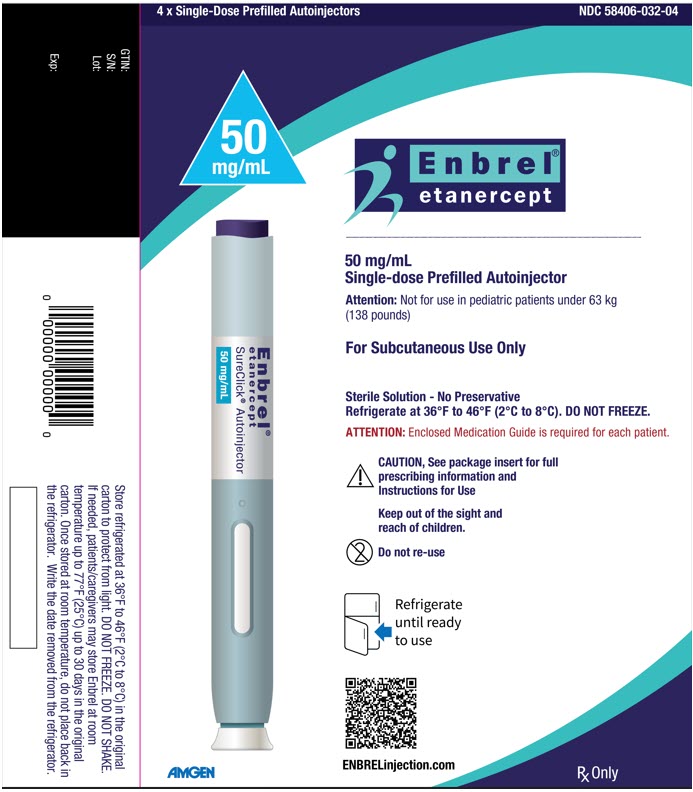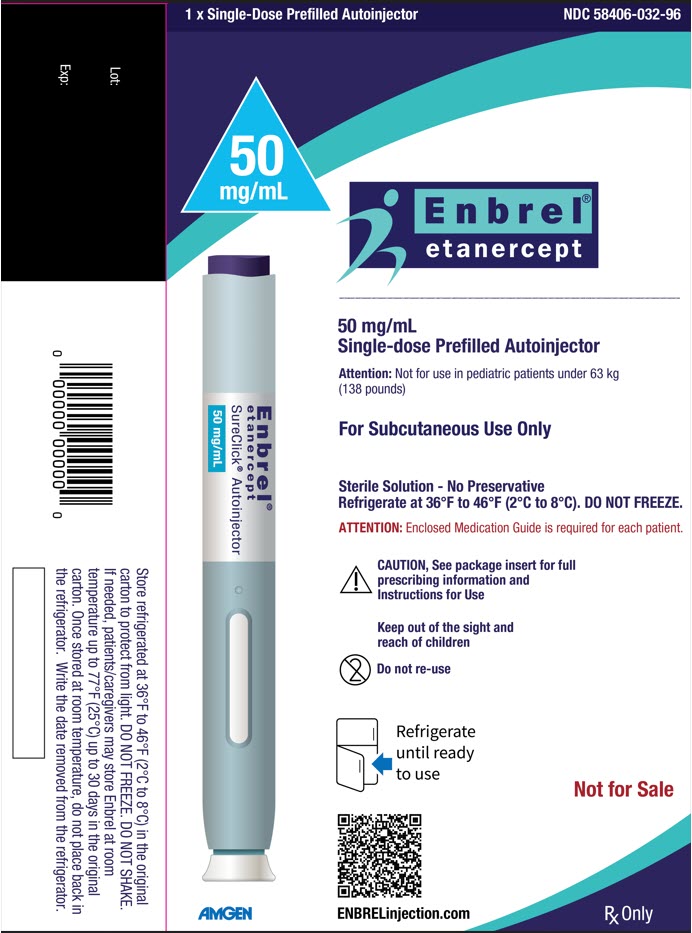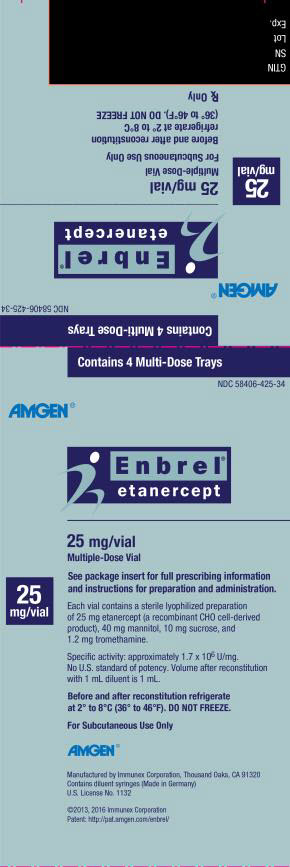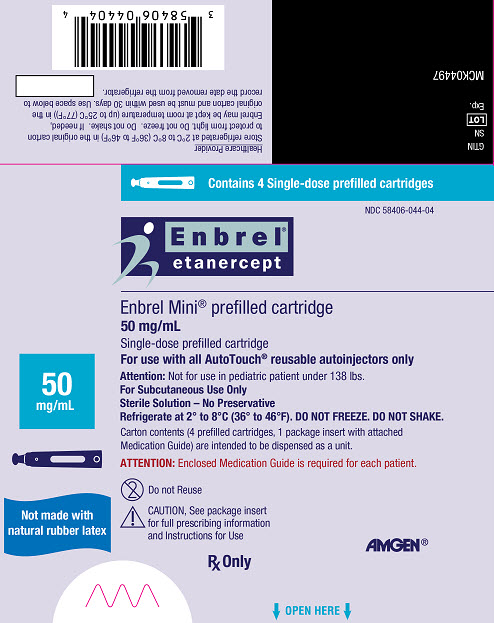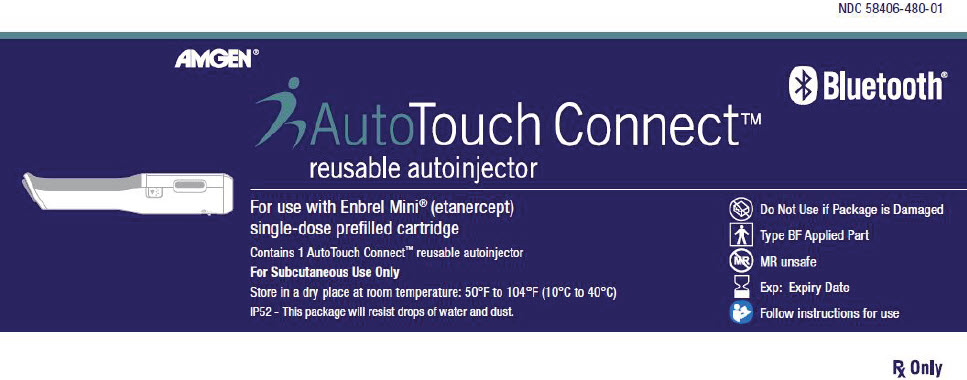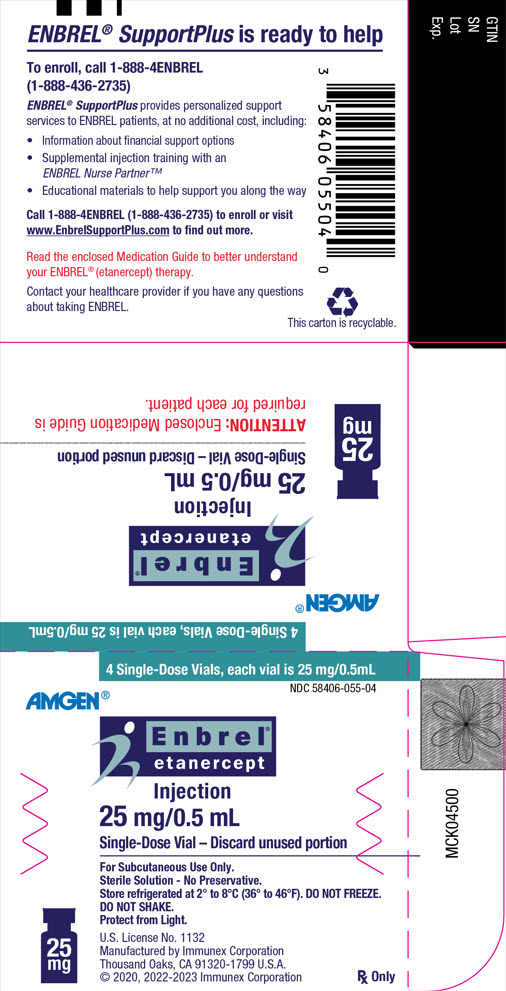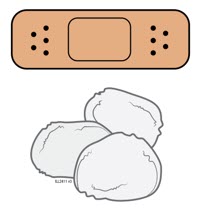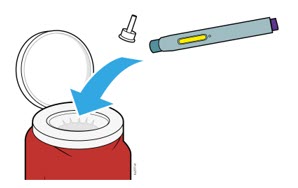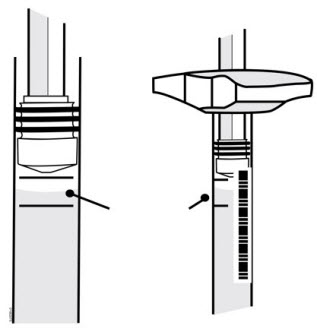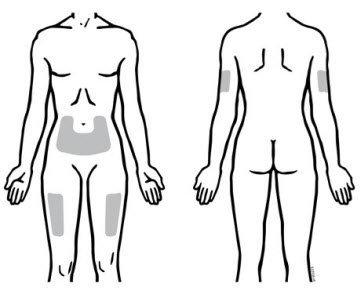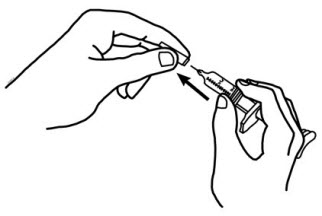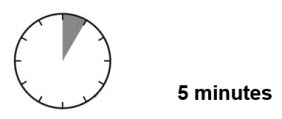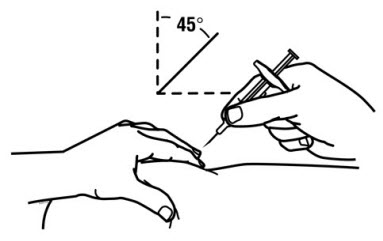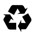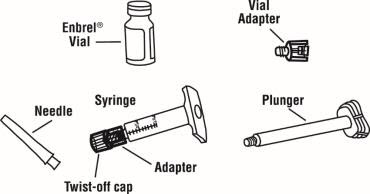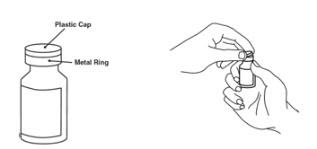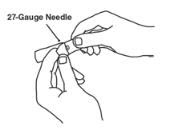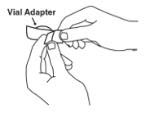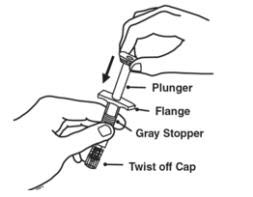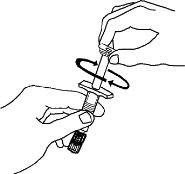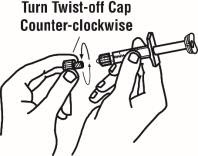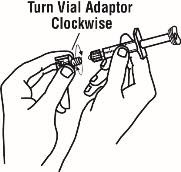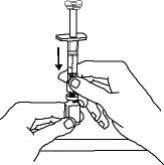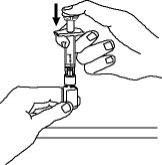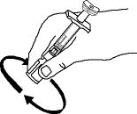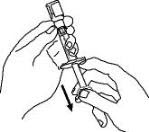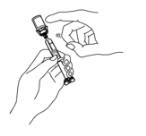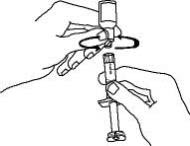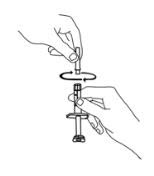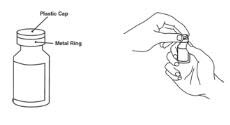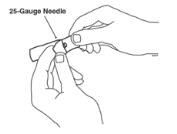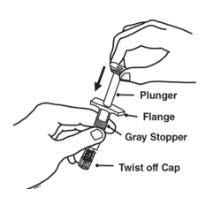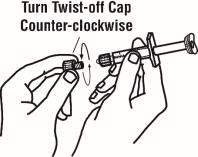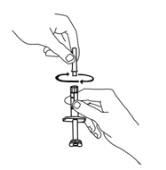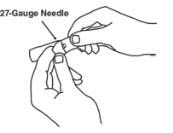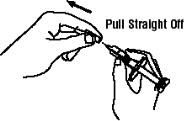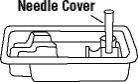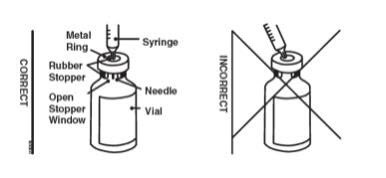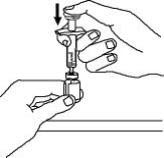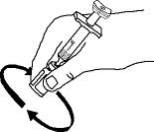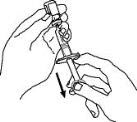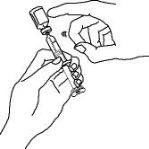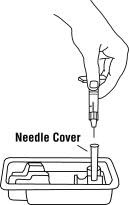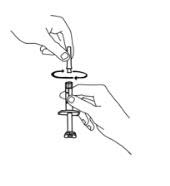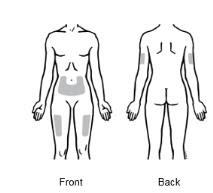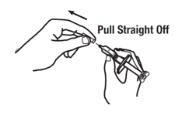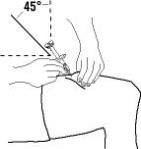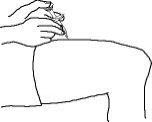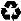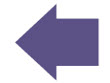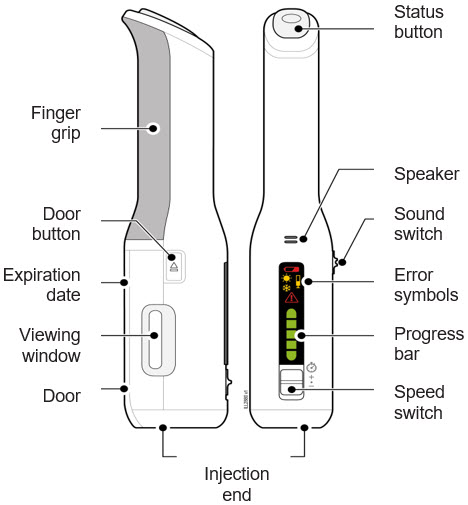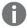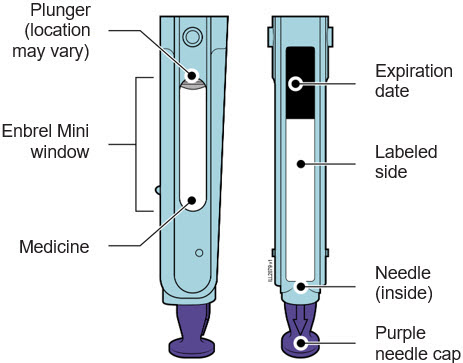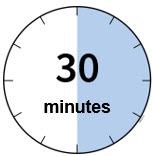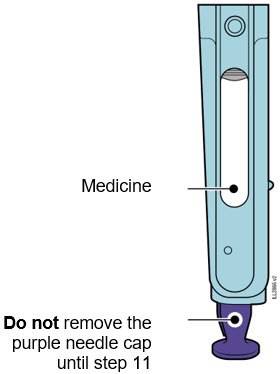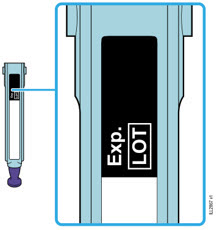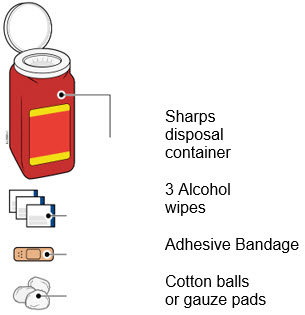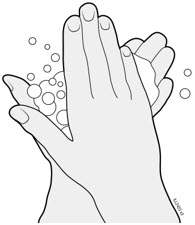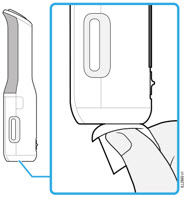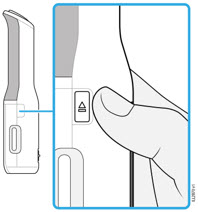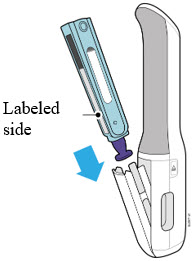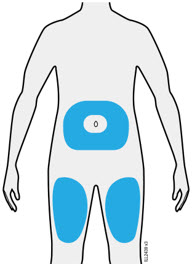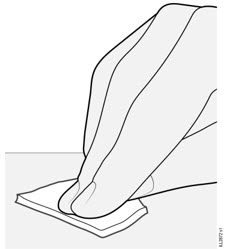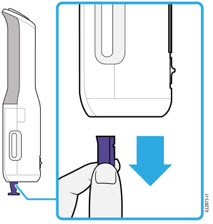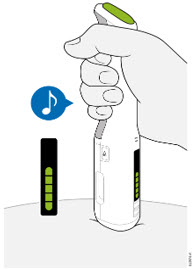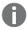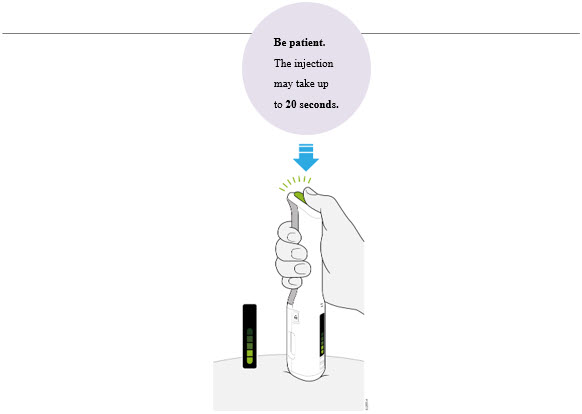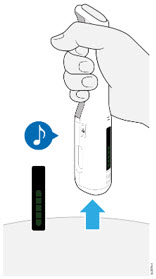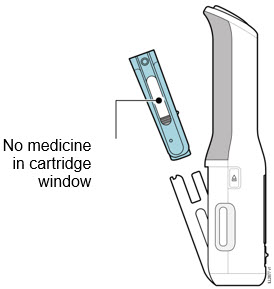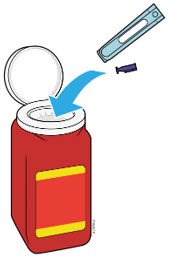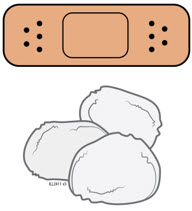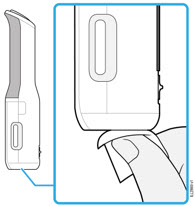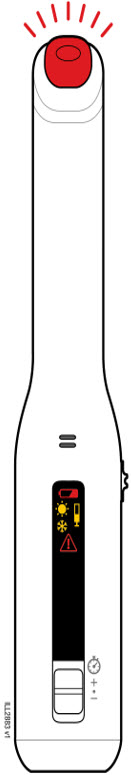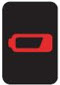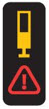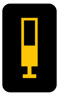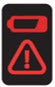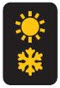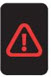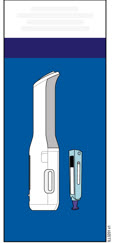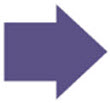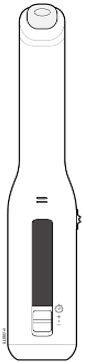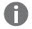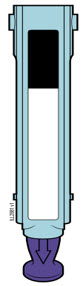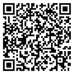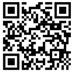 DRUG LABEL: ENBREL
NDC: 58406-425 | Form: KIT | Route: SUBCUTANEOUS
Manufacturer: Immunex Corporation
Category: prescription | Type: HUMAN PRESCRIPTION DRUG LABEL
Date: 20251209

ACTIVE INGREDIENTS: ETANERCEPT 25 mg/1 mL
INACTIVE INGREDIENTS: MANNITOL 40 mg/1 mL; SUCROSE 10 mg/1 mL; TROMETHAMINE 1.2 mg/1 mL; BENZYL ALCOHOL 9.93 mg/1 mL; WATER 1 mL/1 mL

HIGHLIGHTS OF PRESCRIBING INFORMATION

These highlights do not include all the information needed to use ENBREL safely and effectively. See full prescribing information for ENBREL.
ENBREL® (etanercept) injection, for subcutaneous use
ENBREL® (etanercept) for injection, for subcutaneous use
Initial U.S. Approval: 1998

WARNING: SERIOUS INFECTIONS and MALIGNANCIES

See full prescribing information for complete boxed warning.

SERIOUS INFECTIONS

- Increased risk of serious infections leading to hospitalization or death, including tuberculosis (TB), bacterial sepsis, invasive fungal infections (such as histoplasmosis), and infections due to other opportunistic pathogens. (5.1)
- Enbrel should be discontinued if a patient develops a serious infection or sepsis during treatment. (5.1)
- Perform test for latent TB; if positive, start treatment for TB prior to starting Enbrel. (5.1)
- Monitor all patients for active TB during treatment, even if initial latent TB test is negative. (5.1)

MALIGNANCIES

- Lymphoma and other malignancies, some fatal, have been reported in children and adolescent patients treated with TNF-blockers, including Enbrel. (5.3)

RECENT MAJOR CHANGES

Indications and Usage, Juvenile Psoriatic Arthritis (1.6) | 10/2023
Dosage and Administration, Pediatric Patients (2.4) | 10/2023

1 INDICATIONS AND USAGE

Enbrel is a tumor necrosis factor (TNF) blocker indicated for the treatment of:

Adult patients with:

- Rheumatoid Arthritis (RA) (1.1)
- Psoriatic Arthritis (PsA) (1.3)
- Ankylosing Spondylitis (AS) (1.4)
- Plaque Psoriasis (PsO) (1.5)

Pediatric patients with:

- Polyarticular Juvenile Idiopathic Arthritis (pJIA), 2 years of age or older (1.2)
- Juvenile Psoriatic Arthritis, 2 years of age or older (JPsA) (1.6)
- Plaque Psoriasis, 4 years of age or older (1.5)

2 DOSAGE AND ADMINISTRATION

Enbrel is administered by subcutaneous injection.

Patient Population | Recommended Dose and Frequency
Adult RA and PsA (2.3) | 50 mg once weekly with or without methotrexate (MTX)
AS (2.3) | 50 mg once weekly
Adult PsO (2.3) | 50 mg twice weekly for 3 months, followed by 50 mg once weekly
pJIA, Pediatric PsO and JPsA (2.4) | 0.8 mg/kg weekly, with a maximum of 50 mg per week

3 DOSAGE FORMS AND STRENGTHS

- Injection: 25 mg/0.5 mL and 50 mg/mL solution in a single-dose prefilled syringe (3)
- Injection: 50 mg/mL solution in single-dose prefilled SureClick® Autoinjector (3)
- Injection: 25 mg/0.5 mL solution in a single-dose vial (3)
- For Injection: 25 mg lyophilized powder in a multiple-dose vial for reconstitution (3)
- Injection: 50 mg/mL solution in Enbrel Mini® single-dose prefilled cartridge for use with the AutoTouch® reusable autoinjector only (3)

4 CONTRAINDICATIONS

Enbrel is contraindicated in patients with sepsis. (4)

5 WARNINGS AND PRECAUTIONS

- Do not start Enbrel during an active infection. If an infection develops, monitor carefully and stop Enbrel if infection becomes serious. (5.1)
- Consider empiric anti-fungal therapy for patients at risk for invasive fungal infections who develop a severe systemic illness on Enbrel (those who reside or travel to regions where mycoses are endemic). (5.1)
- Demyelinating disease, exacerbation or new onset, may occur. (5.2)
- Cases of lymphoma have been observed in patients receiving TNF-blocking agents. (5.3)
- Congestive heart failure, worsening or new onset, may occur. (5.4)
- Advise patients to seek immediate medical attention if symptoms of pancytopenia or aplastic anemia develop, and consider stopping Enbrel. (5.5)
- Monitor patients previously infected with hepatitis B virus for reactivation during and several months after therapy. If reactivation occurs, consider stopping Enbrel and beginning anti-viral therapy. (5.6)
- Anaphylaxis or serious allergic reactions may occur. (5.7)
- Stop Enbrel if lupus-like syndrome or autoimmune hepatitis develops. (5.9)

6 ADVERSE REACTIONS

Most common adverse reactions (incidence > 5%): infections and injection site reactions. (6.1)

To report SUSPECTED ADVERSE REACTIONS, contact Amgen Inc. at 1-800-77-AMGEN (1-800-772-6436) or FDA at 1-800-FDA-1088 or www.fda.gov/medwatch.

7 DRUG INTERACTIONS

- Live vaccines – Avoid concurrent administration with Enbrel (5.8, 7.1)
- Anakinra – Increased risk of serious infection (5.12, 7.2)
- Abatacept – Increased risk of serious adverse events, including infections (5.12, 7.2)
- Cyclophosphamide – Not recommended for use with Enbrel. (7.3)

FULL PRESCRIBING INFORMATION

WARNING: SERIOUS INFECTIONS and MALIGNANCIES

SERIOUS INFECTIONS

Patients treated with Enbrel are at increased risk for developing serious infections that may lead to hospitalization or death [see Warnings and Precautions (5.1) and Adverse Reactions (6)]. Most patients who developed these infections were taking concomitant immunosuppressants such as methotrexate or corticosteroids.

Enbrel should be discontinued if a patient develops a serious infection or sepsis.

Reported infections include:

- Active tuberculosis, including reactivation of latent tuberculosis. Patients with tuberculosis have frequently presented with disseminated or extrapulmonary disease. Test patients for latent tuberculosis before Enbrel use and during therapy. Initiate treatment for latent infection prior to Enbrel use.
- Invasive fungal infections, including histoplasmosis, coccidioidomycosis, candidiasis, aspergillosis, blastomycosis, and pneumocystosis. Patients with histoplasmosis or other invasive fungal infections may present with disseminated, rather than localized, disease. Antigen and antibody testing for histoplasmosis may be negative in some patients with active infection. Consider empiric anti-fungal therapy in patients at risk for invasive fungal infections who develop severe systemic illness.
- Bacterial, viral, and other infections due to opportunistic pathogens, including Legionella and Listeria.

The risks and benefits of treatment with Enbrel should be carefully considered prior to initiating therapy in patients with chronic or recurrent infection.

Monitor patients closely for the development of signs and symptoms of infection during and after treatment with Enbrel, including the possible development of tuberculosis in patients who tested negative for latent tuberculosis infection prior to initiating therapy.

MALIGNANCIES

Lymphoma and other malignancies, some fatal, have been reported in children and adolescent patients treated with TNF-blockers, including Enbrel.

1 INDICATIONS AND USAGE

1.1 Rheumatoid Arthritis

Enbrel is indicated for reducing signs and symptoms, inducing major clinical response, inhibiting the progression of structural damage, and improving physical function in patients with moderately to severely active rheumatoid arthritis (RA). Enbrel can be initiated in combination with methotrexate (MTX) or used alone.

1.2 Polyarticular Juvenile Idiopathic Arthritis

Enbrel is indicated for reducing signs and symptoms of moderately to severely active polyarticular juvenile idiopathic arthritis (pJIA) in patients 2 years of age and older.

1.3 Psoriatic Arthritis

Enbrel is indicated for reducing signs and symptoms, inhibiting the progression of structural damage of active arthritis, and improving physical function in adult patients with psoriatic arthritis (PsA). Enbrel can be used with or without methotrexate.

1.4 Ankylosing Spondylitis

Enbrel is indicated for reducing signs and symptoms in patients with active ankylosing spondylitis (AS).

1.5 Plaque Psoriasis

Enbrel is indicated for the treatment of patients 4 years or older with chronic moderate to severe plaque psoriasis (PsO) who are candidates for systemic therapy or phototherapy.

1.6 Juvenile Psoriatic Arthritis

Enbrel is indicated for the treatment of active juvenile psoriatic arthritis (JPsA) in pediatric patients 2 years of age and older.

2 DOSAGE AND ADMINISTRATION

2.1 Testing and Procedures Prior to Treatment Initiation

Perform the following evaluations and procedures prior to initiating treatment with Enbrel:

- Prior to initiating Enbrel and periodically during therapy, evaluate patients for active tuberculosis and test for latent infection [see Warnings and Precautions (5.1)].
- Complete all age-appropriate vaccinations as recommended by current immunization guidelines prior to initiating treatment with Enbrel [see Warnings and Precautions (5.8)].

2.2 Important Administration Instructions

Administration of one 50 mg Enbrel single-dose prefilled syringe, one single-dose prefilled Enbrel SureClick autoinjector, or one Enbrel Mini single-dose prefilled cartridge (for use with the AutoTouch reusable autoinjector only), provides a dose equivalent to two 25 mg Enbrel single-dose prefilled syringes, two 25 mg single-dose vials, or two multiple-dose vials of lyophilized Enbrel, when multiple-dose vials are reconstituted and administered as recommended.

2.3 Recommended Dosage in Adult Patients with Rheumatoid Arthritis, Ankylosing Spondylitis, Psoriatic Arthritis, and Plaque Psoriasis

Enbrel is administered by subcutaneous injection (Table 1).

Table 1. Recommended Dosage for Adult Patients with RA, AS, PsA and PsO
Patient Population | Recommended Dosage
Adult RA, AS, and PsA | 50 mg weekly
Adult PsO | Starting Dose: 50 mg twice weekly for 3 months Maintenance Dose: 50 mg once weekly

See the Enbrel (etanercept) "Instructions for Use" insert for detailed information on injection site selection and dose administration [see Dosage and Administration (2.3) and Patient Counseling Information (17)].

Adult Rheumatoid Arthritis, Ankylosing Spondylitis, and Psoriatic Arthritis Patients

Methotrexate, glucocorticoids, salicylates, nonsteroidal anti-inflammatory drugs (NSAIDs), or analgesics may be continued during treatment with Enbrel.

Based on a study of 50 mg Enbrel twice weekly in patients with RA that suggested higher incidence of adverse reactions but similar American College of Rheumatology (ACR) response rates, doses higher than 50 mg per week are not recommended.

Adult Plaque Psoriasis Patients

In addition to the 50 mg twice weekly recommended starting dose, starting doses of 25 mg or 50 mg per week were shown to be efficacious. The proportion of responders was related to Enbrel dosage [see Clinical Studies (14.5)].

2.4 Recommended Dosage for Pediatric Patients with Polyarticular Juvenile Idiopathic Arthritis, Plaque Psoriasis, and Juvenile Psoriatic Arthritis

The recommended weight-based dosage for pediatric patients is administered by subcutaneous injection (Table 2).

Table 2. Recommended Dosage for Pediatric Patients with pJIA, PsO and JPsA
Body Weight | Recommended Dosage
63 kg (138 pounds) or more | 50 mg weekly
Less than 63 kg (138 pounds) | 0.8 mg/kg weekly

To achieve pediatric doses other than 25 mg or 50 mg, use Enbrel solution in a single-dose vial or reconstituted lyophilized powder in a multiple-dose vial.

Dosages of Enbrel higher than those described in Table 2 have not been studied in pediatric patients.

In pJIA patients, glucocorticoids, NSAIDs, or analgesics may be continued during treatment with Enbrel.

2.5 Preparation Instructions for Enbrel

Enbrel is intended for use under the guidance and supervision of a physician. Patients may self-inject when deemed appropriate and if they receive medical follow-up, as necessary. Patients should not self-administer until they receive proper training in how to prepare and administer the correct dose. Administer injections subcutaneously in the thigh, abdomen or outer area of the upper arm.

The Enbrel devices are not made with natural rubber latex.

The Enbrel (etanercept) "Instructions for Use" insert for each presentation contains more detailed instructions on injection site selection and the preparation of Enbrel.

Preparation of Enbrel Single-dose Prefilled Syringe

For a more comfortable injection, leave Enbrel prefilled syringes at room temperature for about 15 to 30 minutes before injecting. DO NOT remove the needle cover while allowing the prefilled syringe to reach room temperature.

Inspect visually for particulate matter and discoloration prior to administration. There may be small white particles of protein in the solution. This is not unusual for proteinaceous solutions. The solution should not be used if discolored or cloudy, or if foreign particulate matter is present.

When using the Enbrel single-dose prefilled syringe, check to see if the amount of liquid in the prefilled syringe falls between the two purple fill level indicator lines on the syringe. If the syringe does not have the right amount of liquid, DO NOT USE THAT SYRINGE.

Preparation of Enbrel Single-dose Prefilled SureClick Autoinjector

Leave the autoinjector at room temperature for at least 30 minutes before injecting. DO NOT remove the needle cover while allowing the prefilled syringe to reach room temperature.

Inspect visually for particulate matter and discoloration prior to administration. There may be small white particles of protein in the solution. This is not unusual for proteinaceous solutions. The solution should not be used if discolored or cloudy, or if foreign particulate matter is present.

Preparation of Enbrel Single-dose Vial

For a more comfortable injection, leave Enbrel vial(s) at room temperature for at least 30 minutes before injecting. DO NOT remove the vial cap while allowing the vial to reach room temperature.

Inspect visually for particulate matter and discoloration prior to administration. There may be small white particles of protein in the solution. This is not unusual for proteinaceous solutions. The solution should not be used if discolored or cloudy, or if foreign particulate matter is present.

When using the Enbrel single-dose vial, administer the correct dose of solution using the following recommended materials:

- A 1 mL Luer-Lock syringe.
- A withdrawal needle with Luer-Lock connection, sterile, 22-gauge, length 1 ½ inch.
- An injection needle with Luer-Lock connection, sterile, 27-gauge, length ½ inch.

Two vials may be required to administer the total prescribed dose. Use the same syringe for each vial. The vial does not contain preservatives; therefore, discard unused portions.

Preparation of Enbrel Lyophilized Powder in a Multiple-dose Vial

Enbrel lyophilized powder should be reconstituted aseptically with 1 mL of the supplied Sterile Bacteriostatic Water for Injection, USP (0.9% benzyl alcohol), giving a solution of 1 mL containing 25 mg of Enbrel.

A vial adapter is supplied for use when reconstituting the lyophilized powder. However, the vial adapter should not be used if multiple doses are going to be withdrawn from the vial. If the vial will be used for multiple doses, a 25-gauge needle should be used for reconstituting and withdrawing Enbrel, and the supplied "Mixing Date:" sticker should be attached to the vial and the date of reconstitution entered. Reconstituted solution must be refrigerated at 36°F to 46°F (2°C to 8°C) and used within 14 days. Discard reconstituted solution after 14 days because product stability and sterility cannot be assured after 14 days. DO NOT store reconstituted Enbrel solution at room temperature.

For a more comfortable injection, leave the Enbrel dose tray at room temperature for about 15 to 30 minutes before injecting.

If using the vial adapter, twist the vial adapter onto the diluent syringe. Then, place the vial adapter over the Enbrel vial and insert the vial adapter into the vial stopper. Push down on the plunger to inject the diluent into the Enbrel vial. If using a 25-gauge needle to reconstitute and withdraw Enbrel, the diluent should be injected very slowly into the Enbrel vial. It is normal for some foaming to occur. Keeping the diluent syringe in place, gently swirl the contents of the Enbrel vial during dissolution. To avoid excessive foaming, do not shake or vigorously agitate.

Generally, dissolution of Enbrel takes less than 10 minutes. Do not use the solution if discolored or cloudy, or if particulate matter remains.

Withdraw the correct dose of reconstituted solution into the syringe. Some foam or bubbles may remain in the vial. Remove the syringe from the vial adapter or remove the 25-gauge needle from the syringe. Attach a 27-gauge needle to inject Enbrel.

The contents of one vial of Enbrel solution should not be mixed with, or transferred into, the contents of another vial of Enbrel. No other medications should be added to solutions containing Enbrel, and do not reconstitute Enbrel with other diluents. Do not filter reconstituted solution during preparation or administration.

Preparation of Enbrel Mini® single-dose prefilled cartridge using the AutoTouch® reusable autoinjector

Leave Enbrel Mini single-dose prefilled cartridge at room temperature for at least 30 minutes before injecting. DO NOT remove the purple cap while allowing the cartridge to reach room temperature.

Parenteral drug products should be inspected visually for particulate matter and discoloration prior to administration. There may be small white particles of protein in the solution. This is not unusual for proteinaceous solutions. The solution should not be used if discolored or cloudy, or if foreign particulate matter is present.

To use AutoTouch reusable autoinjector, open the door by pushing the door button and inserting Enbrel Mini single-dose prefilled cartridge into AutoTouch. When inserted correctly, Enbrel Mini single-dose prefilled cartridge will slide freely and completely into the door. Close the door and AutoTouch reusable autoinjector is ready for injection.

3 DOSAGE FORMS AND STRENGTHS

- Injection: 25 mg/0.5 mL and 50 mg/mL clear, colorless solution in a single-dose prefilled syringe
- Injection: 50 mg/mL clear, colorless solution in a single-dose prefilled SureClick autoinjector
- Injection: 25 mg/0.5 mL clear, colorless solution in a single-dose vial
- For Injection: 25 mg lyophilized powder in a multiple-dose vial for reconstitution
- Injection: 50 mg/mL clear, colorless solution in Enbrel Mini single-dose prefilled cartridge for use with the AutoTouch reusable autoinjector only

4 CONTRAINDICATIONS

Enbrel is contraindicated in patients with sepsis.

5 WARNINGS AND PRECAUTIONS

5.1 Serious Infections

Patients treated with Enbrel are at increased risk for developing serious infections involving various organ systems and sites that may lead to hospitalization or death.

Opportunistic infections due to bacterial, mycobacterial, invasive fungal, viral, parasitic, or other opportunistic pathogens including aspergillosis, blastomycosis, candidiasis, coccidioidomycosis, histoplasmosis, legionellosis, listeriosis, pneumocystosis, and tuberculosis have been reported with TNF-blockers. Patients have frequently presented with disseminated rather than localized disease.

Treatment with Enbrel should not be initiated in patients with an active infection, including clinically important localized infections. Patients greater than 65 years of age, patients with co-morbid conditions, and/or patients taking concomitant immunosuppressants (such as corticosteroids or methotrexate), may be at greater risk of infection. The risks and benefits of treatment should be considered prior to initiating therapy in patients:

- With chronic or recurrent infection;
- Who have been exposed to tuberculosis;
- With a history of an opportunistic infection;
- Who have resided or traveled in areas of endemic tuberculosis or endemic mycoses, such as histoplasmosis, coccidioidomycosis, or blastomycosis; or
- With underlying conditions that may predispose them to infection, such as advanced or poorly controlled diabetes [see Adverse Reactions (6.1)].

Patients should be closely monitored for the development of signs and symptoms of infection during and after treatment with Enbrel.

Enbrel should be discontinued if a patient develops a serious infection or sepsis. A patient who develops a new infection during treatment with Enbrel should be closely monitored, undergo a prompt and complete diagnostic workup appropriate for an immunocompromised patient, and appropriate antimicrobial therapy should be initiated.

Tuberculosis

Cases of reactivation of tuberculosis or new tuberculosis infections have been observed in patients receiving Enbrel, including patients who have previously received treatment for latent or active tuberculosis. Data from clinical trials and preclinical studies suggest that the risk of reactivation of latent tuberculosis infection is lower with Enbrel than with TNF-blocking monoclonal antibodies. Nonetheless, postmarketing cases of tuberculosis reactivation have been reported for TNF-blockers, including Enbrel. Tuberculosis has developed in patients who tested negative for latent tuberculosis prior to initiation of therapy. Patients should be evaluated for tuberculosis risk factors and tested for latent infection prior to initiating Enbrel and periodically during therapy. Tests for latent tuberculosis infection may be falsely negative while on therapy with Enbrel.

Treatment of latent tuberculosis infection prior to therapy with TNF-blocking agents has been shown to reduce the risk of tuberculosis reactivation during therapy. Induration of 5 mm or greater with tuberculin skin testing should be considered a positive test result when assessing if treatment for latent tuberculosis is needed prior to initiating Enbrel, even for patients previously vaccinated with Bacillus Calmette-Guerin (BCG).

Anti-tuberculosis therapy should also be considered prior to initiation of Enbrel in patients with a past history of latent or active tuberculosis in whom an adequate course of treatment cannot be confirmed, and for patients with a negative test for latent tuberculosis but having risk factors for tuberculosis infection. Consultation with a physician with expertise in the treatment of tuberculosis is recommended to aid in the decision whether initiating anti-tuberculosis therapy is appropriate for an individual patient.

Tuberculosis should be strongly considered in patients who develop a new infection during Enbrel treatment, especially in patients who have previously or recently traveled to countries with a high prevalence of tuberculosis, or who have had close contact with a person with active tuberculosis.

Invasive Fungal Infections

Cases of serious and sometimes fatal fungal infections, including histoplasmosis, have been reported with TNF-blockers, including Enbrel. For patients who reside or travel in regions where mycoses are endemic, invasive fungal infection should be suspected if they develop a serious systemic illness. Appropriate empiric anti-fungal therapy should be considered while a diagnostic workup is being performed. Antigen and antibody testing for histoplasmosis may be negative in some patients with active infection. When feasible, the decision to administer empiric anti-fungal therapy in these patients should be made in consultation with a physician with expertise in the diagnosis and treatment of invasive fungal infections and should take into account both the risk for severe fungal infection and the risks of anti-fungal therapy. In 38 Enbrel clinical trials and 4 cohort studies in all approved indications representing 27,169 patient-years of exposure (17,696 patients) from the United States and Canada, no histoplasmosis infections were reported among patients treated with Enbrel.

5.2 Neurologic Reactions

Treatment with TNF-blocking agents, including Enbrel, has been associated with rare (< 0.1%) cases of new onset or exacerbation of central nervous system demyelinating disorders, some presenting with mental status changes and some associated with permanent disability, and with peripheral nervous system demyelinating disorders. Cases of transverse myelitis, optic neuritis, multiple sclerosis, Guillain-Barre syndromes, other peripheral demyelinating neuropathies, and new onset or exacerbation of seizure disorders have been reported in postmarketing experience with Enbrel therapy. Prescribers should exercise caution in considering the use of Enbrel in patients with preexisting or recent-onset central or peripheral nervous system demyelinating disorders [see Postmarketing Experience (6.3)].

5.3 Malignancies

Lymphomas

In the controlled portions of clinical trials of TNF-blocking agents, more cases of lymphoma have been observed among patients receiving a TNF-blocker compared to control patients. During the controlled portions of Enbrel trials in adult patients with RA, AS, and PsA, 2 lymphomas were observed among 3306 Enbrel-treated patients versus 0 among 1521 control patients (duration of controlled treatment ranged from 3 to 36 months).

Among 6543 adult rheumatology (RA, PsA, AS) patients treated with Enbrel in controlled and uncontrolled portions of clinical trials, representing approximately 12,845 patient-years of therapy, the observed rate of lymphoma was 0.10 cases per 100 patient-years. This was 3-fold higher than the rate of lymphoma expected in the general U.S. population based on the Surveillance, Epidemiology, and End Results (SEER) Database. An increased rate of lymphoma up to several-fold has been reported in the RA patient population, and may be further increased in patients with more severe disease activity.

Among 4410 adult PsO patients treated with Enbrel in clinical trials up to 36 months, representing approximately 4278 patient-years of therapy, the observed rate of lymphoma was 0.05 cases per 100 patient-years, which is comparable to the rate in the general population. No cases were observed in Enbrel- or placebo-treated patients during the controlled portions of these trials.

Leukemia

Cases of acute and chronic leukemia have been reported in association with postmarketing TNF-blocker use in rheumatoid arthritis and other indications. Even in the absence of TNF-blocker therapy, patients with rheumatoid arthritis may be at higher risk (approximately 2-fold) than the general population for the development of leukemia.

During the controlled portions of Enbrel trials, 2 cases of leukemia were observed among 5445 (0.06 cases per 100 patient-years) Enbrel-treated patients versus 0 among 2890 (0%) control patients (duration of controlled treatment ranged from 3 to 48 months).

Among 15,401 patients treated with Enbrel in controlled and open portions of clinical trials representing approximately 23,325 patient-years of therapy, the observed rate of leukemia was 0.03 cases per 100 patient-years.

Other Malignancies

Information is available from 10,953 adult patients with 17,123 patient-years and 696 pediatric patients with 1282 patient-years of experience across 45 Enbrel clinical studies.

For malignancies other than lymphoma and non-melanoma skin cancer, there was no difference in exposure-adjusted rates between the Enbrel and control arms in the controlled portions of clinical studies for all indications. Analysis of the malignancy rate in combined controlled and uncontrolled portions of studies has demonstrated that types and rates are similar to what is expected in the general U.S. population based on the SEER database and suggests no increase in rates over time. Whether treatment with Enbrel might influence the development and course of malignancies in adults is unknown.

Melanoma and Non-Melanoma Skin Cancer (NMSC)

Melanoma and non-melanoma skin cancer has been reported in patients treated with TNF antagonists including etanercept.

Among 15,401 patients treated with Enbrel in controlled and open portions of clinical trials representing approximately 23,325 patient-years of therapy, the observed rate of melanoma was 0.043 cases per 100 patient-years.

Among 3306 adult rheumatology (RA, PsA, AS) patients treated with Enbrel in controlled clinical trials representing approximately 2669 patient-years of therapy, the observed rate of NMSC was 0.41 cases per 100 patient-years versus 0.37 cases per 100 patient-years among 1521 control-treated patients representing 1077 patient-years. Among 1245 adult PsO patients treated with Enbrel in controlled clinical trials, representing approximately 283 patient-years of therapy, the observed rate of NMSC was 3.54 cases per 100 patient-years versus 1.28 cases per 100 patient-years among 720 control-treated patients representing 156 patient-years.

Postmarketing cases of Merkel cell carcinoma have been reported very infrequently in patients treated with Enbrel.

Periodic skin examinations should be considered for all patients at increased risk for skin cancer.

Pediatric Patients

Malignancies, some fatal, have been reported among children, adolescents, and young adults who received treatment with TNF-blocking agents (initiation of therapy at ≤ 18 years of age), including Enbrel. Approximately half the cases were lymphomas, including Hodgkin's and non-Hodgkin's lymphoma. The other cases represented a variety of different malignancies and included rare malignancies usually associated with immunosuppression and malignancies that are not usually observed in children and adolescents. The malignancies occurred after a median of 30 months of therapy (range 1 to 84 months). Most of the patients were receiving concomitant immunosuppressants. These cases were reported postmarketing and are derived from a variety of sources, including registries and spontaneous postmarketing reports.

In clinical trials of 1140 pediatric patients representing 1927.2 patient-years of therapy, no malignancies, including lymphoma or NMSC, have been reported.

Postmarketing Use

In global postmarketing adult and pediatric use, lymphoma and other malignancies have been reported.

5.4 New Onset or Worsening of Heart Failure

Two clinical trials evaluating the use of Enbrel in the treatment of heart failure were terminated early due to lack of efficacy. One of these studies suggested higher mortality in Enbrel-treated patients compared to placebo [see Adverse Reactions (6.2)]. There have been postmarketing reports of worsening of congestive heart failure (CHF), with and without identifiable precipitating factors, in patients taking Enbrel. There have also been rare (< 0.1%) reports of new onset CHF, including CHF in patients without known preexisting cardiovascular disease. Some of these patients have been under 50 years of age. Physicians should exercise caution when using Enbrel in patients who also have heart failure, and monitor patients carefully.

5.5 Hematologic Reactions

Rare (< 0.1%) reports of pancytopenia, including very rare (< 0.01%) reports of aplastic anemia, some with a fatal outcome, have been reported in patients treated with Enbrel. The causal relationship to Enbrel therapy remains unclear. Although no high-risk group has been identified, caution should be exercised in patients being treated with Enbrel who have a previous history of significant hematologic abnormalities. All patients should be advised to seek immediate medical attention if they develop signs and symptoms suggestive of blood dyscrasias or infection (e.g., persistent fever, bruising, bleeding, pallor) while on Enbrel. Discontinuation of Enbrel therapy should be considered in patients with confirmed significant hematologic abnormalities.

Two percent of patients treated concurrently with Enbrel and anakinra developed neutropenia (ANC < 1 × 10^9/L). While neutropenic, one patient developed cellulitis that resolved with antibiotic therapy.

5.6 Hepatitis B Reactivation

Reactivation of hepatitis B in patients who were previously infected with the hepatitis B virus (HBV) and had received concomitant TNF-blocking agents, including very rare cases (< 0.01%) with Enbrel, has been reported. In some instances, hepatitis B reactivation occurring in conjunction with TNF-blocker therapy has been fatal. The majority of these reports have occurred in patients concomitantly receiving other medications that suppress the immune system, which may also contribute to hepatitis B reactivation. Patients at risk for HBV infection should be evaluated for prior evidence of HBV infection before initiating TNF-blocker therapy. Prescribers should exercise caution in prescribing TNF-blockers in patients previously infected with HBV. Adequate data are not available on the safety or efficacy of treating patients who are carriers of HBV with anti-viral therapy in conjunction with TNF-blocker therapy to prevent HBV reactivation. Patients previously infected with HBV and requiring treatment with Enbrel should be closely monitored for clinical and laboratory signs of active HBV infection throughout therapy and for several months following termination of therapy. In patients who develop HBV reactivation, consideration should be given to stopping Enbrel and initiating anti-viral therapy with appropriate supportive treatment. The safety of resuming Enbrel therapy after HBV reactivation is controlled is not known. Therefore, prescribers should weigh the risks and benefits when considering resumption of therapy in this situation.

5.7 Allergic Reactions

Allergic reactions associated with administration of Enbrel during clinical trials have been reported in < 2% of patients. If an anaphylactic reaction or other serious allergic reaction occurs, discontinue administration of Enbrel and initiate appropriate therapy immediately.

5.8 Immunizations

Avoid concurrent administration of live vaccines with Enbrel. It is recommended that patients, if possible, be brought up-to-date with all immunizations in agreement with current immunization guidelines prior to initiating Enbrel therapy [see Drug Interactions (7.1) and Use in Specific Populations (8.4)].

5.9 Autoimmunity

Treatment with Enbrel may result in the formation of autoantibodies [see Adverse Reactions (6.1)] and, rarely (< 0.1%), in the development of a lupus-like syndrome or autoimmune hepatitis [see Adverse Reactions (6.2)], which may resolve following withdrawal of Enbrel. If a patient develops symptoms and findings suggestive of a lupus-like syndrome or autoimmune hepatitis following treatment with Enbrel, discontinue treatment and evaluate the patient.

5.10 Immunosuppression

TNF mediates inflammation and modulates cellular immune responses. TNF-blocking agents, including Enbrel, affect host defenses against infections. The effect of TNF inhibition on the development and course of malignancies is not fully understood. In a study of 49 patients with RA treated with Enbrel, there was no evidence of depression of delayed-type hypersensitivity, depression of immunoglobulin levels, or change in enumeration of effector cell populations [see Warnings and Precautions (5.1, 5.3) and Adverse Reactions (6.1)].

5.11 Not Recommended for Use in Patients with Granulomatosis with Polyangiitis Receiving Immunosuppressants

The use of Enbrel in patients with granulomatosis with polyangiitis receiving immunosuppressive agents is not recommended. In a study of patients with granulomatosis with polyangiitis, the addition of Enbrel to standard therapy (including cyclophosphamide) was associated with a higher incidence of non-cutaneous solid malignancies and was not associated with improved clinical outcomes when compared with standard therapy alone [see Drug Interactions (7.3)].

5.12 Not Recommended for Use with Anakinra or Abatacept

Use of Enbrel with anakinra or abatacept is not recommended [see Drug Interactions (7.2)].

5.13 Increased Mortality in Patients with Moderate to Severe Alcoholic Hepatitis

In a study of 48 hospitalized patients treated with Enbrel or placebo for moderate to severe alcoholic hepatitis, the mortality rate in patients treated with Enbrel was similar to patients treated with placebo at 1 month but significantly higher after 6 months. Physicians should use caution when using Enbrel in patients with moderate to severe alcoholic hepatitis.

6 ADVERSE REACTIONS

The following serious adverse reactions are discussed in greater detail in other sections of the labeling:

- Serious Infections [see Warnings and Precautions (5.1)]
- Neurologic Reactions [see Warnings and Precautions (5.2)]
- Malignancies [see Warnings and Precautions (5.3)]
- Patients with Heart Failure [see Warnings and Precautions (5.4)]
- Hematologic Reactions [see Warnings and Precautions (5.5)]
- Hepatitis B Reactivation [see Warnings and Precautions (5.6)]
- Allergic Reactions [see Warnings and Precautions (5.7)]
- Autoimmunity [see Warnings and Precautions (5.9)]
- Immunosuppression [see Warnings and Precautions (5.10)]

6.1 Clinical Trials Experience

Across clinical studies and postmarketing experience, the most serious adverse reactions with Enbrel were infections, neurologic events, CHF, and hematologic events [see Warnings and Precautions (5)]. The most common adverse reactions with Enbrel were infections and injection site reactions.

Because clinical trials are conducted under widely varying conditions, adverse reactions rates observed in the clinical trials of a drug cannot be directly compared to rates in the clinical trials of another drug and may not predict the rates observed in clinical practice.

Adverse Reactions in Adult Patients with Rheumatoid Arthritis, Psoriatic Arthritis, Ankylosing Spondylitis, or Plaque Psoriasis

The data described below reflect exposure to Enbrel in 2219 adult patients with RA followed for up to 80 months, in 182 patients with PsA for up to 24 months, in 138 patients with AS for up to 6 months, and in 1204 adult patients with PsO for up to 18 months.

In controlled trials, the proportion of Enbrel-treated patients who discontinued treatment due to adverse events was approximately 4% in the indications studied.

Adverse Reactions in Pediatric Patients

In general, the adverse reactions in pediatric patients were similar in frequency and type as those seen in adult patients [see Warnings and Precautions (5), Use in Specific Populations (8.4), and Clinical Studies (14.2, 14.6)].

In a 48-week clinical study in 211 children aged 4 to 17 years with pediatric PsO, the adverse reactions reported were similar to those seen in previous studies in adults with PsO. Long-term safety profile for up to 264 additional weeks was assessed in an open-label extension study and no new safety signals were identified.

In open-label clinical studies of children with JIA, adverse reactions reported in those ages 2 to 4 years were similar to adverse reactions reported in older children.

Infections

Infections, including viral, bacterial, and fungal infections, have been observed in adult and pediatric patients. Infections have been noted in all body systems and have been reported in patients receiving Enbrel alone or in combination with other immunosuppressive agents.

In controlled portions of trials, the types and severity of infection were similar between Enbrel and the respective control group (placebo or MTX for RA and PsA patients) in RA, PsA, AS and PsO patients. Rates of infections in RA and adult PsO patients are provided in Table 3 and Table 4, respectively. Infections consisted primarily of upper respiratory tract infection, sinusitis and influenza.

In controlled portions of trials in RA, PsA, AS and PsO, the rates of serious infection were similar (0.8% in placebo, 3.6% in MTX, and 1.4% in Enbrel/Enbrel + MTX-treated groups). In clinical trials in rheumatologic indications, serious infections experienced by patients have included, but are not limited to, pneumonia, cellulitis, septic arthritis, bronchitis, gastroenteritis, pyelonephritis, sepsis, abscess and osteomyelitis. In clinical trials in adult PsO patients, serious infections experienced by patients have included, but are not limited to, pneumonia, cellulitis, gastroenteritis, abscess and osteomyelitis. The rate of serious infections was not increased in open-label extension trials and was similar to that observed in Enbrel- and placebo-treated patients from controlled trials.

In 66 global clinical trials of 17,505 patients (21,015 patient-years of therapy), tuberculosis was observed in approximately 0.02% of patients. In 17,696 patients (27,169 patient-years of therapy) from 38 clinical trials and 4 cohort studies in the U.S. and Canada, tuberculosis was observed in approximately 0.006% of patients. These studies include reports of pulmonary and extrapulmonary tuberculosis [see Warnings and Precautions (5.1)].

The types of infections reported in pediatric patients with PsO and JIA were generally mild and consistent with those commonly seen in the general pediatric population. Two JIA patients developed varicella infection and signs and symptoms of aseptic meningitis, which resolved without sequelae.

Injection Site Reactions

In placebo-controlled trials in rheumatologic indications, approximately 37% of patients treated with Enbrel developed injection site reactions. In controlled trials in patients with PsO, 15% of adult patients and 7% of pediatric patients treated with Enbrel developed injection site reactions during the first 3 months of treatment. All injection site reactions were described as mild to moderate (erythema, itching, pain, swelling, bleeding, bruising) and generally did not necessitate drug discontinuation. Injection site reactions generally occurred in the first month and subsequently decreased in frequency. The mean duration of injection site reactions was 3 to 5 days. Seven percent of patients experienced redness at a previous injection site when subsequent injections were given.

Other Adverse Reactions

Table 3 summarizes adverse reactions reported in adult RA patients. The types of adverse reactions seen in patients with PsA or AS were similar to the types of adverse reactions seen in patients with RA.

Table 3. Percent of Adult RA Patients Experiencing Adverse Reactions in Controlled Clinical Trials
 | Placebo-Controlled [Includes data from the 6-month study in which patients received concurrent MTX therapy in both arms.] (Studies I, II, and a Phase 2 Study) |  | Active-Controlled [Study duration of 2 years.] (Study III)
 | Placebo (N = 152) | Enbrel [Any dose.] (N = 349) | MTX (N = 217) | Enbrel (N = 415)
Adverse Reaction | Percent of Patients |  | Percent of Patients
Infection [Includes bacterial, viral and fungal infections.] (total) | 39 | 50 | 86 | 81
Upper Respiratory Infections [Most frequent Upper Respiratory Infections were upper respiratory tract infection, sinusitis and influenza.] | 30 | 38 | 70 | 65
Non-upper Respiratory Infections | 15 | 21 | 59 | 54
Injection Site Reactions | 11 | 37 | 18 | 43
Diarrhea | 9 | 8 | 16 | 16
Rash | 2 | 3 | 19 | 13
Pruritus | 1 | 2 | 5 | 5
Pyrexia | - | 3 | 4 | 2
Urticaria | 1 | - | 4 | 2
Hypersensitivity | - | - | 1 | 1

In placebo-controlled adult PsO trials, the percentages of patients reporting adverse reactions in the 50 mg twice a week dose group were similar to those observed in the 25 mg twice a week dose group or placebo group.

Table 4 summarizes adverse reactions reported in adult PsO patients from Studies I and II.

Table 4. Percent of Adult PsO Patients Experiencing Adverse Reactions in Placebo-Controlled Portions of Clinical Trials (Studies I & II)
 | Placebo (N = 359) | Enbrel [Includes 25 mg subcutaneous (SC) once weekly (QW), 25 mg SC twice weekly (BIW), 50 mg SC QW, and 50 mg SC BIW doses.] (N = 876)
Adverse Reaction | Percent of Patients
Infection [Includes bacterial, viral and fungal infections.] (total) | 28 | 27
Non-upper Respiratory Infections | 14 | 12
Upper Respiratory Infections [Most frequent Upper Respiratory Infections were upper respiratory tract infection, nasopharyngitis and sinusitis.] | 17 | 17
Injection Site Reactions | 6 | 15
Diarrhea | 2 | 3
Rash | 1 | 1
Pruritus | 2 | 1
Urticaria | - | 1
Hypersensitivity | - | 1
Pyrexia | 1 | -

6.2 Immunogenicity

As with all therapeutic proteins, there is potential for immunogenicity. The detection of antibody formation is highly dependent on the sensitivity and specificity of the assay. Additionally, the observed incidence of antibody (including neutralizing antibody) positivity in an assay may be influenced by several factors including assay methodology, sample handling, timing of sample collection, concomitant medications, and underlying disease. For these reasons, comparison of the incidence of antibodies to etanercept in the studies described below with the incidence of antibodies in other studies or to other products may be misleading.

Immunogenicity

Patients with RA, PsA, AS or PsO were tested at multiple time points for antibodies to etanercept. Antibodies to the TNF receptor portion or other protein components of the Enbrel drug product were detected at least once in sera of approximately 6% of adult patients with RA, PsA, AS or PsO. These antibodies were all non-neutralizing. Results from JIA patients were similar to those seen in adult RA patients treated with Enbrel.

In adult PsO studies that evaluated the exposure of etanercept for up to 120 weeks, the percentage of patients testing positive at the assessed time points of 24, 48, 72 and 96 weeks ranged from 3.6%-8.7% and were all non-neutralizing. The percentage of patients testing positive increased with an increase in the duration of study; however, the clinical significance of this finding is unknown. No apparent correlation of antibody development to clinical response or adverse events was observed. The immunogenicity data of Enbrel beyond 120 weeks of exposure are unknown.

In pediatric PsO studies, approximately 10% of subjects developed antibodies to etanercept by Week 48 and approximately 16% of subjects developed antibodies to etanercept by Week 264. All of these antibodies were non-neutralizing. However, because of the limitations of the immunogenicity assays, the incidence of binding and neutralizing antibodies may not have been reliably determined.

The data reflect the percentage of patients whose test results were considered positive for antibodies to etanercept in an ELISA assay, and are highly dependent on the sensitivity and specificity of the assay.

Autoantibodies

Patients with RA had serum samples tested for autoantibodies at multiple time points. In RA Studies I and II, the percentage of patients evaluated for antinuclear antibodies (ANA) who developed new positive ANA (titer ≥ 1:40) was higher in patients treated with Enbrel (11%) than in placebo-treated patients (5%). The percentage of patients who developed new positive anti-double-stranded DNA antibodies was also higher by radioimmunoassay (15% of patients treated with Enbrel compared to 4% of placebo-treated patients) and by Crithidia luciliae assay (3% of patients treated with Enbrel compared to none of placebo-treated patients). The proportion of patients treated with Enbrel who developed anticardiolipin antibodies was similarly increased compared to placebo-treated patients. In RA Study III, no pattern of increased autoantibody development was seen in Enbrel patients compared to MTX patients [see Warnings and Precautions (5.9)].

6.3 Postmarketing Experience

Adverse reactions have been reported during post approval use of Enbrel in adults and pediatric patients. Because these reactions are reported voluntarily from a population of uncertain size, it is not always possible to reliably estimate their frequency or establish a causal relationship to Enbrel exposure.

Adverse reactions are listed by body system below:

Blood and lymphatic system disorders: | pancytopenia, anemia, leukopenia, neutropenia, thrombocytopenia, lymphadenopathy, aplastic anemia [see Warnings and Precautions (5.5)]
Cardiac disorders: | congestive heart failure [see Warnings and Precautions (5.4)]
Gastrointestinal disorders: | inflammatory bowel disease (IBD)
General disorders: | angioedema, chest pain
Hepatobiliary disorders: | autoimmune hepatitis, elevated transaminases, hepatitis B reactivation
Immune disorders: | macrophage activation syndrome, systemic vasculitis, sarcoidosis
Musculoskeletal and connective tissue disorders: | lupus-like syndrome
Neoplasms benign, malignant, and unspecified: | melanoma and non-melanoma skin cancers, Merkel cell carcinoma [see Warnings and Precautions (5.3)]
Nervous system disorders: | convulsions, multiple sclerosis, demyelination, optic neuritis, transverse myelitis, paresthesias, headache [see Warnings and Precautions (5.2)]
Ocular disorders: | uveitis, scleritis
Renal and urinary disorders: | glomerulonephritis
Respiratory, thoracic and mediastinal disorders: | interstitial lung disease
Skin and subcutaneous tissue disorders: | cutaneous lupus erythematosus, cutaneous vasculitis (including leukocytoclastic vasculitis), erythema multiforme, Stevens-Johnson syndrome, toxic epidermal necrolysis, subcutaneous nodule, new or worsening psoriasis (all sub-types including pustular and palmoplantar)

Opportunistic infections, including atypical mycobacterial infection, herpes zoster, aspergillosis and Pneumocystis jiroveci pneumonia, and protozoal infections have also been reported in postmarketing use.

Rare (< 0.1%) cases of IBD have been reported in JIA patients receiving Enbrel, which is not effective for the treatment of IBD.

7 DRUG INTERACTIONS

Specific drug interaction studies have not been conducted with Enbrel.

7.1 Vaccines

Most PsA patients receiving Enbrel were able to mount effective B-cell immune responses to pneumococcal polysaccharide vaccine, but titers in aggregate were moderately lower and fewer patients had 2-fold rises in titers compared to patients not receiving Enbrel. The clinical significance of this is unknown. Patients receiving Enbrel may receive concurrent vaccinations, except for live vaccines. No data are available on the secondary transmission of infection by live vaccines in patients receiving Enbrel.

Patients with a significant exposure to varicella virus should temporarily discontinue Enbrel therapy and be considered for prophylactic treatment with varicella zoster immune globulin [see Warnings and Precautions (5.8, 5.10)].

7.2 Immune-Modulating Biologic Products

In a study in which patients with active RA were treated for up to 24 weeks with concurrent Enbrel and anakinra therapy, a 7% rate of serious infections was observed, which was higher than that observed with Enbrel alone (0%) [see Warnings and Precautions (5.12)] and did not result in higher ACR response rates compared to Enbrel alone. The most common infections consisted of bacterial pneumonia (4 cases) and cellulitis (4 cases). One patient with pulmonary fibrosis and pneumonia died due to respiratory failure. Two percent of patients treated concurrently with Enbrel and anakinra developed neutropenia (ANC < 1 × 10^9/L).

In clinical studies, concurrent administration of abatacept and Enbrel resulted in increased incidences of serious adverse events, including infections, and did not demonstrate increased clinical benefit [see Warnings and Precautions (5.12)].

7.3 Cyclophosphamide

The use of Enbrel in patients receiving concurrent cyclophosphamide therapy is not recommended [see Warnings and Precautions (5.11)].

7.4 Sulfasalazine

Patients in a clinical study who were on established therapy with sulfasalazine, to which Enbrel was added, were noted to develop a mild decrease in mean neutrophil counts in comparison to groups treated with either Enbrel or sulfasalazine alone. The clinical significance of this observation is unknown.

8 USE IN SPECIFIC POPULATIONS

8.1 Pregnancy

Risk Summary

Available studies with use of etanercept during pregnancy do not reliably support an association between etanercept and major birth defects. Clinical data are available from the Organization of Teratology Information Specialists (OTIS) Enbrel Pregnancy Registry in women with rheumatic diseases or psoriasis and a Scandinavian study in pregnant women with chronic inflammatory disease. Both the OTIS Registry and the Scandinavian study showed the proportion of liveborn infants with major birth defects was higher for women exposed to etanercept compared to diseased etanercept unexposed women. However, the lack of pattern of major birth defects is reassuring and differences between exposure groups (e.g., disease severity) may have impacted the occurrence of birth defects (see Data).

Reports of etanercept use during the third trimester of pregnancy demonstrated that placental transfer of etanercept was low in infants at birth (see Data). There are risks to the mother and fetus associated with active rheumatoid arthritis. The theoretical risks of administration of live or live-attenuated vaccines to the infants exposed in utero to Enbrel should be weighed against the benefits of vaccinations (see Clinical Considerations).

In animal reproduction studies with pregnant rats and rabbits, no fetal harm or malformations were observed with subcutaneous administration of etanercept during the period of organogenesis at doses that achieved systemic exposures 48 to 58 times the exposure in patients treated with 50 mg Enbrel once weekly (see Data).

All pregnancies have a background risk of birth defect, loss, or other adverse outcomes. The estimated background risk of major birth defects and miscarriage for the indicated populations is unknown. In the United States, about 2-4% of liveborn babies have a major birth defect and about 15-20% of pregnancies end in miscarriage, regardless of drug exposure.

Clinical Considerations

Disease-Associated Maternal and/or Embryo/Fetal Risk

Published data suggest that the risk of adverse pregnancy outcomes in women with rheumatoid arthritis is correlated with maternal disease activity and that active disease increases the risk of adverse pregnancy outcomes, including fetal loss, preterm delivery (before 37 weeks of gestation), low birth weight (less than 2500 g) and small for gestational age birth.

Fetal/Neonatal Adverse Reactions

The risk of fetal/neonatal adverse reactions with in utero exposure to Enbrel is unknown. Risks and benefits should be considered prior to administering live or live -attenuated vaccines to infants exposed to Enbrel in utero [see Warnings and Precautions (5.8) and Drug Interactions (7.1)].

Data

Human Data

A prospective cohort pregnancy registry conducted by OTIS in the US and Canada between 2000 and 2012 compared the risk of major birth defects in liveborn infants of women with rheumatic diseases or psoriasis exposed to etanercept in the first trimester. The proportion of major birth defects among liveborn infants in the etanercept-exposed (N = 319) and diseased etanercept unexposed cohorts (N = 144) was 9.4% and 3.5%, respectively. The findings showed no statistically significant increased risk of minor birth defects and no pattern of major or minor birth defects.

A Scandinavian study compared the risk of major birth defects in liveborn infants of women with chronic inflammatory disease (CID) exposed to TNF-inhibitors during early pregnancy. Women were identified from the Danish (2004-2012) and Swedish (2006-2012) population-based health registers. The proportion of major birth defects among liveborn infants in the etanercept-exposed (N = 344) and CID etanercept unexposed cohorts (N = 21,549) was 7.0% and 4.7%, respectively.

Overall, while both the OTIS Registry and Scandinavian study show a higher proportion of major birth defects in etanercept-exposed patients compared to diseased etanercept unexposed patients, the lack of pattern of birth defects is reassuring and differences between exposure groups (e.g., disease severity) may have impacted the occurrence of birth defects.

Reports from the literature showed that cord blood levels of etanercept at delivery, in infants born to women administered etanercept during pregnancy, varied from undetectable to 32% of the maternal serum level. In a cohort study of 30 pregnant women with RA, 29 were treated with etanercept until 30 weeks of gestation and 1 was treated until 36 weeks of gestation. Etanercept was not detected in the cord blood sample from any infant at delivery. In three published case reports, etanercept was detected in cord blood at levels of 3.3, 3.6, and 7.4% of the maternal concentration, when etanercept was administered at 50 mg every 7-12 days in pregnancy until 4 days prior to delivery, 25 mg twice weekly until 36 weeks of gestation, and 25 mg subcutaneous every week through the third trimester, respectively. There was one post-marketing safety report of a pregnant woman who received etanercept 25 mg once to twice weekly throughout pregnancy, and etanercept was detected in cord blood at 32% of the maternal concentration.

Animal Data

In embryofetal development studies with etanercept administered during the period of organogenesis to pregnant rats from gestation day (GD) 6 through 20 or pregnant rabbits from GD 6 through 18, there was no evidence of fetal malformations or embryotoxicity in rats or rabbits at respective doses that achieved systemic exposures 48 to 58 times the exposure in patients treated with 50 mg Enbrel once weekly (on an AUC basis with maternal subcutaneous doses up to 30 mg/kg/day in rats and 40 mg/kg/day in rabbits). In a peri-and post-natal development study with pregnant rats that received etanercept during organogenesis and the later gestational period from GD 6 through 21, development of pups through post-natal day 4 was unaffected at doses that achieved exposures 48 times the exposure in patients treated with 50 mg Enbrel once weekly (on an AUC basis with maternal subcutaneous doses up to 30 mg/kg/day).

8.2 Lactation

Risk Summary

Data from published literature show that etanercept is present in low levels in human milk but is not detected in the plasma of breastfed infants (see Data). There are no data on the effects of etanercept on milk production. There have been no consistent reports of adverse events in breastfed infants over decades of use. The developmental and health benefits of breastfeeding should be considered along with the mother's clinical need for Enbrel and any potential adverse effects on the breastfed child from the drug or from the underlying maternal condition.

Data

In three case reports, etanercept was detected in breast milk at levels ranging from <2 to 7.5 ng/mL after lactating women had received doses of etanercept of 25 mg weekly or twice weekly. Although etanercept was detected in breast milk in these cases, etanercept was not detected in the serum of the breastfed infants.

8.4 Pediatric Use

Polyarticular Juvenile Idiopathic Arthritis

The safety and effectiveness of Enbrel have been established in pediatric patients 2 years of age and older with pJIA. Enbrel has been studied in 69 children with moderately to severely active polyarticular JIA 2 to 17 years of age.

The safety and effectiveness of Enbrel in pediatric patients less than 2 years of age with pJIA have not been established.

Juvenile Psoriatic Arthritis

The safety and effectiveness of Enbrel have been established in pediatric patients 2 years to 17 years old with JPsA. Use of Enbrel in JPsA is supported by evidence from adequate and well controlled studies of Enbrel in adults with PsA; pharmacokinetic data from adult patients with PsA, RA, and PsO; and pharmacokinetic data from pediatric patients with active JIA and PsO. Safety of Enbrel in JPsA is supported by a clinical study in 69 pediatric patients with moderately to severely active JIA aged 2 to 17 years; a clinical study in 211 pediatric patients with moderate to severe PsO aged 4 to 17 years; and an open-label extension study in 182 pediatric patients with moderate to severe PsO aged 4 to 17 years.

The observed pre-dose (trough) concentrations are generally comparable between adults with RA and PsA and pediatric patients with active JIA, as well as adults with PsO and pediatric patients with PsO. The PK exposure is expected to be comparable between adults with PsA and pediatric patients with JPsA [see Adverse Reactions (6.1), Clinical Pharmacology (12.3), and Clinical Studies (14.1, 14.2, 14.3, 14.5, 14.6)].

The safety and effectiveness in pediatric patients below the age of 2 years have not been established in JPsA.

Plaque Psoriasis

The safety and effectiveness of Enbrel for plaque psoriasis have been established in pediatric patients 4 years of age and older. Enbrel has been studied in 211 pediatric patients with moderate to severe PsO aged 4 to 17 years.

The safety and effectiveness of Enbrel in pediatric patients below the age of 4 years with PsO have not been established.

Malignancies in Pediatric Patients

Malignancies, some fatal, have been reported among children, adolescents, and young adults who received treatment with TNF-blocking agents (initiation of therapy at ≤ 18 years of age), including Enbrel [see Warnings and Precautions (5.3)].

8.5 Geriatric Use

A total of 480 RA patients ages 65 years or older have been studied in clinical trials. In PsO randomized clinical trials, a total of 138 out of 1965 patients treated with Enbrel or placebo were age 65 or older. No overall differences in safety or effectiveness were observed between these patients and younger patients, but the number of geriatric PsO patients is too small to determine whether they respond differently from younger patients. Because there is a higher incidence of infections in the elderly population in general, caution should be used in treating the elderly.

8.6 Use in Patients with Diabetes

There have been reports of hypoglycemia following initiation of Enbrel therapy in patients receiving medication for diabetes, necessitating a reduction in anti-diabetic medication in some of these patients.

10 OVERDOSAGE

No dose-limiting toxicities have been observed during clinical trials of Enbrel. Single IV doses up to 60 mg/m^2 (approximately twice the recommended dose) have been administered to healthy volunteers in an endotoxemia study without evidence of dose-limiting toxicities.

11 DESCRIPTION

Etanercept, a tumor necrosis factor (TNF) blocker, is a dimeric fusion protein consisting of the extracellular ligand-binding portion of the human 75 kilodalton (p75) tumor necrosis factor receptor (TNFR) linked to the Fc portion of human IgG1. The Fc component of etanercept contains the CH2 domain, the CH3 domain and hinge region, but not the CH1 domain of IgG1. Etanercept is produced by recombinant DNA technology in a Chinese hamster ovary (CHO) mammalian cell expression system. It consists of 934 amino acids and has an apparent molecular weight of approximately 150 kilodaltons.

Enbrel (etanercept) Injection in the single-dose prefilled syringe, the single-dose prefilled SureClick autoinjector and the single-dose vial is clear and colorless, sterile, preservative-free solution, and is formulated at pH 6.3 ± 0.2.

Enbrel (etanercept) for Injection is supplied in a multiple-dose vial as a sterile, white, preservative-free, lyophilized powder. Reconstitution with 1 mL of the supplied Sterile Bacteriostatic Water for Injection, USP (containing 0.9% benzyl alcohol) yields a multiple-dose, clear, and colorless solution 1 mL containing 25 mg of Enbrel, with a pH of 7.4 ± 0.3.

Enbrel (etanercept) Injection in the Enbrel Mini single-dose prefilled cartridge for use with the AutoTouch reusable autoinjector is clear and colorless, sterile, preservative-free solution, and is formulated at pH 6.3 ± 0.2.

Table 5. Contents of Enbrel
Presentation | Active Ingredient Content | Inactive Ingredients Content
Enbrel 50 mg prefilled syringe and SureClick autoinjector | 50 mg etanercept in 1 mL | 25 mM L-arginine hydrochloride 120 mM sodium chloride 1% sucrose
Enbrel 25 mg prefilled syringe | 25 mg etanercept in 0.5 mL | 25 mM L-arginine hydrochloride 120 mM sodium chloride 1% sucrose
Enbrel 25 mg single-dose vial | 25 mg etanercept in 0.5 mL | 25 mM L-arginine hydrochloride 120 mM sodium chloride 1% sucrose
Enbrel 25 mg multiple-dose vial | After reconstitution, 25 mg etanercept in 1 mL | 40 mg mannitol 10 mg sucrose 1.2 mg tromethamine
Enbrel 50 mg Enbrel Mini single-dose prefilled cartridge for use with the AutoTouch reusable autoinjector only | 50 mg etanercept in 1 mL | 25 mM L-arginine hydrochloride 120 mM sodium chloride 1% sucrose

12 CLINICAL PHARMACOLOGY

12.1 Mechanism of Action

TNF is a naturally occurring cytokine that is involved in normal inflammatory and immune responses. It plays an important role in the inflammatory processes of RA, polyarticular JIA, PsA, and AS and the resulting joint pathology. In addition, TNF plays a role in the inflammatory process of PsO. Elevated levels of TNF are found in involved tissues and fluids of patients with RA, JIA, PsA, AS, and PsO.

Two distinct receptors for TNF (TNFRs), a 55 kilodalton protein (p55) and a 75 kilodalton protein (p75), exist naturally as monomeric molecules on cell surfaces and in soluble forms. Biological activity of TNF is dependent upon binding to either cell surface TNFR.

Etanercept is a dimeric soluble form of the p75 TNF receptor that can bind TNF molecules. Etanercept inhibits binding of TNF-α and TNF-β (lymphotoxin alpha [LT-α]) to cell surface TNFRs, rendering TNF biologically inactive. In in vitro studies, large complexes of etanercept with TNF-α were not detected and cells expressing transmembrane TNF (that binds Enbrel) are not lysed in the presence or absence of complement.

12.2 Pharmacodynamics

Etanercept can modulate biological responses that are induced or regulated by TNF, including expression of adhesion molecules responsible for leukocyte migration (e.g. E-selectin, and to a lesser extent, intercellular adhesion molecule-1 [ICAM-1]), serum levels of cytokines (e.g. IL-6), and serum levels of matrix metalloproteinase-3 (MMP-3 or stromelysin). Etanercept has been shown to affect several animal models of inflammation, including murine collagen-induced arthritis.

12.3 Pharmacokinetics

After administration of 25 mg of Enbrel by a single SC injection to 25 patients with RA, a mean ± standard deviation half-life of 102 ± 30 hours was observed with a clearance of 160 ± 80 mL/hr. A maximum serum concentration (Cmax) of 1.1 ± 0.6 mcg/mL and time to Cmax of 69 ± 34 hours was observed in these patients following a single 25 mg dose. After 6 months of twice weekly 25 mg doses in these same RA patients, the mean Cmax was 2.4 ± 1.0 mcg/mL (N = 23). Patients exhibited a 2- to 7-fold increase in peak serum concentrations and approximately 4-fold increase in AUC0-72 hr (range 1- to 17-fold) with repeated dosing. Serum concentrations in patients with RA have not been measured for periods of dosing that exceed 6 months.

In another study, serum concentration profiles at steady-state were comparable among patients with RA treated with 50 mg Enbrel once weekly and those treated with 25 mg Enbrel twice weekly. The mean (± standard deviation) Cmax, Cmin, and partial AUC were 2.4 ± 1.5 mcg/mL, 1.2 ± 0.7 mcg/mL, and 297 ± 166 mcg∙h/mL, respectively, for patients treated with 50 mg Enbrel once weekly (N = 21); and 2.6 ± 1.2 mcg/mL, 1.4 ± 0.7 mcg/mL, and 316 ± 135 mcg∙h/mL for patients treated with 25 mg Enbrel twice weekly (N = 16).

Patients with JIA (ages 4 to 17 years) were administered 0.4 mg/kg of Enbrel twice weekly (up to a maximum dose of 50 mg per week) for up to 18 weeks. The mean serum concentration after repeated SC dosing was 2.1 mcg/mL, with a range of 0.7 to 4.3 mcg/mL. Limited data suggest that the clearance of etanercept is reduced slightly in children ages 4 to 8 years. Population pharmacokinetic analyses predict that the pharmacokinetic differences between the regimens of 0.4 mg/kg twice weekly and 0.8 mg/kg once weekly in JIA patients are of the same magnitude as the differences observed between twice weekly and weekly regimens in adult RA patients.

The mean (± SD) serum steady-state trough concentrations for 50 mg QW dosing in adult PsA subjects were 2.1 ± 1.2 mcg/mL and 2.1 ± 1.4 mcg/mL at weeks 24 and 48, respectively.

The mean (± SD) serum steady-state trough concentrations for the 50 mg QW dosing in adult PsO subjects were 1.5 ± 0.7 mcg/mL. Pediatric PsO patients (age 4 to 17 years) were administered 0.8 mg/kg of Enbrel once weekly (up to a maximum dose of 50 mg per week) for up to 48 weeks. The mean (± SD) serum steady-state trough concentrations ranged from 1.6 ± 0.8 to 2.1 ± 1.3 mcg/mL at weeks 12, 24, and 48.

Overall, the observed etanercept concentrations in patients with JIA and pediatric PsO were within the range of those observed for adult RA, PsA and PsO after administration of Enbrel.

In clinical studies with Enbrel, pharmacokinetic parameters were not different between men and women and did not vary with age in adult patients. The pharmacokinetics of etanercept were unaltered by concomitant MTX in RA patients. No formal pharmacokinetic studies have been conducted to examine the effects of renal or hepatic impairment on etanercept disposition.

13 NONCLINICAL TOXICOLOGY

13.1 Carcinogenesis, Mutagenesis, Impairment of Fertility

Long-term animal studies have not been conducted to evaluate the carcinogenic potential of etanercept or its effect on fertility.

14 CLINICAL STUDIES

14.1 Adult Rheumatoid Arthritis

The safety and efficacy of Enbrel were assessed in four randomized, double-blind, controlled studies. The results of all four trials were expressed in percentage of patients with improvement in RA using ACR response criteria.

Study I evaluated 234 patients with active RA who were ≥ 18 years old, had failed therapy with at least one but no more than four disease-modifying antirheumatic drugs (DMARDs) (e.g. hydroxychloroquine, oral or injectable gold, MTX, azathioprine, D-penicillamine, sulfasalazine), and had ≥ 12 tender joints, ≥ 10 swollen joints, and either erythrocyte sedimentation rate (ESR) ≥ 28 mm/hr, C-reactive protein (CRP) > 2.0 mg/dL, or morning stiffness for ≥ 45 minutes. Doses of 10 mg or 25 mg Enbrel or placebo were administered SC twice a week for 6 consecutive months.

Study II evaluated 89 patients and had similar inclusion criteria to Study I except that patients in Study II had additionally received MTX for at least 6 months with a stable dose (12.5 to 25 mg/week) for at least 4 weeks and they had at least 6 tender or painful joints. Patients in Study II received a dose of 25 mg Enbrel or placebo SC twice a week for 6 months in addition to their stable MTX dose.

Study III compared the efficacy of Enbrel to MTX in patients with active RA. This study evaluated 632 patients who were ≥ 18 years old with early (≤ 3 years disease duration) active RA, had never received treatment with MTX, and had ≥ 12 tender joints, ≥ 10 swollen joints, and either ESR ≥ 28 mm/hr, CRP > 2.0 mg/dL, or morning stiffness for ≥ 45 minutes. Doses of 10 mg or 25 mg Enbrel were administered SC twice a week for 12 consecutive months. The study was unblinded after all patients had completed at least 12 months (and a median of 17.3 months) of therapy. The majority of patients remained in the study on the treatment to which they were randomized through 2 years, after which they entered an extension study and received open-label 25 mg Enbrel. MTX tablets (escalated from 7.5 mg/week to a maximum of 20 mg/week over the first 8 weeks of the trial) or placebo tablets were given once a week on the same day as the injection of placebo or Enbrel doses, respectively.

Study IV evaluated 682 adult patients with active RA of 6 months to 20 years duration (mean of 7 years) who had an inadequate response to at least one DMARD other than MTX. Forty-three percent of patients had previously received MTX for a mean of 2 years prior to the trial at a mean dose of 12.9 mg. Patients were excluded from this study if MTX had been discontinued for lack of efficacy or for safety considerations. The patient baseline characteristics were similar to those of patients in Study I. Patients were randomized to MTX alone (7.5 to 20 mg weekly, dose escalated as described for Study III; median dose 20 mg), Enbrel alone (25 mg twice weekly), or the combination of Enbrel and MTX initiated concurrently (at the same doses as above). The study evaluated ACR response, Sharp radiographic score, and safety.

Clinical Response

A higher percentage of patients treated with Enbrel and Enbrel in combination with MTX achieved ACR 20, ACR 50, and ACR 70 responses and Major Clinical Responses than in the comparison groups. The results of Studies I, II, and III are summarized in Table 6. The results of Study IV are summarized in Table 7.

Table 6. ACR Responses in Placebo- and Active-Controlled Trials (Percent of Patients)
 | Placebo-Controlled |  |  |  | Active-Controlled
 | Study I |  | Study II |  | Study III
 | Placebo | Enbrel [25 mg Enbrel SC twice weekly.] | MTX/Placebo | MTX/Enbrel | MTX | Enbrel
Response | N = 80 | N = 78 | N = 30 | N = 59 | N = 217 | N = 207
ACR 20
Month 3 | 23% | 62% [p < 0.01, Enbrel versus placebo.] | 33% | 66% | 56% | 62%
Month 6 | 11% | 59% | 27% | 71% | 58% | 65%
Month 12 | NA | NA | NA | NA | 65% | 72%
ACR 50
Month 3 | 8% | 41% | 0% | 42% | 24% | 29%
Month 6 | 5% | 40% | 3% | 39% | 32% | 40%
Month 12 | NA | NA | NA | NA | 43% | 49%
ACR 70
Month 3 | 4% | 15% | 0% | 15% | 7% | 13% [p < 0.05, Enbrel versus MTX.]
Month 6 | 1% | 15% | 0% | 15% | 14% | 21%
Month 12 | NA | NA | NA | NA | 22% | 25%

Table 7. Study IV Clinical Efficacy Results: Comparison of MTX versus Enbrel versus Enbrel in Combination with MTX in Patients with Rheumatoid Arthritis of 6 Months to 20 Years Duration (Percent of Patients)
Endpoint | MTX (N = 228) | Enbrel (N = 223) | Enbrel/MTX (N = 231)
ACR N [Values are medians.] , [ACR N is the percent improvement based on the same core variables used in defining ACR 20, ACR 50, and ACR 70.]
Month 12 | 40% | 47% | 63% [p < 0.05 for comparisons of Enbrel/MTX versus Enbrel alone or MTX alone.]
ACR 20
Month 12 | 59% | 66% | 75%
ACR 50
Month 12 | 36% | 43% | 63%
ACR 70
Month 12 | 17% | 22% | 40%
Major Clinical Response [Major clinical response is achieving an ACR 70 response for a continuous 6-month period.] | 6% | 10% | 24%

The time course for ACR 20 response rates for patients receiving placebo or 25 mg Enbrel in Studies I and II is summarized in Figure 1. The time course of responses to Enbrel in Study III was similar.

Figure 1. Time Course of ACR 20 Responses

Among patients receiving Enbrel, the clinical responses generally appeared within 1 to 2 weeks after initiation of therapy and nearly always occurred by 3 months. A dose response was seen in Studies I and III: 25 mg Enbrel was more effective than 10 mg (10 mg was not evaluated in Study II). Enbrel was significantly better than placebo in all components of the ACR criteria as well as other measures of RA disease activity not included in the ACR response criteria, such as morning stiffness.

In Study III, ACR response rates and improvement in all the individual ACR response criteria were maintained through 24 months of Enbrel therapy. Over the 2-year study, 23% of Enbrel patients achieved a major clinical response, defined as maintenance of an ACR 70 response over a 6-month period.

The results of the components of the ACR response criteria for Study I are shown in Table 8. Similar results were observed for Enbrel-treated patients in Studies II and III.

Table 8. Components of ACR Response in Study I
 | Placebo N = 80 |  | Enbrel [25 mg Enbrel SC twice weekly.] N = 78
Parameter (median) | Baseline | 3 Months | Baseline | 3 Months [Results at 6 months showed similar improvement.]
Number of tender joints [Scale 0-71.] | 34.0 | 29.5 | 31.2 | 10.0 [p < 0.01, Enbrel versus placebo, based on mean percent change from baseline.]
Number of swollen joints [Scale 0-68.] | 24.0 | 22.0 | 23.5 | 12.6
Physician global assessment [Visual analog scale: 0 = best; 10 = worst.] | 7.0 | 6.5 | 7.0 | 3.0
Patient global assessment | 7.0 | 7.0 | 7.0 | 3.0
Pain | 6.9 | 6.6 | 6.9 | 2.4
Disability index [Health Assessment Questionnaire: 0 = best; 3 = worst; includes eight categories: dressing and grooming, arising, eating, walking, hygiene, reach, grip, and activities.] | 1.7 | 1.8 | 1.6 | 1.0
ESR (mm/hr) | 31.0 | 32.0 | 28.0 | 15.5
CRP (mg/dL) | 2.8 | 3.9 | 3.5 | 0.9

After discontinuation of Enbrel, symptoms of arthritis generally returned within a month. Reintroduction of treatment with Enbrel after discontinuations of up to 18 months resulted in the same magnitudes of response as in patients who received Enbrel without interruption of therapy, based on results of open-label studies.

Continued durable responses were seen for over 60 months in open-label extension treatment trials when patients received Enbrel without interruption. A substantial number of patients who initially received concomitant MTX or corticosteroids were able to reduce their doses or discontinue these concomitant therapies while maintaining their clinical responses.

Physical Function Response

In Studies I, II, and III, physical function and disability were assessed using the Health Assessment Questionnaire (HAQ). Additionally, in Study III, patients were administered the SF-36 Health Survey. In Studies I and II, patients treated with 25 mg Enbrel twice weekly showed greater improvement from baseline in the HAQ score beginning in month 1 through month 6 in comparison to placebo (p < 0.001) for the HAQ disability domain (where 0 = none and 3 = severe). In Study I, the mean improvement in the HAQ score from baseline to month 6 was 0.6 (from 1.6 to 1.0) for the 25 mg Enbrel group and 0 (from 1.7 to 1.7) for the placebo group. In Study II, the mean improvement from baseline to month 6 was 0.6 (from 1.5 to 0.9) for the Enbrel/MTX group and 0.2 (from 1.3 to 1.2) for the placebo/MTX group. In Study III, the mean improvement in the HAQ score from baseline to month 6 was 0.7 (from 1.5 to 0.7) for 25 mg Enbrel twice weekly. All subdomains of the HAQ in Studies I and III were improved in patients treated with Enbrel.

In Study III, patients treated with 25 mg Enbrel twice weekly showed greater improvement from baseline in SF-36 physical component summary score compared to Enbrel 10 mg twice weekly and no worsening in the SF-36 mental component summary score. In open-label Enbrel studies, improvements in physical function and disability measures have been maintained for up to 4 years.

In Study IV, median HAQ scores improved from baseline levels of 1.8, 1.8, and 1.8 to 1.1, 1.0, and 0.6 at 12 months in the MTX, Enbrel, and Enbrel/MTX combination treatment groups, respectively (combination versus both MTX and Enbrel, p < 0.01). Twenty-nine percent of patients in the MTX alone treatment group had an improvement of HAQ of at least 1 unit versus 40% and 51% in the Enbrel alone and the Enbrel/MTX combination treatment groups, respectively.

Radiographic Response

In Study III, structural joint damage was assessed radiographically and expressed as change in Total Sharp Score (TSS) and its components, the erosion score and Joint Space Narrowing (JSN) score. Radiographs of hands/wrists and forefeet were obtained at baseline, 6 months, 12 months, and 24 months and scored by readers who were unaware of treatment group. The results are shown in Table 9. A significant difference for change in erosion score was observed at 6 months and maintained at 12 months.

Table 9. Mean Radiographic Change Over 6 and 12 Months in Study III
 |  | MTX | 25 mg Enbrel | MTX/Enbrel (95% Confidence Interval [95% confidence intervals for the differences in change scores between MTX and Enbrel.]) | P Value
12 Months | Total Sharp Score | 1.59 | 1.00 | 0.59 (-0.12, 1.30) | 0.1
 | Erosion Score | 1.03 | 0.47 | 0.56 (0.11, 1.00) | 0.002
 | JSN Score | 0.56 | 0.52 | 0.04 (-0.39, 0.46) | 0.5
6 Months | Total Sharp Score | 1.06 | 0.57 | 0.49 (0.06, 0.91) | 0.001
 | Erosion Score | 0.68 | 0.30 | 0.38 (0.09, 0.66) | 0.001
 | JSN Score | 0.38 | 0.27 | 0.11 (-0.14, 0.35) | 0.6

Patients continued on the therapy to which they were randomized for the second year of Study III. Seventy-two percent of patients had x-rays obtained at 24 months. Compared to the patients in the MTX group, greater inhibition of progression in TSS and erosion score was seen in the 25 mg Enbrel group, and, in addition, less progression was noted in the JSN score.

In the open-label extension of Study III, 48% of the original patients treated with 25 mg Enbrel have been evaluated radiographically at 5 years. Patients had continued inhibition of structural damage, as measured by the TSS, and 55% of them had no progression of structural damage. Patients originally treated with MTX had further reduction in radiographic progression once they began treatment with Enbrel.

In Study IV, less radiographic progression (TSS) was observed with Enbrel in combination with MTX compared with Enbrel alone or MTX alone at month 12 (Table 10). In the MTX treatment group, 55% of patients experienced no radiographic progression (TSS change ≤ 0.0) at 12 months compared to 63% and 76% in the Enbrel alone and the Enbrel/MTX combination treatment groups, respectively.

Table 10. Mean Radiographic Change in Study IV at 12 Months (95% Confidence Interval)
 | MTX (N = 212) [Analyzed radiographic ITT population.] | Enbrel (N = 212) | Enbrel/MTX (N = 218)
Total Sharp Score (TSS) | 2.80 (1.08, 4.51) | 0.52 [p < 0.05 for comparison of Enbrel versus MTX.] (-0.10, 1.15) | -0.54 [p < 0.05 for comparison of Enbrel/MTX versus MTX.] , [p < 0.05 for comparison of Enbrel/MTX versus Enbrel.] (-1.00, -0.07)
Erosion Score (ES) | 1.68 (0.61, 2.74) | 0.21 (-0.20, 0.61) | -0.30 (-0.65, 0.04)
Joint Space Narrowing (JSN) Score | 1.12 (0.34, 1.90) | 0.32 (0.00, 0.63) | -0.23, (-0.45, -0.02)

Once Weekly Dosing

The safety and efficacy of 50 mg Enbrel (two 25 mg SC injections) administered once weekly were evaluated in a double-blind, placebo-controlled study of 420 patients with active RA. Fifty-three patients received placebo, 214 patients received 50 mg Enbrel once weekly, and 153 patients received 25 mg Enbrel twice weekly. The safety and efficacy profiles of the two Enbrel treatment groups were similar.

14.2 Polyarticular Juvenile Idiopathic Arthritis (JIA)

The safety and efficacy of Enbrel were assessed in a 2-part study in 69 children with polyarticular JIA who had a variety of JIA onset types. Patients ages 2 to 17 years with moderately to severely active polyarticular JIA refractory to or intolerant of MTX were enrolled; patients remained on a stable dose of a single nonsteroidal anti-inflammatory drug and/or prednisone (≤ 0.2 mg/kg/day or 10 mg maximum). In part 1, all patients received 0.4 mg/kg (maximum 25 mg per dose) Enbrel SC twice weekly. In part 2, patients with a clinical response at day 90 were randomized to remain on Enbrel or receive placebo for 4 months and assessed for disease flare. Responses were measured using the JIA Definition of Improvement (DOI), defined as ≥ 30% improvement in at least three of six and ≥ 30% worsening in no more than one of the six JIA core set criteria, including active joint count, limitation of motion, physician and patient/parent global assessments, functional assessment, and ESR. Disease flare was defined as a ≥ 30% worsening in three of the six JIA core set criteria and ≥ 30% improvement in not more than one of the six JIA core set criteria and a minimum of two active joints.

In part 1 of the study, 51 of 69 (74%) patients demonstrated a clinical response and entered part 2. In part 2, 6 of 25 (24%) patients remaining on Enbrel experienced a disease flare compared to 20 of 26 (77%) patients receiving placebo (p = 0.007). From the start of part 2, the median time to flare was ≥ 116 days for patients who received Enbrel and 28 days for patients who received placebo. Each component of the JIA core set criteria worsened in the arm that received placebo and remained stable or improved in the arm that continued on Enbrel. The data suggested the possibility of a higher flare rate among those patients with a higher baseline ESR. Of patients who demonstrated a clinical response at 90 days and entered part 2 of the study, some of the patients remaining on Enbrel continued to improve from month 3 through month 7, while those who received placebo did not improve.

The majority of JIA patients who developed a disease flare in part 2 and reintroduced Enbrel treatment up to 4 months after discontinuation re-responded to Enbrel therapy in open-label studies. Most of the responding patients who continued Enbrel therapy without interruption have maintained responses for up to 48 months.

Studies have not been done in patients with polyarticular JIA to assess the effects of continued Enbrel therapy in patients who do not respond within 3 months of initiating Enbrel therapy, or to assess the combination of Enbrel with MTX.

14.3 Psoriatic Arthritis

The safety and efficacy of Enbrel were assessed in a randomized, double-blind, placebo-controlled study in 205 patients with PsA. Patients were between 18 and 70 years of age and had active PsA (≥ 3 swollen joints and ≥ 3 tender joints) in one or more of the following forms: (1) distal interphalangeal (DIP) involvement (N = 104); (2) polyarticular arthritis (absence of rheumatoid nodules and presence of psoriasis; N = 173); (3) arthritis mutilans (N = 3); (4) asymmetric psoriatic arthritis (N = 81); or (5) ankylosing spondylitis-like (N = 7). Patients also had plaque psoriasis with a qualifying target lesion ≥ 2 cm in diameter. Patients on MTX therapy at enrollment (stable for ≥ 2 months) could continue at a stable dose of ≤ 25 mg/week MTX. Doses of 25 mg Enbrel or placebo were administered SC twice a week during the initial 6-month double-blind period of the study. Patients continued to receive blinded therapy in an up to 6-month maintenance period until all patients had completed the controlled period. Following this, patients received open-label 25 mg Enbrel twice a week in a 12-month extension period.

Compared to placebo, treatment with Enbrel resulted in significant improvements in measures of disease activity (Table 11).

Table 11. Components of Disease Activity in Psoriatic Arthritis
 | Placebo N = 104 |  | Enbrel [p < 0.001 for all comparisons between Enbrel and placebo at 6 months.] N = 101
Parameter (median) | Baseline | 6 Months | Baseline | 6 Months
Number of tender joints [Scale 0-78.] | 17.0 | 13.0 | 18.0 | 5.0
Number of swollen joints [Scale 0-76.] | 12.5 | 9.5 | 13.0 | 5.0
Physician global assessment [Likert scale: 0 = best; 5 = worst.] | 3.0 | 3.0 | 3.0 | 1.0
Patient global assessment | 3.0 | 3.0 | 3.0 | 1.0
Morning stiffness (minutes) | 60 | 60 | 60 | 15
Pain | 3.0 | 3.0 | 3.0 | 1.0
Disability index [Health Assessment Questionnaire: 0 = best; 3 = worst; includes eight categories: dressing and grooming, arising, eating, walking, hygiene, reach, grip, and activities.] | 1.0 | 0.9 | 1.1 | 0.3
CRP (mg/dL) [Normal range: 0-0.79 mg/dL.] | 1.1 | 1.1 | 1.6 | 0.2

Among patients with PsA who received Enbrel, the clinical responses were apparent at the time of the first visit (4 weeks) and were maintained through 6 months of therapy. Responses were similar in patients who were or were not receiving concomitant MTX therapy at baseline. At 6 months, the ACR 20/50/70 responses were achieved by 50%, 37%, and 9%, respectively, of patients receiving Enbrel, compared to 13%, 4%, and 1%, respectively, of patients receiving placebo. Similar responses were seen in patients with each of the subtypes of PsA, although few patients were enrolled with the arthritis mutilans and ankylosing spondylitis-like subtypes. The results of this study were similar to those seen in an earlier single-center, randomized, placebo-controlled study of 60 patients with PsA.

The skin lesions of psoriasis were also improved with Enbrel, relative to placebo, as measured by percentages of patients achieving improvements in the Psoriasis Area and Severity Index (PASI). Responses increased over time, and at 6 months, the proportions of patients achieving a 50% or 75% improvement in the PASI were 47% and 23%, respectively, in the Enbrel group (N = 66), compared to 18% and 3%, respectively, in the placebo group (N = 62). Responses were similar in patients who were or were not receiving concomitant MTX therapy at baseline.

Radiographic Response

Radiographic changes were also assessed in the PsA study. Radiographs of hands and wrists were obtained at baseline and months 6, 12, and 24. A modified Total Sharp Score (TSS), which included distal interphalangeal joints (i.e., not identical to the modified TSS used for RA) was used by readers blinded to treatment group to assess the radiographs. Some radiographic features specific to PsA (e.g. pencil-and-cup deformity, joint space widening, gross osteolysis, and ankylosis) were included in the scoring system, but others (e.g. phalangeal tuft resorption, juxta-articular and shaft periostitis) were not.

Most patients showed little or no change in the modified TSS during this 24-month study (median change of 0 in both patients who initially received Enbrel or placebo). More placebo-treated patients experienced larger magnitudes of radiographic worsening (increased TSS) compared to Enbrel treatment during the controlled period of the study. At 12 months, in an exploratory analysis, 12% (12 of 104) of placebo patients compared to none of the 101 Enbrel-treated patients had increases of 3 points or more in TSS. Inhibition of radiographic progression was maintained in patients who continued on Enbrel during the second year. Of the patients with 1-year and 2-year x-rays, 3% (2 of 71) had increases of 3 points or more in TSS at 1 and 2 years.

Physical Function Response

In the PsA study, physical function and disability were assessed using the HAQ Disability Index (HAQ-DI) and the SF-36 Health Survey. Patients treated with 25 mg Enbrel twice weekly showed greater improvement from baseline in the HAQ-DI score (mean decreases of 54% at both months 3 and 6) in comparison to placebo (mean decreases of 6% at both months 3 and 6) (p < 0.001). At months 3 and 6, patients treated with Enbrel showed greater improvement from baseline in the SF-36 physical component summary score compared to patients treated with placebo, and no worsening in the SF-36 mental component summary score. Improvements in physical function and disability measures were maintained for up to 2 years through the open-label portion of the study.

14.4 Ankylosing Spondylitis

The safety and efficacy of Enbrel were assessed in a randomized, double-blind, placebo-controlled study in 277 patients with active AS. Patients were between 18 and 70 years of age and had AS as defined by the modified New York Criteria for Ankylosing Spondylitis. Patients were to have evidence of active disease based on values of ≥ 30 on a 0-100 unit Visual Analog Scale (VAS) for the average of morning stiffness duration and intensity, and two of the following three other parameters: a) patient global assessment, b) average of nocturnal and total back pain, and c) the average score on the Bath Ankylosing Spondylitis Functional Index (BASFI). Patients with complete ankylosis of the spine were excluded from study participation. Patients taking hydroxychloroquine, sulfasalazine, methotrexate, or prednisone (≤ 10 mg/day) could continue these drugs at stable doses for the duration of the study. Doses of 25 mg Enbrel or placebo were administered SC twice a week for 6 months.

The primary measure of efficacy was a 20% improvement in the Assessment in Ankylosing Spondylitis (ASAS) response criteria. Compared to placebo, treatment with Enbrel resulted in improvements in the ASAS and other measures of disease activity (Figure 2 and Table 12).

Figure 2. ASAS 20 Responses in Ankylosing Spondylitis

At 12 weeks, the ASAS 20/50/70 responses were achieved by 60%, 45%, and 29%, respectively, of patients receiving Enbrel, compared to 27%, 13%, and 7%, respectively, of patients receiving placebo (p ≤ 0.0001, Enbrel versus placebo). Similar responses were seen at Week 24. Responses were similar between those patients receiving concomitant therapies at baseline and those who were not. The results of this study were similar to those seen in a single-center, randomized, placebo-controlled study of 40 patients and a multicenter, randomized, placebo-controlled study of 84 patients with AS.

Table 12. Components of Ankylosing Spondylitis Disease Activity
 | Placebo N = 139 |  | Enbrel [p < 0.0015 for all comparisons between Enbrel and placebo at 6 months. P values for continuous endpoints were based on percent change from baseline.] N = 138
Median values at time points | Baseline | 6 Months | Baseline | 6 Months
ASAS response criteria
Patient global assessment [Measured on a Visual Analog Scale (VAS) with 0 = "none" and 100 = "severe".] | 63 | 56 | 63 | 36
Back pain [Average of total nocturnal and back pain scores, measured on a VAS with 0 = "no pain" and 100 = "most severe pain".] | 62 | 56 | 60 | 34
BASFI [Bath Ankylosing Spondylitis Functional Index (BASFI), average of 10 questions.] | 56 | 55 | 52 | 36
Inflammation [Inflammation represented by the average of the last 2 questions on the 6-question Bath Ankylosing Spondylitis Disease Activity Index (BASDAI).] | 64 | 57 | 61 | 33
Acute phase reactants
CRP (mg/dL) [C-reactive protein (CRP) normal range: 0-1.0 mg/dL.] | 2.0 | 1.9 | 1.9 | 0.6
Spinal mobility (cm):
Modified Schober's test | 3.0 | 2.9 | 3.1 | 3.3
Chest expansion | 3.2 | 3.0 | 3.3 | 3.9
Occiput-to-wall measurement | 5.3 | 6.0 | 5.6 | 4.5

14.5 Adult Plaque Psoriasis

The safety and efficacy of Enbrel were assessed in two randomized, double-blind, placebo-controlled studies in adults with chronic stable PsO involving ≥ 10% of the body surface area, a minimum Psoriasis Area and Severity Index (PASI) score of 10 and who had received or were candidates for systemic antipsoriatic therapy or phototherapy. Patients with guttate, erythrodermic, or pustular psoriasis and patients with severe infections within 4 weeks of screening were excluded from study. No concomitant major antipsoriatic therapies were allowed during the study.

Study I evaluated 672 subjects who received placebo or Enbrel SC at doses of 25 mg once a week, 25 mg twice a week, or 50 mg twice a week for 3 months. After 3 months, subjects continued on blinded treatments for an additional 3 months during which time subjects originally randomized to placebo began treatment with blinded Enbrel at 25 mg twice weekly (designated as placebo/Enbrel in Table 13); subjects originally randomized to Enbrel continued on the originally randomized dose (designated as Enbrel/Enbrel groups in Table 13).

Study II evaluated 611 subjects who received placebo or Enbrel SC at doses of 25 mg or 50 mg twice a week for 3 months. After 3 months of randomized, blinded treatment, subjects in all three arms began receiving open-label Enbrel at 25 mg twice weekly for 9 additional months.

Response to treatment in both studies was assessed after 3 months of therapy and was defined as the proportion of subjects who achieved a reduction in PASI score of at least 75% from baseline. The PASI is a composite score that takes into consideration both the fraction of body surface area affected and the nature and severity of psoriatic changes within the affected regions (induration, erythema and scaling).

Other evaluated outcomes included the proportion of subjects who achieved a score of "clear" or "minimal" by the Static Physician Global Assessment (sPGA) and the proportion of subjects with a reduction of PASI of at least 50% from baseline. The sPGA is a 6-category scale ranging from "5 = severe" to "0 = none" indicating the physician's overall assessment of the PsO severity focusing on induration, erythema and scaling. Treatment success of "clear" or "minimal" consisted of none or minimal elevation in plaque, up to faint red coloration in erythema and none or minimal fine scale over < 5% of the plaque.

Subjects in all treatment groups and in both studies had a median baseline PASI score ranging from 15 to 17, and the percentage of subjects with baseline sPGA classifications ranged from 54% to 66% for moderate, 17% to 26% for marked and 1% to 5% for severe. Across all treatment groups, the percentage of subjects who previously received systemic therapy for PsO ranged from 61% to 65% in Study I and 71% to 75% in Study II, and those who previously received phototherapy ranged from 44% to 50% in Study I and 72% to 73% in Study II.

More subjects randomized to Enbrel than placebo achieved at least a 75% reduction from baseline PASI score (PASI 75) with a dose response relationship across doses of 25 mg once a week, 25 mg twice a week and 50 mg twice a week (Tables 13 and 14). The individual components of the PASI (induration, erythema and scaling) contributed comparably to the overall treatment-associated improvement in PASI.

Table 13. Study I Outcomes at 3 and 6 Months
 | Placebo/Enbrel | Enbrel/Enbrel
 | 25 mg BIW | 25 mg QW | 25 mg BIW | 50 mg BIW
 | (N = 168) | (N = 169) | (N = 167) | (N = 168)
3 Months
PASI 75 n (%) | 6 (4%) | 23 (14%) [p = 0.001 compared with placebo.] | 53 (32%) [p < 0.0001 compared with placebo.] | 79 (47%)
Difference (95% CI) |  | 10% (4, 16) | 28% (21, 36) | 43% (35, 52)
sPGA, "clear" or "minimal" n (%) | 8 (5%) | 36 (21%) | 53 (32%) | 79 (47%)
Difference (95% CI) |  | 17% (10, 24) | 27% (19, 35) | 42% (34, 50)
PASI 50 n (%) | 24 (14%) | 62 (37%) | 90 (54%) | 119 (71%)
Difference (95% CI) |  | 22% (13, 31) | 40% (30, 49) | 57% (48, 65)
6 Months
PASI 75 n (%) | 55 (33%) | 36 (21%) | 68 (41%) | 90 (54%)

Table 14. Study II Outcomes at 3 Months
 | Placebo | Enbrel
 |  | 25 mg BIW | 50 mg BIW
 | (N = 204) | (N = 204) | (N = 203)
PASI 75 n (%) | 6 (3%) | 66 (32%) [p < 0.0001 compared with placebo.] | 94 (46%)
Difference (95% CI) |  | 29% (23, 36) | 43% (36, 51)
sPGA, "clear" or "minimal" n (%) | 7 (3%) | 75 (37%) | 109 (54%)
Difference (95% CI) |  | 34% (26, 41) | 50% (43, 58)
PASI 50 n (%) | 18 (9%) | 124 (61%) | 147 (72%)
Difference (95% CI) |  | 52% (44, 60) | 64% (56, 71)

Among PASI 75 achievers in both studies, the median time to PASI 50 and PASI 75 was approximately 1 month and approximately 2 months, respectively, after the start of therapy with either 25 or 50 mg twice a week.

In Study I, subjects who achieved PASI 75 at month 6 were entered into a study drug withdrawal and retreatment period. Following withdrawal of study drug, these subjects had a median duration of PASI 75 of between 1 and 2 months.

In Study I, among subjects who were PASI 75 responders at 3 months, retreatment with their original blinded Enbrel dose after discontinuation of up to 5 months resulted in a similar proportion of responders as in the initial double-blind portion of the study.

In Study II, most subjects initially randomized to 50 mg twice a week continued in the study after month 3 and had their Enbrel dose decreased to 25 mg twice a week. Of the 91 subjects who were PASI 75 responders at month 3, 70 (77%) maintained their PASI 75 response at month 6.

14.6 Pediatric Plaque Psoriasis

A 48-week, randomized, double-blind, placebo-controlled study enrolled 211 pediatric subjects 4 to 17 years of age, with moderate to severe plaque psoriasis (PsO) (as defined by a sPGA score ≥ 3 [moderate, marked, or severe], involving ≥ 10% of the body surface area, and a PASI score ≥ 12) who were candidates for phototherapy or systemic therapy, or were inadequately controlled on topical therapy. Subjects in all treatment groups had a median baseline PASI score of 16.4, and the percentage of subjects with baseline sPGA classifications was 65% for moderate, 31% for marked, and 3% for severe. Across all treatment groups, the percentage of subjects who previously received systemic or phototherapy for PsO was 57%.

Subjects received Enbrel 0.8 mg/kg (up to a maximum of 50 mg per dose) or placebo once weekly for the first 12 weeks. After 12 weeks, subjects entered a 24-week open-label treatment period, in which all subjects received Enbrel at the same dose. This was followed by a 12-week withdrawal-retreatment period.

Response to treatment was assessed after 12 weeks of therapy and was defined as the proportion of subjects who achieved a reduction in PASI score of at least 75% from baseline. The PASI is a composite score that takes into consideration both the fraction of body surface area affected and the nature and severity of psoriatic changes within the affected regions (induration, erythema and scaling).

Other evaluated outcomes included the proportion of subjects who achieved a score of "clear" or "almost clear" by the sPGA and the proportion of subjects with a reduction in PASI score of at least 90% from baseline. The sPGA is a 6-category scale ranging from "5 = severe" to "0 = none" indicating the physician's overall assessment of the PsO severity focusing on induration, erythema and scaling. Treatment success of "clear" or "almost clear" consisted of none or minimal elevation in plaque, up to faint red coloration in erythema and none or minimal fine scale over < 5% of the plaque.

Efficacy results are summarized in Table 15.

Table 15. Pediatric Plaque Psoriasis Outcomes at 12 Weeks
 | Placebo (N = 105) | Enbrel 0.8 mg/kg Once Weekly (N = 106)
PASI 75, n (%) | 12 (11%) | 60 (57%)
PASI 90, n (%) | 7 (7%) | 29 (27%)
sPGA "clear" or "almost clear" n (%) | 14 (13%) | 55 (52%)

Maintenance of Response

To evaluate maintenance of response, subjects who achieved PASI 75 response at Week 36 were re-randomized to either Enbrel or placebo during a 12-week randomized withdrawal period. The maintenance of PASI 75 response was evaluated at Week 48. The proportion of subjects who maintained PASI 75 response at Week 48 was higher for subjects treated with Enbrel (65%) compared to those treated with placebo (49%).

15 REFERENCES

1. National Cancer Institute. Surveillance, Epidemiology, and End Results Database (SEER) Program. SEER Incidence Crude Rates, 13 Registries, 1992-2002.
2. Bröms G, Granath F, Ekbom A, et al. Low Risk of Birth Defects for Infants Whose Mothers Are Treated With Anti-Tumor Necrosis Factor Agents During Pregnancy. Clin Gastroenterol Hepatol. 2016;14:234-241.e5

16 HOW SUPPLIED/STORAGE AND HANDLING

Enbrel (etanercept) injection is supplied as a clear and colorless sterile, preservative-free solution for subcutaneous administration in single-dose prefilled syringes, an Enbrel single-dose prefilled SureClick autoinjector with a 27-gauge, ½-inch needle, or a single-dose vial. The prefilled syringe and SureClick autoinjector are not made with natural rubber latex.

Each Enbrel® Mini single-dose prefilled cartridge for use with the AutoTouch® reusable autoinjector contains 1.0 mL of 50 mg/mL of etanercept. The AutoTouch reusable autoinjector and Enbrel Mini single-dose prefilled cartridge are not made with natural rubber latex.

The AutoTouch reusable autoinjector contains no drug and must use an Enbrel Mini single-dose prefilled cartridge. In addition, the AutoTouch Connect® reusable autoinjector would allow for data connectivity via Bluetooth wireless technology.

50 mg/mL single-dose prefilled syringe | Carton of 4 | NDC 58406-021-04
50 mg/mL single-dose prefilled SureClick autoinjector | Carton of 4 | NDC 58406-032-04
25 mg/0.5 mL single-dose prefilled syringe | Carton of 4 | NDC 58406-010-04
50 mg/mL Enbrel Mini single-dose prefilled cartridge for use with the AutoTouch reusable autoinjector only | Cartridges: Carton of 4 | NDC 58406-044-04 NDC 58406-044-24
50 mg/mL Enbrel Mini single-dose prefilled cartridge for use with the AutoTouch reusable autoinjector only | AutoTouch Connect Reusable Autoinjector: Carton of 1 | NDC 58406-480-01
25 mg/0.5 mL single-dose vial | Carton of 4 | NDC 58406-055-04

STORAGE AND HANDLING

Enbrel should be refrigerated at 36°F to 46°F (2°C to 8°C) in the original carton to protect from light or physical damage. Do not store Enbrel in extreme heat or cold. DO NOT SHAKE. DO NOT FREEZE.

For convenience, storage of individual single-dose prefilled syringes, SureClick autoinjectors, single-dose vials, or Enbrel Mini cartridges at room temperature at 68°F to 77°F (20°C to 25°C) for a maximum single period of 30 days is permissible, with protection from light and sources of heat. Once a single-dose prefilled syringe, SureClick autoinjector, single-dose vial, or Enbrel Mini cartridge has been stored at room temperature, it should not be placed back into the refrigerator. If not used within 30 days at room temperature, the single-dose prefilled syringe, SureClick autoinjector, single-dose vial, or Enbrel Mini cartridge should be discarded.

Do not use Enbrel beyond the expiration date stamped on the carton or barrel/cartridge label. Keep out of the reach of children.

The AutoTouch reusable autoinjector should be stored at room temperature. Do not refrigerate the AutoTouch reusable autoinjector.

Enbrel Lyophilized Powder (Used for Weight-based Dosing)

Enbrel (etanercept) for Injection is supplied as lyophilized powder for reconstitution in a multiple-dose vial. Each vial is supplied in a carton containing four dose trays. Each dose tray contains one 25 mg vial of etanercept lyophilized powder, one diluent syringe (1 mL Sterile Bacteriostatic Water for Injection, USP, containing 0.9% benzyl alcohol), one 27-gauge ½-inch needle, one vial adapter, and one plunger. Each carton contains four "Mixing Date:" stickers.

25 mg multiple-dose vial | Carton of 4 | NDC 58406-425-34

Enbrel should be refrigerated at 36°F to 46°F (2°C to 8°C) in the original carton to protect from light or physical damage. Do not store Enbrel in extreme heat or cold. DO NOT SHAKE. DO NOT FREEZE.

For convenience, storage of an individual dose tray containing Enbrel multiple-dose vial and diluent syringe at room temperature at 68°F to 77°F (20°C to 25°C) for a maximum single period of 14 days is permissible, with protection from light, sources of heat, and humidity. Once the dose tray has been stored at room temperature, it should not be placed back into the refrigerator. If not used within 14 days at room temperature, the dose tray should be discarded. Once a vial has been reconstituted, the solution must be used immediately or may be refrigerated for up to 14 days.

Do not use Enbrel beyond the expiration date stamped on the dose tray. Keep out of the reach of children.

17 PATIENT COUNSELING INFORMATION

Advise the patient and/or caregiver to read the FDA-approved patient labeling (Medication Guide and Instructions for Use) before the patient starts using Enbrel, and each time the prescription is renewed, as there may be new information they need to know.

Patients or their caregivers should be provided the Enbrel "Medication Guide" and provided an opportunity to read it and ask questions prior to initiation of therapy. The healthcare provider should ask the patient questions to determine any risk factors for treatment. Patients developing signs and symptoms of infection should seek medical evaluation immediately.

Patient Counseling

Patients should be advised of the potential benefits and risks of Enbrel. Physicians should instruct their patients to read the Medication Guide before starting Enbrel therapy and to reread each time the prescription is renewed.

Infections

Inform patients that Enbrel may lower the ability of their immune system to fight infections. Advise patients of the importance of contacting their doctor if they develop any symptoms of infection, tuberculosis or reactivation of hepatitis B virus infections.

Other Medical Conditions

Advise patients to report any signs of new or worsening medical conditions, such as central nervous system demyelinating disorders, heart failure or autoimmune disorders, such as lupus-like syndrome or autoimmune hepatitis. Counsel about the risk of lymphoma and other malignancies while receiving Enbrel. Advise patients to report any symptoms suggestive of a pancytopenia, such as bruising, bleeding, persistent fever or pallor.

Allergic Reactions

Advise patients to seek immediate medical attention if they experience any symptoms of severe allergic reactions.

Administration of Enbrel

If a patient or caregiver is to administer Enbrel, the patient or caregiver should be instructed in injection techniques and how to measure and administer the correct dose [see "Instructions for Use"]. For weight-based dosing, instruct caregivers and patients on the proper techniques for preparing, storing, measuring, and administering Enbrel solution in a single-dose vial or reconstituted lyophilized powder in a multiple-dose vial.

The first injection should be performed under the supervision of a qualified healthcare professional. The patient's or caregiver's ability to inject subcutaneously should be assessed. Patients and caregivers should be instructed in the technique, as well as proper syringe and needle disposal, and be cautioned against reuse of needles and syringes.

When using the SureClick autoinjector to administer Enbrel, the patient or caregiver should be informed that the window turns yellow when the injection is complete. After removing the autoinjector, if the window has not turned yellow, or if it looks like the medicine is still injecting, this means the patient has not received a full dose. The patient or caregiver should be advised to call their healthcare provider immediately.

When using the AutoTouch reusable autoinjector to administer Enbrel, the patient or caregiver should be informed that the status button turns green upon contact with the skin, flashes green after starting the injection, and turns off at completion of the injection. After removing the AutoTouch reusable autoinjector from the skin, if the status button has turned red, the patient or caregiver should be advised to call 1-888-4Enbrel (1-888-436-2735) immediately. If it looks like the medicine is still injecting or there is still fluid in Enbrel Mini, this means the patient has not received a full dose. The patient or caregiver should be advised to call their healthcare provider immediately.

A puncture-resistant container for disposal of needles, syringes, SureClick autoinjectors, single-dose vials, and Enbrel Mini cartridges should be used. If the product is intended for multiple use, additional syringes, needles and alcohol swabs will be required.

Patients can be advised to call 1-888-4ENBREL (1-888-436-2735) or visit www.enbrel.com for more information about Enbrel.

AMGEN

Enbrel® (etanercept)

Manufactured by:
Immunex Corporation
Thousand Oaks, CA 91320-1799
U.S. License Number 1132

Patent: http://pat.amgen.com/enbrel/

© 1998-2024 Immunex Corporation. All rights reserved.
1XXXXXX – v74

This printed material is recyclable.

Medication Guide

Enbrel® (en-brel)
(etanercept)
injection, for subcutaneous use

Enbrel® (en-brel)
(etanercept)
for injection, for subcutaneous use

Read the Medication Guide that comes with Enbrel before you start using it and each time you get a refill. There may be new information. This Medication Guide does not take the place of talking with your healthcare provider about your medical condition or treatment. It is important to remain under your healthcare provider's care while using Enbrel.
Enbrel is a prescription medicine called a Tumor Necrosis Factor (TNF) blocker that affects your immune system.

What is the most important information I should know about Enbrel?
Enbrel may cause serious side effects, including:
1. Risk of Infection
2. Risk of Cancer
1. Risk of infection
Enbrel can lower the ability of your immune system to fight infections. Some people have serious infections while taking Enbrel. These infections include tuberculosis (TB), and infections caused by viruses, fungi, or bacteria that spread throughout their body. Some people have died from these infections.

- Your healthcare provider should test you for TB before starting Enbrel.
- Your healthcare provider should monitor you closely for symptoms of TB during treatment with Enbrel even if you tested negative for TB.
- Your healthcare provider should check you for symptoms of any type of infection before, during, and after your treatment with Enbrel.

You should not start taking Enbrel if you have any kind of infection unless your healthcare provider says it is okay.
2. Risk of cancer

- There have been cases of unusual cancers, some resulting in death, in children and teenagers who started using TNF-blocking agents at less than 18 years of age.
- For children, teenagers, and adults taking TNF-blocker medicines, including Enbrel, the chances of getting lymphoma or other cancers may increase.
- People with rheumatoid arthritis, especially those with very active disease, may be more likely to get lymphoma.

Before starting Enbrel, be sure to talk to your healthcare provider:

Enbrel may not be right for you. Before starting Enbrel, tell your healthcare provider about all of your medical conditions, including:
Infections. Tell your healthcare provider if you:

- have an infection. See "What is the most important information I should know about Enbrel?"
- are being treated for an infection.
- think you have an infection.
- have symptoms of an infection such as fever, sweats or chills, cough or flu-like symptoms, shortness of breath, blood in your phlegm, weight loss, muscle aches, warm, red or painful areas on your skin, sores on your body, diarrhea or stomach pain, burning when you urinate or urinating more often than normal, and feel very tired.
- have any open cuts on your body.
- get a lot of infections or have infections that keep coming back.
- have diabetes, HIV, or a weak immune system. People with these conditions have a higher chance for infections.
- have TB, or have been in close contact with someone with TB.
- were born in, lived in, or traveled to countries where there is a risk for getting TB. Ask your healthcare provider if you are not sure.
- live, have lived in, or traveled to certain parts of the country (such as the Ohio and Mississippi River valleys, or the Southwest) where there is a greater risk for getting certain kinds of fungal infections (histoplasmosis, coccidioidomycosis, blastomycosis). These infections may happen or become more severe if you use Enbrel. Ask your healthcare provider if you do not know if you live or have lived in an area where these infections are common.
- have or have had hepatitis B.

Also, before starting Enbrel, tell your healthcare provider:

- About all the medicines you take including prescription and over-the-counter medicines, vitamins and herbal supplements including:
  - Orencia (abatacept) or Kineret (anakinra). You have a higher chance for serious infections when taking Enbrel with Orencia or Kineret.
  - Cyclophosphamide (Cytoxan). You may have a higher chance for getting certain cancers when taking Enbrel with cyclophosphamide.
  - Anti-diabetic medicines. If you have diabetes and are taking medicine to control your diabetes, your healthcare provider may decide you need less anti-diabetic medicine while taking Enbrel.

Keep a list of all your medicines with you to show your healthcare provider and pharmacist each time you get a new medicine. Ask your healthcare provider if you are not sure if your medicine is one listed above.
Other important medical information you should tell your healthcare provider before starting Enbrel, includes if you:

- have or had a nervous system problem such as multiple sclerosis or Guillain-Barré syndrome.
- have or had heart failure.
- are scheduled to have surgery.
- have recently received or are scheduled to receive a vaccine.
  - All vaccines should be brought up-to-date before starting Enbrel.
  - People taking Enbrel should not receive live vaccines.
  - Ask your healthcare provider if you are not sure if you received a live vaccine.
- have been around someone with varicella zoster (chicken pox).
- are pregnant or plan to become pregnant. It is not known if Enbrel will harm your unborn baby. If you took Enbrel during pregnancy, talk to your healthcare provider prior to administration of live vaccines to your infant.
  are breastfeeding or plan to breastfeed. Enbrel can pass into breast milk. Talk to your healthcare provider about the best way to feed your baby while taking Enbrel.

See the section "What are the possible side effects of Enbrel?" below for more information.

What is Enbrel?
Enbrel is a prescription medicine called a Tumor Necrosis Factor (TNF) blocker.
Enbrel is used to treat:

- moderately to severely active rheumatoid arthritis (RA). Enbrel can be used alone or with a medicine called methotrexate.
- moderately to severely active polyarticular juvenile idiopathic arthritis (pJIA) in children 2 years of age or older.
- psoriatic arthritis (PsA) in adults. Enbrel can be used alone or with methotrexate.
- active juvenile psoriatic arthritis (JPsA) in children 2 years of age or older.
- ankylosing spondylitis (AS).
- chronic moderate to severe plaque psoriasis (PsO) in children 4 years of age or older and adults who may benefit from taking injections or pills (systemic therapy) or phototherapy (ultraviolet light).

You may continue to use other medicines that help treat your condition while taking Enbrel, such as nonsteroidal anti-inflammatory drugs (NSAIDs) and prescription steroids, as recommended by your healthcare provider.
Enbrel can help reduce joint damage and the signs and symptoms of the above-mentioned diseases. People with these diseases have too much of a protein called tumor necrosis factor (TNF), which is made by your immune system.
Enbrel can reduce the effect of TNF in the body and block the damage that too much TNF can cause, but it can also lower the ability of your immune system to fight infections. See "What is the most important information I should know about Enbrel?" and "What are the possible side effects of Enbrel?"

Who should not use Enbrel?
Do not use Enbrel if you:

- have an infection that has spread through your body (sepsis).

How should I use Enbrel?

- Enbrel is given as an injection under the skin (subcutaneous or SC).
- If your healthcare provider decides that you or a caregiver can give the injections of Enbrel at home, you or your caregiver should receive training on the right way to prepare and inject Enbrel. Do not try to inject Enbrel until you have been shown the right way by your healthcare provider or nurse.
- Enbrel is available in the forms listed below. Your healthcare provider will prescribe the type that is best for you.
  - Single-dose Prefilled Syringe
  - Single-dose Prefilled SureClick Autoinjector
  - Single-dose Vial
  - Multiple-dose Vial
  - Enbrel Mini single-dose cartridge for use with the AutoTouch reusable autoinjector
- See the detailed Instructions for Use with this Medication Guide for instructions about the right way to store, prepare, and give your Enbrel injections at home.
- Your healthcare provider will tell you how often you should use Enbrel. Do not miss any doses of Enbrel. If you forget to use Enbrel, inject your dose as soon as you remember. Then, take your next dose at your regular(ly) scheduled time. In case you are not sure when to inject Enbrel, call your healthcare provider or pharmacist. Do not use Enbrel more often than as directed by your healthcare provider.
- Your child's dose of Enbrel depends on his or her weight. Your child's healthcare provider will tell you which form of Enbrel to use and how much to give your child.

What are the possible side effects of Enbrel?
Enbrel can cause serious side effects, including:

- See "What is the most important information I should know about Enbrel?"
- Infections. Enbrel can make you more likely to get infections or make any infection that you have worse. Call your healthcare provider right away if you have any symptoms of an infection. See "Before starting Enbrel, be sure to talk to your healthcare provider" for a list of symptoms of infection.
- Previous Hepatitis B infection. If you have been previously infected with the hepatitis B virus (a virus that affects the liver), the virus can become active while you use Enbrel. Your healthcare provider may do a blood test before you start treatment with Enbrel and while you use Enbrel.
- Nervous system problems. Rarely, people who use TNF-blocker medicines have developed nervous system problems such as multiple sclerosis, seizures, or inflammation of the nerves of the eyes. Tell your healthcare provider right away if you get any of these symptoms: numbness or tingling in any part of your body, vision changes, weakness in your arms and legs, and dizziness.
- Blood problems. Low blood counts have been seen with other TNF-blocker medicines. Your body may not make enough of the blood cells that help fight infections or help stop bleeding. Symptoms include fever, bruising or bleeding very easily, or looking pale.
- New heart failure or worsening of heart failure you already have. New or worse heart failure can happen in people who use TNF-blocker medicines like Enbrel. If you have heart failure your condition should be watched closely while you take Enbrel. Call your healthcare provider right away if you get new or worsening symptoms of heart failure while taking Enbrel, such as shortness of breath or swelling of your lower legs or feet.
- Psoriasis. Some people using Enbrel developed new psoriasis or worsening of psoriasis they already had. Tell your healthcare provider if you develop red scaly patches or raised bumps that may be filled with pus. Your healthcare provider may decide to stop your treatment with Enbrel.
- Allergic reactions. Allergic reactions can happen to people who use TNF-blocker medicines. Call your healthcare provider right away if you have any symptoms of an allergic reaction. Symptoms of an allergic reaction include a severe rash, a swollen face, or trouble breathing.
- Autoimmune reactions, including:
  - Lupus-like syndrome. Symptoms include a rash on your face and arms that gets worse in the sun. Tell your healthcare provider if you have this symptom. Symptoms may go away when you stop using Enbrel.
  - Autoimmune hepatitis. Liver problems can happen in people who use TNF-blocker medicines, including Enbrel. These problems can lead to liver failure and death. Call your healthcare provider right away if you have any of these symptoms: feel very tired, skin or eyes look yellow, poor appetite or vomiting, pain on the right side of your stomach (abdomen).

Common side effects of Enbrel include:

- Injection site reactions such as redness, itching, pain, swelling, bleeding or bruising. These symptoms usually go away within 3 to 5 days. If you have pain, redness, or swelling around the injection site that does not go away or gets worse, call your healthcare provider.
- Upper respiratory infections (sinus infections).

These are not all the possible side effects with Enbrel. Tell your healthcare provider about any side effect that bothers you or does not go away.
Call your doctor for medical advice about side effects. You may report side effects to FDA at 1-800-FDA-1088.

How should I store Enbrel?

- Store Enbrel in the refrigerator between 36°F to 46°F (2°C to 8°C).
- Store Enbrel in the original carton to protect from light or damage.
- If needed, you may store your dose tray for the multiple-dose vial at room temperature between 68°F to 77°F (20°C to 25°C) for up to 14 days.
  - When the dose tray has reached room temperature, do not put it back in the refrigerator.
  - Throw away the dose tray that has been stored at room temperature after 14 days.
- Mixed Enbrel multiple-dose vials should be used right away or kept in the refrigerator between 36°F to 46°F (2°C to 8°C) for up to 14 days.
- If needed, you may store the Enbrel prefilled syringe, SureClick autoinjector, single-dose vial, or Enbrel Mini cartridge at room temperature between 68°F to 77°F (20°C to 25°C) for up to 30 days.
  - When Enbrel has reached room temperature, do not put it back in the refrigerator.
  - Throw away Enbrel that has been stored at room temperature after 30 days.
- Do not store Enbrel in extreme heat or cold such as in your vehicle's glove box or trunk.
- Do not shake.
- Do not freeze.
- Keep Enbrel and all medicines out of the reach of children.

General information about the safe and effective use of Enbrel.
Medicines are sometimes prescribed for purposes other than those listed in a Medication Guide. Do not use Enbrel for a condition for which it was not prescribed. Do not give Enbrel to other people, even if they have the same symptoms that you have. It may harm them.
This Medication Guide summarizes the most important information about Enbrel. If you would like more information, talk with your healthcare provider. You can ask your healthcare provider or pharmacist for information about Enbrel that is written for health professionals.

What are the ingredients in Enbrel?
Single-dose Prefilled Syringe, Single-dose Prefilled SureClick Autoinjector, Single-dose Vial and Enbrel Mini single-dose cartridge:
Active Ingredient: etanercept
Inactive Ingredients: L-arginine hydrochloride, sodium chloride, and sucrose
Multiple-dose Vial:
Active Ingredient: etanercept
Inactive Ingredients: mannitol, sucrose, tromethamine
AMGEN
Manufactured by: Immunex Corporation, Thousand Oaks, CA 91320-1799, U.S. License Number 1132
Immunex Corporation. All rights reserved. 1XXXXXX – v25
For more information, call 1 888 4ENBREL (1 888 436 2735) or www.enbrel.com.

This printed material is recyclable

This Medication Guide has been approved by the U.S. Food and Drug Administration.

Revised: 09/2024

INSTRUCTIONS FOR USE ENBREL® [en-brel] (etanercept) injection, for subcutaneous use 50 mg/mL single-dose prefilled SureClick® autoinjector

This Instructions for Use contains information on how to inject ENBREL with a SureClick autoinjector.

If your healthcare provider decides that you or a caregiver may be able to give your injections of ENBREL at home, you should receive training on the right way to prepare and inject ENBREL. Do not try to inject yourself until you have been shown the right way to give the injections by your healthcare provider or nurse.

The medicine in the ENBREL autoinjector is for injection under the skin (subcutaneous injection). See the ENBREL Medication Guide for information about ENBREL.

Getting to know the prefilled autoinjector

Important Information You Need to Know Before Injecting ENBREL

- It is important that you do not try to give the injection until you have fully read and understood this Instructions for Use.
- Check the autoinjector label and prescription to make sure you have the correct medicine and dose.
- Do not use the autoinjector if the carton is damaged or the seal is broken.
- Do not use the autoinjector after the expiration date on the label.
- Do not shake the autoinjector.
- Do not remove the white cap from the autoinjector until you are ready to inject.
- Do not use the autoinjector if it has been frozen.
- Do not use the autoinjector if it has been dropped on a hard surface. Part of the autoinjector may be broken even if you cannot see the break. Use a new autoinjector, and call 1-888-4ENBREL (1-888-436-2735).
- Children must weigh at least 138 pounds to use the ENBREL SureClick autoinjector. Children who weigh less than 138 pounds should use a different form of ENBREL.
- The autoinjector is not made with natural rubber latex.

Frequently asked questions:
For additional information and answers to frequently asked questions, visit www.enbrel.com.

Where to get help:
If you want more information or help using ENBREL:

- Contact your healthcare provider,
- Visit www.enbrel.com, or
- Call 1-888-4ENBREL (1-888-436-2735).

Storing and Preparing to Inject ENBREL

1 Refrigerate the autoinjector carton until you are ready to use it.
  - Keep the autoinjector in the refrigerator between 36°F to 46°F (2°C to 8°C).
  - Keep the autoinjector in the original carton to protect it from light or physical damage.
  - Do not freeze the autoinjector.
  - Do not store the autoinjector in extreme heat or cold. For example, avoid storing in your vehicle's glove box or trunk.

Important: Keep the autoinjector and all medicines out of the sight and reach of children.

WAIT

2 Wait 30 minutes for the autoinjector to reach room temperature.
  - Remove the autoinjector and put any unused autoinjectors back into the refrigerator.
  - Let the autoinjector warm up naturally.
  - Do not heat the autoinjector with hot water, a microwave, or direct sunlight.
  - Do not shake the autoinjector at any time.
  - Using the autoinjector at room temperature makes sure the full dose is delivered and allows for a more comfortable injection.

3 You may keep ENBREL at room temperature for up to 30 days, if needed.
  - For example, when you are traveling, you may keep ENBREL at room temperature.
  - Keep it at room temperature between 68°F to 77°F (20°C to 25°C).
  - Do not put it back in the refrigerator.
  - Record the date you removed it from the refrigerator and use it within 30 days.

Important: Place the autoinjector in a sharps disposal container if it has reached room temperature and has not been used within 30 days.

4 Inspect the medicine. It should be clear and colorless to slightly yellow.
  - It is okay to see air bubbles or small white particles in the medicine.
  - Do not use the autoinjector if the medicine is cloudy, discolored, or contains large lumps, flakes or colored particles.

Important: If the medicine is cloudy, discolored, or contains large lumps, flakes or colored particles, or if the autoinjector is damaged or expired, call 1-888-4ENBREL (1-888-436-2735).

5 Check the expiration date (Exp.) and inspect the autoinjector for damage.
  - Do not use the autoinjector if the expiration date has passed.
  - Do not use the autoinjector if:
    - the white cap is missing or loose in carton,
    - it has cracks or broken parts, or
    - it has been dropped on a hard surface.

Getting Ready to Inject ENBREL

6 Gather and place the following items for your injection on a clean, flat, and well-lit surface:
  - ENBREL autoinjector (room temperature),
  - Sharps disposal container [see Completing the Injection and Disposal],
  - Alcohol wipe,
  - Adhesive bandage, and
  - Cotton balls or gauze pads.

7 Select 1 of these injection sites.
  - Select the thigh or stomach (except for 2 inches around the belly button).
  - Someone else can inject in your thigh, stomach, or back of the upper arm.
  - Change injection site each time, shifting the area of the injection to avoid skin irritation.

Important: Avoid areas with scars or stretch marks, or where the skin is tender, bruised, red, hard, raised, thick or scaly skin patch, or lesion.

8 Wash your hands thoroughly with soap and water.

9 Clean the injection site with an alcohol wipe.
  - Let the skin dry on its own.
  - Do not touch this area again before injecting.

Injecting ENBREL

Important: Only remove the white cap when you can inject right away (within 5 minutes) because the medicine can dry out. Do not recap.

10 Grasp the autoinjector so you can see the window. Pull the white cap straight off. You may need to pull hard.
  - Do not twist, bend, or wiggle the white cap to pull it off.
  - Never put the white cap back on. It may damage the needle.
  - Do not put your finger inside the dark green safety guard.
  - It is normal to see a drop of medicine come out of the needle or dark green safety guard.

11 Stretch or pinch the skin to create a firm surface at the injection site until the injection is finished. Place the dark green safety guard straight against the skin.
  - Make sure you can see the window.
  - Make sure the autoinjector is positioned straight on the injection site (at a 90-degree angle).

PUSH
and hold against skin

12 Firmly push the autoinjector down until the dark green safety guard stops moving. Hold the autoinjector down, do not lift.
  - The dark green safety guard pushes in and unlocks the purple start button.

PRESS
purple start button

13 Keep pushing the autoinjector down and press the purple start button to start the injection.
  - You may hear or feel a click.
  - The window starts to turn yellow.
  - It is okay to let go of the purple start button.

WATCH
window will turn fully yellow

14 Keep pushing the autoinjector down. Wait for the window to turn fully yellow.
  - The injection may take up to 15 seconds to complete.
  - You may hear or feel a click.
  - After the window turns fully yellow, lift the autoinjector away from the skin.
  - The dark green safety guard locks around the needle.

Completing the Injection and Disposal

CONFIRM

15 Confirm a full dose of medicine was injected.
  - Do not touch the dark green safety guard.
  - A small drop of liquid on the injection site is okay.

Important: If the window has not turned fully yellow or if it looks like the medicine is still coming out, a full dose was not injected. Call your healthcare provider right away.

16 Check the injection site.
  - Do not rub the injection site.
  - If there is blood, press a cotton ball or gauze pad on your injection site.
  - Apply an adhesive bandage if necessary.

17 Place the used autoinjector and white cap in an FDA-cleared sharps disposal.
  Important: Do not throw away the autoinjector in your household trash.
  - Do not reuse the autoinjector.
  - Do not touch the dark green safety guard.

Additional information about your sharps disposal container

If you do not have an FDA-cleared sharps disposal container, you may use a household container that is:

- made of a heavy-duty plastic,
- can be closed with a tight-fitting, puncture-resistant lid, without sharps being able to come out,
- upright and stable during use,
- leak-resistant, and
- properly labeled to warn of hazardous waste inside the container.

Disposing of sharps disposal containers:

When your sharps disposal container is almost full, you will need to follow your community guidelines for the right way to dispose of your sharps disposal container.

There may be state or local laws about how you should throw away used needles and syringes.

For more information about safe sharps disposal, and for specific information about sharps disposal in the state that you live in, go to the FDA's website at:

http://www.fda.gov/safesharpsdisposal

Do not dispose of your used sharps disposal container in your household trash unless your community guidelines permit this.

Do not recycle your used sharps disposal container.

Keep the autoinjector and sharps disposal container out of the sight and reach of children.

For more information or help call 1-888-4ENBREL (1-888-436-2735).

ENBREL (etanercept)

AMGEN

Manufactured by:
Immunex Corporation
Thousand Oaks, CA 91320-1799
U.S. License Number 1132
©1998–2016, 2019-2025 Immunex Corporation. All rights reserved.
1XXXXXX

This Instructions for Use has been approved by the U.S. Food and Drug Administration.
Revised: 6/2025 v21

Instructions for Use Enbrel® (en-brel) (etanercept) injection, for subcutaneous use Single-dose Prefilled Syringe

How do I prepare and give an injection with Enbrel Single-dose Prefilled Syringe?

There are 2 types of Enbrel single-dose prefilled syringes:

- The 50 mg/mL single-dose prefilled syringe that contains one 50 mg dose of Enbrel.
- The 25 mg/0.5 mL single-dose prefilled syringe that contains one 25 mg dose of Enbrel.

Your healthcare provider will tell you which one to use.

A 50 mg dose can be given as one injection using a 50 mg/mL single-dose prefilled syringe or as two injections using 25 mg/0.5 mL single-dose prefilled syringes. Your healthcare provider will tell you whether the two injections with 25 mg/0.5 mL single-dose prefilled syringes should be given on the same day once a week or on two different days (3 or 4 days apart) in the same week.

Children must weigh at least 138 pounds to use the Enbrel 50 mg/mL single-dose prefilled syringe. Children who weigh less than 138 pounds should use a different form of Enbrel. The Enbrel 25 mg/0.5 mL single-dose prefilled syringe should not be used in pediatric patients weighing less than 68 pounds.

Important: The Enbrel prefilled syringe is not made with natural rubber latex.

Storage of your Enbrel prefilled syringe

- Store the Enbrel prefilled syringe in the refrigerator at 36°F to 46°F (2°C to 8°C).
- Store the Enbrel prefilled syringe in the original carton to protect from light or physical damage.
- If needed, you may store your Enbrel prefilled syringe at room temperature between 68°F to 77°F (20°C to 25°C) for up to 30 days.
  - Once the Enbrel prefilled syringe has reached room temperature, do not put it back in the refrigerator.
- Throw away any Enbrel prefilled syringe that has been stored at room temperature after 30 days.
- Do not store the Enbrel prefilled syringe in extreme heat or cold. For example, avoid storing Enbrel prefilled syringe in your vehicle's glove box or trunk.
- Do not freeze.
- Do not shake.
- Keep the Enbrel prefilled syringe and all medicines out of the reach of children.

If you have any questions about storage, contact your healthcare provider or call 1-888-4ENBREL (1-888-436-2735) for further instructions.

Step 1: Setting Up for an Injection

1. Select a clean, well-lit, flat work surface, such as a table.
2. Take the Enbrel carton containing the prefilled syringes out of the refrigerator and place it on your flat work surface. Remove one prefilled syringe and place it on your work surface. Carefully lift the prefilled syringe straight up out of the box. Do not shake the prefilled syringe of Enbrel. Place the carton containing any remaining prefilled syringes back into the refrigerator at 36°F to 46°F (2°C to 8°C).
3. Check the expiration date on the prefilled syringe. If the expiration date has passed, do not use the prefilled syringe and contact your pharmacist or call 1-888-4ENBREL (1-888-436-2735) for assistance.
4. Do not use the prefilled syringe if the needle cover is missing or not securely attached. Call 1-888-4ENBREL (1-888-436-2735).
5. For a more comfortable injection, leave the prefilled syringe at room temperature for about 15 to 30 minutes before injecting. Do not remove the needle cover while allowing it to reach room temperature. Do not warm Enbrel in any other way (for example, do not warm it in a microwave or in hot water).
6. Hold the prefilled syringe with the covered needle pointing down. If bubbles are seen in the syringe, very gently tap the prefilled syringe to allow any bubbles to rise to the top of the syringe. Turn the syringe so that the purple horizontal lines on the barrel are directly facing you. Check to see if the amount of liquid in the syringe falls between the purple lines. The top of the liquid may be curved. If the syringe does not have the right amount of liquid, do not use that syringe. Contact your pharmacist or call 1-888-4ENBREL (1-888-436-2735) for assistance.
  Fill Level Indicator
7. Assemble the additional supplies you will need for your injection. These include an alcohol swab, a cotton ball or gauze, and a sharps disposal container (see "Step 4: Disposing of Supplies").
8. Wash your hands with soap and warm water.
9. Make sure the solution in the prefilled syringe is clear and colorless. You may notice small white particles in the solution. These particles are formed from Enbrel and this is acceptable. However, do not inject the solution if it is cloudy or discolored, or contains large or colored particles, call 1-888-4ENBREL (1-888-436-2735).

Step 2: Choosing and Preparing an Injection Site

1. Recommended injection sites for Enbrel using a prefilled syringe include:
  - the front of the middle thigh
  - the stomach area (abdomen), except for the 2-inch area right around the navel (belly button)
  - the outer area of the upper arm (only if someone else is giving you the injection)
    Front Back
2. Rotate the site for each injection. Do not inject into areas where the skin is tender, bruised, red, or hard. Avoid areas with scars or stretch marks.
3. If you have psoriasis, you should not inject directly into any raised, thick, red, or scaly skin patches or lesions.
4. To prepare the area of skin where Enbrel is to be injected, wipe the injection site with an alcohol swab. Do not touch this area again before giving the injection.

Step 3: Injecting Enbrel Using a Prefilled Syringe

Do not remove the needle cover from the prefilled syringe until you are ready to inject.

1. Pick up the prefilled syringe from your flat work surface. Hold the barrel of the prefilled syringe with one hand and pull the needle cover straight off, only when you are ready to inject. Do not leave the needle cover off for more than 5 minutes. This can dry out the medicine.
  To avoid damaging the needle, do not twist or bend the needle cover while you are removing it, and do not try to put the needle cover back onto the prefilled syringe.
  When you remove the needle cover, there may be a drop of liquid at the end of the needle; this is normal. Do not touch the needle or allow it to touch any surface. Do not touch or bump the plunger. Doing so could cause the liquid to leak out.
2. Holding the syringe with the needle pointing up, check the syringe for air bubbles. If there are bubbles, gently tap the syringe with your finger until the air bubbles rise to the top of the syringe. Slowly push the plunger up to force the air bubbles out of the syringe.
3. Holding the syringe in one hand like a pencil, use the other hand to gently pinch a fold of skin at the cleaned injection site and hold it firmly.
4. With a quick and "dart-like" motion, insert the needle at a 45-degree angle into the skin.
5. When the needle is completely inserted into the skin, let go of the skin that you are holding. With your free hand, hold the syringe near its base to stabilize it. Then push the plunger to inject all of the Enbrel solution at a slow, steady rate.
6. When the syringe is empty, pull the needle out of the skin, being careful to keep it at the same angle as inserted. There may be a little bleeding at the injection site. You can press a cotton ball or gauze over the injection site for 10 seconds. Do not rub the injection site. If needed, you may cover the injection site with a bandage.

Step 4: Disposing of Supplies

The syringe should never be reused. Never recap a needle.

- Put the used prefilled syringes in a FDA-cleared sharps disposal container right away after use. Do not throw away (dispose of) prefilled syringes in your household trash.
- If you do not have a FDA-cleared sharps disposal container, you may use a household container that is:
  - made of a heavy-duty plastic,
  - can be closed with a tight-fitting, puncture-resistant lid, without sharps being able to come out,
  - upright and stable during use,
  - leak-resistant, and
  - properly labeled to warn of hazardous waste inside the container.
- When your sharps disposal container is almost full, you will need to follow your community guidelines for the right way to dispose of your sharps disposal container. There may be state or local laws about how you should throw away used syringes and needles. For more information about safe sharps disposal, and for specific information about sharps disposal in the state that you live in, go to the FDA's website at: http://www.fda.gov/safesharpsdisposal
- Do not reuse the syringe.
- Do not recycle the syringe or sharps disposal container or throw them into household trash.

Important: Always keep the sharps disposal container out of the reach of children.

A healthcare provider familiar with Enbrel should answer all questions. Call 1-888-4ENBREL (1-888-436-2735) or visit www.enbrel.com for more information about Enbrel.

This Instructions for Use have been approved by the U.S. Food and Drug Administration.

AMGEN

Manufactured by:
Immunex Corporation
Thousand Oaks, CA 91320-1799
U.S. License Number 1132
© 1998 – 2016, 2019-2020, 2022-2024 Immunex Corporation. All rights reserved.

1XXXXXX – v13
Revised: 10/2024

This printed material is recyclable.

Instructions for Use Enbrel® (en-brel) (etanercept) for injection, for subcutaneous use Multiple-dose Vial

How do I prepare and give an injection with Enbrel multiple-dose vial?

A multiple-dose vial contains 25 mg of Enbrel.

Storage of Enbrel multiple-dose vial

- Store Enbrel multiple-dose vial in the refrigerator at 36°F to 46°F (2°C to 8°C).
- Store Enbrel multiple-dose vial in the original carton to protect from light or physical damage.
- If needed, you may store your Enbrel multiple-dose vial and diluent syringe (dose tray) at room temperature between 68°F to 77°F (20°C to 25°C) for up to 14 days.
  ○ Once Enbrel multiple-dose vial has reached room temperature, do not put it back in the refrigerator.
- Throw away Enbrel multiple-dose vial that has been stored at room temperature after 14 days.
- Mixed (reconstituted) Enbrel multiple-dose vial should be used right away or kept in the refrigerator at 36°F to 46°F (2°C to 8°C) for up to 14 days.
- Do not store Enbrel multiple-dose vial in extreme heat or cold. For example, avoid storing Enbrel multiple-dose vial in your vehicle’s glove box or trunk.
- Do not freeze.
- Do not shake.
- Keep Enbrel multiple-dose vial and all medicines out of the reach of children.

If you have any questions about storage, contact your healthcare provider or call 1-888-4ENBREL (1-888-436-2735) for further instructions.

Step 1: Setting Up for an Injection

1. Select a clean, well-lit, flat work surface, such as a table.
2. Take the Enbrel dose tray out of the refrigerator and place it on your flat work surface.
3. Check the expiration date on the dose tray. If the expiration date has passed, do not use the dose tray. Also check to make sure the dose tray has 5 items as pictured below:
  • One prefilled diluent syringe containing 1 mL of diluent (liquid) with attached adapter and twist-off cap
  • One plunger
  • One Enbrel vial
  • One 27-gauge ½ inch needle in hard plastic cover
  • One vial adapter
  If the expiration date has passed, the five items are not included in the dose tray or if any item looks damaged, contact your pharmacist or call 1-888-4ENBREL (1-888-436-2735) for assistance.
4. For a more comfortable injection, leave the dose tray at room temperature for about 15 to 30 minutes before injecting.
5. Wash your hands with soap and warm water.
6. Peel the paper seal off the dose tray and remove all items.
7. Inspect the volume of diluent in the syringe with the twist-off cap pointing down. Use the unit markings on the side of the syringe to make sure there is at least 1 mL of liquid in the syringe. If the level of liquid is below the 1 mL mark, do not use. Contact your pharmacist or call 1-888-4ENBREL (1-888-436-2735) for assistance.
8. Do not use the syringe if the twist-off cap is missing or not securely attached. Call 1-888-4ENBREL (1-888-436-2735).
9. Two alcohol swabs should be available for the preparation and injection of Enbrel. Alcohol swabs can be found at your local drug store.

Step 2: Preparing the Enbrel Solution

There are two methods for preparing the Enbrel solution. For some children, one vial of Enbrel solution can be used for more than one dose. The free-hand method should be used for children on Enbrel who are using one vial of Enbrel solution for more than one dose. You should not use the vial adapter method if you will be using the vial more than once. Ask your healthcare provider if you have questions about which method to use.

- The Vial Adapter Method

Adults and larger children on Enbrel may use the vial adapter device to assist with mixing the powder with the liquid and withdrawing Enbrel, and then use a 27-gauge needle to inject the dose. This method should not be used for children using multiple doses from the same vial of Enbrel. The instructions for using the vial adapter method are in Step 2A.

- The Free-Hand Method

In the free-hand method, a 25-gauge needle is used to assist with mixing the powder with the liquid and withdrawing Enbrel, and a 27-gauge needle is used to inject the dose. Obtain 25-gauge needles from your healthcare provider. Instructions for using the free-hand method are in Step 2B.

The instructions for preparing additional doses from the same vial of Enbrel solution are in Step 3. For each additional dose, you will need two new needles (one 25-gauge needle to withdraw the solution and one 27-gauge needle for injection) and one new empty syringe (1 mL). Never reuse a syringe or needle.

If you are using the vial of Enbrel for more than one dose, you should write the date you mixed the powder and liquid in the area marked “Mixing Date:” on the sticker supplied with these instructions, and attach the sticker to the Enbrel vial.

After you have withdrawn the dose of Enbrel that you need, store the Enbrel vial (in the dose tray) in the refrigerator at 36º to 46ºF (2º to 8ºC) as soon as possible, but always within 4 hours of mixing the solution. Do not freeze. If you have any questions about storage, contact your healthcare provider or call 1-888-4ENBREL (1-888-436-2735) for further instructions.

The Enbrel solution must be used within 14 days of the mixing date. You should discard the Enbrel vial and any remaining solution if it is not used within 14 days. Do not mix any remaining liquid in one vial of Enbrel solution with another.

STEP 2A: Vial Adapter Method

1. Remove the pink plastic cap from the Enbrel vial. Do not remove the gray stopper or silver metal ring around the top of the Enbrel vial.
2. Place the Enbrel vial on your flat work surface or turn your dose tray upside down and place your Enbrel vial in the round space marked “V”. Use one alcohol swab to clean the gray stopper on the Enbrel vial. Do not touch the gray stopper with your hands.
3. Open the wrapper that contains the 27-gauge needle by peeling apart the tabs and set the needle aside for later use.
4. Open the wrapper that contains the vial adapter by peeling apart the tabs and set the vial adapter aside for later use. Do not touch the vial adapter’s twist-on end or the spike inside.
5. Slide the plunger into the flange end of the syringe.
6. Attach the plunger to the gray rubber stopper in the syringe by turning the plunger clockwise until you feel a slight resistance.
7. Remove the twist-off cap from the prefilled diluent syringe by turning counter-clockwise. Do not bump or touch the plunger. Doing so could cause the liquid to leak out. You may see a drop of liquid when removing the cap. This is normal. Place the cap on your flat work surface. Do not touch the syringe tip.
8. Once the twist-off cap is removed, pick up the vial adapter with your free-hand. Twist the vial adapter onto the syringe, turning clockwise until you feel a slight resistance. Do not over-tighten.
9. Hold the Enbrel vial upright on your flat work surface. Grasp the sides of the vial adapter and place it over the top of the Enbrel vial. Do not bump or touch the plunger. Doing so could cause the liquid to leak out. Insert the vial adapter into the gray stopper on the Enbrel vial. The plastic spike inside the vial adapter should puncture the gray stopper. The vial adapter should fit snugly.
10. Hold the Enbrel vial upright on your flat work surface and push the plunger down until all the liquid from the syringe is in the Enbrel vial. You may see foaming (bubbles) in the vial. This is normal.
11. Gently swirl the Enbrel vial in a circular motion to dissolve the powder. If you used the dose tray to hold your Enbrel vial, take the vial (with the vial adapter and syringe still attached) out of the dose tray, and gently swirl the vial in a circular motion to dissolve the powder.
  Do not shake. Wait until all the powder dissolves (usually less than 10 minutes). The solution should be clear and colorless. After the powder has completely dissolved, foam (bubbles) may still be present. This is normal. Do not inject the solution if it is discolored, contains lumps, flakes, or particles. If all the powder in the Enbrel vial is not dissolved or there are particles present after 10 minutes, call 1-888-4ENBREL (1-888-436-2735).
12. Turn the Enbrel vial upside down. Hold the syringe at eye level and slowly pull the plunger down to the unit markings on the side of the syringe that correspond with your/your child’s dose. For adult patients, remove the entire volume (1 mL), unless otherwise instructed by your healthcare provider. Be careful not to pull the plunger completely out of the syringe. Some white foam may remain in the Enbrel vial. This is normal.
13. Check for air bubbles in the syringe. Gently tap the syringe to make any air bubbles rise to the top of the syringe. Slowly push the plunger up to remove the air bubbles. If you push solution back into the vial, slowly pull back on the plunger to again draw the correct amount of solution back into the syringe.
14. Remove the syringe from the vial adapter, by holding the vial adapter with one hand and turning the syringe counter-clockwise with your other hand. Do not touch or bump the plunger. Place the Enbrel vial with the vial adapter on your flat work surface.
15. Continue to hold the barrel of the syringe. With your free-hand, twist the 27-gauge needle onto the tip of the syringe until it fits snugly. Do not remove the needle cover from the syringe. Place the syringe on your flat work surface until you are ready to inject Enbrel.

Go to Step 4: Choosing and Preparing an Injection Site.

Step 2B: Free-Hand Method

If you are preparing a dose from an Enbrel vial that was previously used, go to Step 3: Preparing Additional Doses from a Single Enbrel Vial.

1. Remove the pink plastic cap from the Enbrel vial. Do not remove the gray stopper or silver metal ring around the top of the Enbrel vial. Write the date you mix the powder and solution on the supplied “Mixing Date:” sticker and attach it to the Enbrel vial.
2. Place the Enbrel vial on your flat work surface. Use one alcohol swab to clean the gray stopper on the Enbrel vial. Do not touch the gray stopper with your hands.
3. Open the wrapper that contains the 25-gauge needle by peeling apart the tabs and set the needle aside for later use. The 25-gauge needle will be used to mix the liquid with the powder and for withdrawing Enbrel from the vial.
4. Slide the plunger into the flange end of the syringe.
5. Attach the plunger to the gray rubber stopper in the syringe by turning the plunger clockwise until you feel a slight resistance.
6. Remove the twist-off cap from the prefilled diluent syringe by turning counter-clockwise. Do not touch or bump the plunger. Doing so could cause the liquid to leak out. You may see a drop of liquid when removing the cap. This is normal. Place the cap on your flat work surface. Do not touch the syringe tip.
7. Continue to hold the barrel of the syringe. With your free-hand, twist the 25-gauge needle onto the tip of the syringe until it fits snugly. Place the syringe on your flat work surface.
8. Open the wrapper that contains the 27-gauge needle by peeling apart the tabs and set the needle aside for later use. The 27-gauge needle will be used to inject the dose.
9. Pick up the syringe from your flat work surface. Hold the barrel of the syringe with one hand, and pull the needle cover straight off. To avoid damaging the needle, do not twist or bend the needle cover while you are removing it. Do not touch the needle or allow it to touch any surface. Do not touch or bump the plunger. Doing so could cause the liquid to leak out.
10. Place the needle cover (open side up) in the round space marked “N” in the Enbrel dose tray.
11. Place the Enbrel vial on your flat work surface. Hold the syringe with the needle facing up, and gently pull back on the plunger to pull a small amount of air into the syringe. Then, insert the needle straight down through the center ring of the gray stopper (see illustrations). You should feel a slight resistance and then a “pop” as the needle goes through the center of the stopper. Look for the needle tip inside the open stopper window. If the needle is not correctly lined up with the center of the stopper, you will feel constant resistance as it goes through the stopper and no “pop”. The needle may enter at an angle and bend, break or prevent you from adding diluent into the Enbrel vial.
12. Push the plunger down very slowly until all liquid from the syringe is in the Enbrel vial. Adding the liquid too fast will cause foaming (bubbles).
13. Leave the syringe in place. Gently swirl the Enbrel vial in a circular motion to dissolve the powder.
  Do not shake. Wait until all the powder dissolves (usually less than 10 minutes). The solution should be clear and colorless. After the powder has completely dissolved, foam (bubbles) may still be present. This is normal. Do not inject the solution if it is discolored, contains lumps, flakes, or particles. If all the powder in the Enbrel vial is not dissolved or there are particles present after 10 minutes, call 1-888-4ENBREL (1-888-436-2735).
14. With the needle in the Enbrel vial, turn the vial upside down. Hold the syringe at eye level and slowly pull the plunger down to the unit markings on the side of the syringe that correspond with the correct dose. Make sure to keep the tip of the needle in the solution. Some white foam may remain in the Enbrel vial. This is normal.
15. With the needle still inserted in the Enbrel vial, check for air bubbles in the syringe. Gently tap the syringe to make any air bubbles rise to the top of the syringe. Slowly push the plunger up to remove the air bubbles. If you push solution back into the vial, slowly pull back on the plunger to draw the correct amount of solution back into the syringe.
16. Remove the syringe and needle from the Enbrel vial. Keep the needle attached to the syringe and insert the 25-gauge needle straight down into the needle cover in the Enbrel dose tray.
  You should hear a “snap” when the needle is secure in the needle cover. Once the needle is secure in the needle cover, untwist the 25-gauge needle from the syringe and dispose of the needle in your sharps disposal container (see “Step 6: Disposing of Supplies”).
17. Twist the 27-gauge needle onto the syringe until it fits snugly. Do not remove the needle cover from the syringe. Place the syringe on your flat work surface until you are ready to inject Enbrel.
18. If there is enough solution left in the Enbrel vial for another dose, write the date you mixed the powder and liquid in the area marked “Mixing Date:” on the sticker supplied with these instructions, and attach the sticker to the Enbrel vial. Refrigerate the reconstituted (mixed) Enbrel vial (in the dose tray) after mixing. Prepare additional doses from the Enbrel vial as described in Step 3. Otherwise, throw away (discard) the Enbrel vial and any remaining solution.

Go to Step 4: Choosing and Preparing an Injection Site.

Step 3: Preparing Additional Doses from a Single Enbrel Vial

1. Select a clean, well-lit, flat work surface, such as a table.
2. Do not reuse the needles and syringes supplied with Enbrel dose tray. You will need new needles and syringes for each additional dose. Your healthcare provider will tell you what type of syringes (1 mL) and needles (25-gauge and 27-gauge) to use. Place the sterile syringe with a 25-gauge needle (for withdrawing Enbrel), a 27-gauge needle (for injecting Enbrel) and two alcohol swabs on your flat work surface.
3. Take the vial of Enbrel solution that is stored in the dose tray out of the refrigerator and place it on your flat work surface.
4. Check the mixing date you wrote on the sticker on the Enbrel vial. Discard the Enbrel vial if more than 14 days have passed since the Enbrel solution was mixed.
5. Wash your hands with soap and warm water.
6. Use one alcohol swab to clean the gray stopper on the Enbrel vial. Do not touch the stopper with your hands.
7. If the syringe and the 25-gauge needle are not pre-assembled, assemble them as instructed by your healthcare provider.
8. Open the wrapper that contains the 27-gauge needle by peeling apart the tabs and set the needle aside for later use. The 27-gauge needle will be used to inject the dose of Enbrel.
9. Hold the syringe and pull the needle cover straight off. To avoid damaging the needle, do not twist or bend the needle cover while you are removing it. Do not touch the needle or allow it to touch any surface. Place the needle cover (open side up) in the round space marked “N” in the Enbrel dose tray.
10. Place the Enbrel vial on your flat work surface. Hold the syringe with the needle facing up, and gently pull back the plunger to pull a small amount of air into the syringe. Then, insert the 25-gauge needle straight down through the center ring of the gray stopper. You should feel a slight resistance and then a “pop” as the needle goes through the center of the stopper. Look for the needle tip inside the open stopper window. If the needle is not correctly lined up with the center of the stopper, you will feel constant resistance as it goes through the stopper and no “pop”. The needle may enter at an angle and bend, break, or prevent proper withdrawal of Enbrel solution from the vial.
11. Keep the needle in the Enbrel vial and turn the vial upside down. Hold the syringe at eye level, and slowly pull the plunger down to the unit markings on the syringe that correspond to your child’s dose. As the amount of solution in the Enbrel vial drops, you may need to pull the needle back just enough to keep the tip of the needle in the solution.
12. With the needle still inserted in the Enbrel vial, check for air bubbles in the syringe. Gently tap the syringe to make any air bubbles rise to the top of the syringe. Slowly push the plunger up to remove the air bubbles. If you push solution back into the Enbrel vial, slowly pull back on the plunger to again draw the correct amount of solution back into the syringe.
13. Remove the syringe and needle from the Enbrel vial. Keep the needle attached to the syringe and insert the 25-gauge needle straight down into the needle cover in the Enbrel dose tray. You should hear a “snap” when the needle is secure in the needle cover. Once the needle is secure in the needle cover, remove the 25-gauge needle from the syringe and dispose of the needle in a sharps disposal container (see “Step 6: Disposing of Supplies”).
14. Attach the 27-gauge needle onto the tip of the syringe until it fits snugly. Do not remove the needle cover from the syringe. Place the syringe on your flat work surface until you are ready to inject Enbrel.

Step 4: Choosing and Preparing an Injection Site

1. The 3 recommended injection sites for Enbrel include:
  • the front of the middle thighs
  • the stomach area (abdomen), except for the 2-inch area right around the navel (belly button)
  • the outer area of the upper arms (only if someone else is giving you the injection)
2. Rotate the site for each injection. Do not inject into areas where the skin is tender, bruised, red, or hard. Avoid areas with scars or stretch marks.
3. If you have psoriasis, you should not inject directly into any raised, thick, red, or scaly skin patches or lesions.
4. To prepare the area of skin where Enbrel is to be injected, wipe the injection site with a new alcohol swab. Do not touch this area again before giving the injection.

Step 5: Injecting the Enbrel Solution

Do not remove the needle cover from the syringe until you are ready to inject.

1. Pick up the syringe from your flat work surface. Hold the barrel of the syringe with one hand and pull the needle cover straight off. To avoid damaging the needle, do not twist or bend the needle cover while you are removing it, and do not try to put the needle cover back onto the syringe. When you remove the needle cover, there may be a drop of liquid at the end of the needle. This is normal. Do not touch the needle or allow it to touch any surface. Do not touch or bump the plunger. Doing so could cause the liquid to leak out.
2. With one hand, gently pinch the cleaned area of skin and hold it firmly. With the other hand, hold the syringe (like a pencil) at a 45-degree angle to the skin.
3. With a quick and "dart-like" motion, insert the needle at a 45-degree angle into the skin.
4. When the needle is completely inserted into the skin, let go of the skin that you are holding. With your free-hand, hold the syringe near its base to stabilize it. Then push the plunger to inject all of the Enbrel solution at a slow, steady rate.
5. When the syringe is empty, pull the needle out of the skin, being careful to keep it at the same angle as inserted.
6. There may be a little bleeding at the injection site. You can press a cotton ball or gauze over the injection site for 10 seconds. Do not rub the injection site. If needed, you may cover the injection site with a bandage.
7. If your healthcare provider has instructed you to take two Enbrel injections on the same day, repeat the steps to prepare and give an injection of Enbrel. Choose and prepare a new injection site for the second injection.
8. For the Free-Hand Method: If there is enough solution left in the Enbrel vial for another dose, refrigerate the reconstituted (mixed) Enbrel vial (in the dose tray) after use. Otherwise, discard the Enbrel vial and any remaining solution.

Step 6: Disposing of Supplies

The syringe, needles, and vial adapter should never be reused. Never recap a needle.

- Put the used syringes, needles, and vials in a FDA-cleared sharps disposal container right away after use. Do not throw away (dispose of) the needles, syringes, and vials in your household trash.
- If you do not have a FDA-cleared sharps disposal container, you may use a household container that is:
  ○ made of a heavy-duty plastic,
  ○ can be closed with a tight-fitting, puncture-resistant lid, without sharps being able to come out,
  ○ upright and stable during use,
  ○ leak-resistant, and
  ○ properly labeled to warn of hazardous waste inside the container.
- When your sharps disposal container is almost full, you will need to follow your community guidelines for the right way to dispose of your sharps disposal container. There may be state or local laws about how you should throw away used syringes and needles. For more information about safe sharps disposal, and for specific information about sharps disposal in the state that you live in, go to the FDA’s website at: http://www.fda.gov/safesharpsdisposal
- Do not reuse the syringe or vial.
- Do not recycle the syringe, vial, or sharps disposal container or throw them into household trash.

Important: Always keep the sharps disposal container out of the reach of children.

A healthcare provider familiar with Enbrel should answer all questions. Call 1-888-4ENBREL (1-888-436-2735) or visit www.enbrel.com for more information about Enbrel.

This Instructions for Use have been approved by the U.S. Food and Drug Administration.

AMGEN®

Manufactured by:
Immunex Corporation
Thousand Oaks, CA 91320-1799
U.S. License Number 1132

© 1998 – 2016, 2019 Immunex Corporation. All rights reserved.

1XXXXXX – v9

Revised: 10/2019

This printed material is recyclable.

Flip over for
additional information

INSTRUCTIONS FOR USE ENBREL® [en-brel] (etanercept) injection, for subcutaneous use 50 mg/mL ENBREL Mini® Single-dose Prefilled Cartridge for use with all AutoTouch® Reusable Autoinjectors

This Instructions for Use contains information on how to inject the ENBREL Mini single-dose prefilled cartridge with all AutoTouch reusable autoinjectors.

If your healthcare provider decides that ENBREL injections may be given at home, you or your caregiver should receive training on the right way to prepare and inject ENBREL. Do not try to inject until you or your caregiver have been shown the right way to give the injections by your healthcare provider or nurse.

The medicine in the ENBREL Mini single-dose prefilled cartridge is for injection under the skin (subcutaneous injection). See the ENBREL Medication Guide for information about ENBREL.

AutoTouch® Reusable Autoinjector

To learn more about autoinjector features, see the User Manual, section "Guide to Parts."

Enbrel Mini® Single-dose Prefilled Cartridge

Important: Do not remove the purple needle cap until step 11.

To learn more about cartridge features, see the User Manual, section "Guide to Parts."

Frequently asked questions

For additional information and answers to frequently asked questions, visit www.enbrel.com.

Where to get help

If you want more information or help using ENBREL:

- Contact your healthcare provider,
- Visit www.enbrel.com, or
- Call 1-888-4ENBREL (1-888-436-2735).

Preparing ENBREL

WAIT

1 Wait 30 minutes for the cartridge to reach room temperature.
  - Remove 1 cartridge from the carton in the refrigerator.
  - Put the carton containing any unused cartridges back in the refrigerator.
  - Let the cartridge warm up naturally.
  - Do not heat the cartridge with hot water, a microwave, or direct sunlight.
  - Do not put the cartridge back in the refrigerator once it reaches room temperature.

2 Inspect the medicine. It should be clear and colorless.
  - It is okay to see air bubbles.
  - Do not use the cartridge if the medicine is cloudy, discolored, or contains large lumps, flakes, or colored particles.
  - It is okay to see small white particles in the medicine.

Important: If the medicine is cloudy, discolored, contains large lumps, flakes, colored particles, or if the cartridge is damaged or expired, call 1-888-4ENBREL (1-888-436-2735).

Expiration date

3 Check the expiration date (Exp.) and inspect the cartridge for damage.
  - Do not use the cartridge if the expiration date has passed.
  - Do not use the cartridge if:
    - the purple needle cap is missing or loose,
    - it has cracks or broken parts, or
    - it has been dropped on a hard surface.

4 Gather and place the following items for the injection on a clean, flat, and well-lit surface:
  - AutoTouch reusable autoinjector,
  - 1 Enbrel Mini cartridge (room temperature),
  - Sharps disposal container [see Completing the Injection],
  - 3 Alcohol wipes,
  - Adhesive bandage, and
  - Cotton balls or gauze pads.

5 Wash your hands thoroughly with soap and water.

Getting Ready to Inject ENBREL

6 Clean the injection end of the autoinjector with an alcohol wipe.
  - Let the injection end dry on its own.
  - Do not touch this area again before injecting.
  - Do not use the autoinjector if:
    - the expiration date has passed,
    - it has cracks or broken parts, or
    - it has been dropped on a hard surface.

7 Press the door button to open the autoinjector door.
  - Do not block the door while pushing the door button.

8 Insert the cartridge with the purple needle cap down and the labeled side facing out.
  - The cartridge will slide all the way down into the autoinjector.
  - Do not force the cartridge into the autoinjector door.
  - Once the cartridge is inserted, push the door to close it.
  - Do not remove the purple needle cap until step 11.

If the status button flashes red, see the User Manual, section "Troubleshooting."

9 Select 1 of these injection site locations.
  - You can inject into the:
    - Stomach (at least 2 inches away from the belly button), or
    - Thigh.
  - Another person may give you the injection in the back of your upper arm.
  - Choose a different site for each injection.

Important: Avoid areas with scars, stretch marks, where the skin is tender, bruised, red, hard, or areas with psoriasis.

10 Clean the injection site with a new alcohol wipe.
  - Let the skin dry on its own.
  - Do not touch this area again before injecting.

Injecting ENBREL

Important: Only remove the purple needle cap when you can inject right away (within 5 minutes) as the medicine can dry out. Do not recap.

11 Pull the purple needle cap straight down to remove.
  - Do not twist or bend the purple needle cap to pull it off.
  - Never put the purple needle cap back on. It may damage the needle.
  - It is normal to see a drop of medicine come out of the needle or injection end of the autoinjector.

Important: Keep your thumb away from the status button until you are ready to inject.

12 With the progress bar facing you, place and hold the autoinjector on the injection site.
  - After placing on the skin, wait for the:
    - status button to turn green,
    - progress bar to turn green, and
    - chime sound (will not chime if sound switch is off).
  - Do not stretch or pinch the injection site.

If the status button does not turn green, see the User Manual, section "Troubleshooting."

13 Press and release the status button to inject.
  - Do not lift the autoinjector from the skin until the injection is complete.
  - During the injection:
    - the green status button will flash on and off,
    - the progress bar lights will decrease, and
    - you will hear a motor noise.
  - The injection may take up to 20 seconds to complete.

14 Keep holding flat on the skin until the status button and progress bar turn off.
  - The injection is complete when the:
    - status button turns off,
    - progress bar turns off, and
    - chime sounds (will not chime if sound switch is off).
  - Lift it from the skin when the injection is complete.
  - Do not block the door, it will open automatically.

Important: When you remove the autoinjector, if the status button is flashing red either see the User Manual, section "Troubleshooting" or call 1-888-4ENBREL (1-800-436-2735).

Completing the Injection

15 Remove the used cartridge and confirm a full dose of medicine was injected.
  - When the door opens, remove the used cartridge and close the door.
  - A small drop of liquid on the injection site is okay.

Important: If it looks like the medicine is still injecting or if you see medicine in the cartridge window, this means you may not have received a full dose. Call your healthcare provider right away.

16 Place the used cartridge and purple needle cap in an FDA-cleared sharps disposal container.
  - Do not reuse the cartridge.
  - Do not throw away the cartridge in your household trash.
  - Small parts such as the purple needle cap may cause a choking hazard for children and pets.

Important: Always keep the sharps disposal container out of the reach of children.

17 Check the injection site.
  - Do not rub the injection site.
  - If there is blood, press a cotton ball or gauze pad on the injection site.
  - Apply an adhesive bandage if necessary.

18 Clean the injection end of the autoinjector with a new alcohol wipe and let it dry.
  - Store the autoinjector at room temperature in a dry, safe place such as in a cabinet or drawer.
  - Do not store the autoinjector in the refrigerator.

Additional information about your sharps disposal container
If you do not have an FDA-cleared sharps disposal container, you may use a household container that is:

- made of a heavy-duty plastic,
- can be closed with a tight-fitting, puncture-resistant lid, without sharps being able to come out,
- upright and stable during use,
- leak-resistant, and
- properly labeled to warn of hazardous waste inside the container.

Disposing of sharps disposal containers:

When your sharps disposal container is almost full, you will need to follow your community guidelines for the right way to dispose of your sharps disposal container.

There may be state or local laws about how you should throw away used needles and syringes.

For more information about safe sharps disposal, and for specific information about sharps disposal in the state that you live in, go to the FDA's website at:
http://www.fda.gov/safesharpsdisposal

Do not dispose of your used sharps disposal container in your household trash unless your community guidelines permit this.

Do not recycle your used sharps disposal container.

Troubleshooting Error symbols: Why is the status button flashing red?

Low battery:

The battery is running very low. Less than 3 weeks or 3 injections remain. The battery is not replaceable or rechargeable.

Call 1-888-4ENBREL (1-888-436-2735) for a replacement autoinjector.

See the User Manual, section "Troubleshooting", for more information.

Needle exposure:

The needle may be exposed and an incomplete dose may have been injected. Look for medicine in the cartridge window. Call your healthcare provider if you feel you have given yourself an incomplete injection. Take special care when removing and handling the cartridge. Place the cartridge in an FDA-cleared sharps disposal container.

See the User Manual, section "Troubleshooting", for more information.

Enbrel Mini problem:

There are several reasons you might get this error.

See the User Manual, section "Troubleshooting", for more information.

Battery dead:

The battery is dead.

Call 1-888-4ENBREL (1-888-436-2735) for a replacement autoinjector.

See the User Manual, section "Troubleshooting", for more information.

Too hot or too cold:

The autoinjector is too hot or too cold. This will lock the door. Place the autoinjector at room temperature in a dry, safe place, and allow it to naturally cool or warm to room temperature. Then try again.

Store the autoinjector in a dry, safe place, such as a cabinet or drawer at 50°F to 104°F (10°C to 40°C).

See the User Manual, section "Troubleshooting", for more information.

Autoinjector detected problem:

See the User Manual, section "Troubleshooting", for reset instructions.

See the User Manual booklet for more information.

Flip over for additional information

For more information or help call 1-888-4ENBREL (1-888-436-2735).

Important Information You Need to Know Before Injecting ENBREL

The AutoTouch reusable autoinjector is used with the Enbrel Mini single-dose prefilled cartridge to administer your dose of ENBREL. The Enbrel Mini single-dose prefilled cartridge contains one 50 mg single-dose of ENBREL.

Before you use the AutoTouch reusable autoinjector with Enbrel Mini single-dose prefilled cartridge for use with ENBREL, read this important information:

- It is important that you do not try to give the injection until you have fully read and understood this Instructions for Use.
- Children must weigh at least 138 pounds to receive 50 mg Enbrel Mini. Children who weigh less than 138 pounds should receive a different form of ENBREL.
- Do not use the autoinjector or cartridges if either carton is damaged or either seal is broken.
- The autoinjector and the cartridge are not made with natural rubber latex.
- Do not use the autoinjector or cartridge if it has been dropped on a hard surface. Part of the autoinjector or cartridge may be broken even if you cannot see the break.
  - If the cartridge has been dropped, use a new cartridge and call 1-888-4ENBREL (1-888-436-2735).
  - If the autoinjector has been dropped, call for a replacement at 1-888-4ENBREL (1-888-436-2735).

Important: Keep the autoinjector, cartridge, and sharps disposal container out of the sight and reach of children.

AutoTouch® Reusable Autoinjector Storage and Handling

- Store the autoinjector at room temperature in a dry, safe place, such as a cabinet or drawer at 50°F to 104°F (10°C to 40°C).
- Do not store the autoinjector in the refrigerator with the cartridge.
- Use an alcohol wipe to clean the bottom (injection end) before and after each use.
  See the User Manual, section "Storage & Handling", for additional information.
  For more information or help, call 1-888-4ENBREL (1-888-436-2735).

Enbrel Mini® Cartridge Storage and Handling

- Keep the cartridge which contains ENBREL, in the refrigerator between 36°F to 46°F (2°C to 8°C).
- If needed, you may store the cartridge at room temperature between 68°F to 77°F (20°C to 25°C) for up to 30 days.
- Do not put the cartridge back in the refrigerator once it reaches room temperature.
- Record the date you removed the cartridge from the refrigerator and use it within 30 days.
- Do not store the cartridge in extreme heat or cold. For example, avoid storing in your vehicle's glove box or trunk.
- Do not freeze the cartridge.
- Do not shake the cartridge at any time.
- Keep the cartridge in the original carton to protect it from light or physical damage.
- Do not remove the purple needle cap from the cartridge until it is inside the autoinjector and you have reached step 11 in this Instructions for Use.

Important: Place the cartridge in a sharps disposal container if it has reached room temperature and has not been used within 30 days.

For more information or help call 1-888-4ENBREL (1-888-436-2735).

We're right here, right when you need us.

Personalized patient support designed for you.

AMGEN Support^+

With financial support resources and other helpful patient services, we are here to help you along the way.
Call 1-888-4ENBREL (1-888-436-2735) or visit enbrel.com/support to find out more.

Scan the QR code for more information

Additional Support

Scan the QR code for some helpful things to know as you get started.

ENBRELinjection.com

AMGEN

Manufactured by:
Amgen Inc.
One Amgen Center Drive
Thousand Oaks, California 91320-1799
U.S. License Number 1132

© 2025 Amgen Inc. All rights reserved.
Issued 12/2025
Version: 9

INSTRUCTIONS FOR USE

AutoTouch® reusable
autoinjector for use with
Enbrel Mini® (etanercept)
single-dose prefilled cartridge

User Manual

Table of Contents
Getting Started | 4
Reference Guide | 5
Resources | 6
Guide to Parts | 8
Troubleshooting: Error Symbols | 18
Troubleshooting: Common Problems | 24
Storage & Handling | 28
Cleaning Instructions | 30
Warnings | 31
Technical Information | 32
Symbol Table | 34

Getting Started

This User Manual contains helpful information about your AutoTouch® reusable autoinjector. It includes resources, care details, and a troubleshooting guide to save for ongoing reference.

To learn how to inject using AutoTouch, see your healthcare provider for injection training and use the Instructions for Use included in the carton.

Instructions for Use

A fold-out, step-by-step Instructions for Use is provided in the carton, which provides you with full instructions to learn how to give yourself a safe, successful and accurate injection.

Note: Please read the full Instructions for Use included in the carton.

The Reference Guide on the next page should only be used when you have successfully completed an injection using the Instructions for Use.

Reference Guide

Prepare and clean your injection site. |  | Hold the Enbrel Mini® single-dose prefilled cartridge with labeled side facing out and slide into door. Close door. Remove purple cap.
1 |  | 2
Place and hold on skin. Wait for the status button to turn green. |  | To start injection: Press and release the green status button. |  | Injection is finished when you hear a chime and all lights are turned off.
3 |  | 4 |  | 5

Resources

Personalized help from ENBREL Support™

Here are just a few of the benefits available at no cost to you:

- Live nurses online or on the phone seven days a week, 8 AM to 11 PM (ET)
- ENBREL Support copay card and other financial help
- Medication and refill reminders by phone or email
- Needle disposal containers through the Sharps Mail-Back Program

Sign up at 1-888-4ENBREL (1-888-436-2735) or EnbrelSupport.com.

Guide to Parts

AutoTouch® reusable autoinjector

Finger grip
When injecting, hold the AutoTouch® reusable autoinjector with fingers wrapped around the gray finger grip.

Door button

Press this button to open the door for insertion of the Enbrel Mini® single-dose prefilled cartridge. When your injection is finished, the door will open automatically.

Viewing window

During an injection, you can look through this window and see the plunger lowering to deliver your medicine. When AutoTouch is awake, the viewing window will light up. If Enbrel Mini is in AutoTouch, and the viewing window has no light, then press the status button to wake up AutoTouch.

You will open this door and insert Enbrel Mini into AutoTouch. The door will open automatically when your injection is finished. When inserted properly, Enbrel Mini will slide freely and completely into and out of the door.

Guide to Parts

AutoTouch® reusable autoinjector

Status button

Press this button to begin an injection. Lights will indicate the status of your injection.

Green:
Ready to press and start injection.

Blinking green:
The needle is inserting and your injection is in progress.

Red:
An error has occurred. See the Troubleshooting section of this manual.

Progress bar

These stacked green bars are fully lit when your injection starts, and the bar of lights decrease as your injection is in progress. The lights will disappear when your injection is finished.

Speed switch

The AutoTouch® reusable autoinjector allows you to choose from three injection speeds. The pre-set speed is medium.
(+) is faster
(•) is medium
(–) is slower

Guide to Parts

AutoTouch® reusable autoinjector

Sound switch

Sounds can be turned off and on. (Sounds on) Slide switch down. (Sounds off) Slide switch up so that the red bar is visible.

Note: Error sounds will still be heard if the sounds have been turned off.

Injection end

The entire injection end must be touching your skin during injections. This is also where the needle will come out.

Skin sensor

A skin sensor is located on the injection end. When the injection end is placed on skin the start button light will turn green. Hold the injection end flat and steady on your skin throughout the entire injection process.

Site light

When the Enbrel Mini® single-dose prefilled cartridge is loaded and the purple cap is removed, the injection end will light up to help you see your injection site.

Guide to Parts

Enbrel Mini® single-dose prefilled cartridge

Labeled side

When inserting the Enbrel Mini® cartridge make certain that the labeled side is facing out. Then slide Enbrel Mini into the door. It will slide all the way down into the AutoTouch® reusable autoinjector.

Expiration date

Confirm expiration date printed on the label has not passed.

Enbrel Mini window

This is where you will look to examine your medicine before starting an injection. See Instructions for Use for more information.

Purple cap

The purple cap keeps your medicine safe. Do not remove the cap on Enbrel Mini before loading it into AutoTouch. Load Enbrel Mini with the purple cap on, and remove the cap only when you are ready to give yourself the injection. Do not leave the purple cap off for more than five minutes. This can dry out the medicine.

See the Instructions for Use for more detail about loading Enbrel Mini and when to remove the purple cap.

Guide to Parts

AutoTouch® reusable autoinjector

How it works.

When you push the status button to start an injection, the AutoTouch® reusable autoinjector pushes a hidden needle out of the Enbrel Mini® single-dose prefilled cartridge into your skin. Then, a plunger rod will push into Enbrel Mini, injecting medicine into your body. After the medicine is injected, the rod will pull back up and the needle will withdraw from your skin. After a successful injection all lights will turn off and the door will open. The needle stays hidden at all times during the injection process.

What you will hear.

Needle insertion and plunger rod are operated by motors. You will hear a motor noise as the rod moves down and then back up again. Whenever you hear a motorized noise, you will know that an injection is in progress.

What you will see.

During the injection, the viewing window light will be on, and the plunger rod will move through the window. Also during the injection, the status light will be flashing green, and the progress bar will decrease. After a successful injection, the progress bar, and status button will turn off, and AutoTouch will open the door.

If the status light turns red, and beeps for more than a few seconds, an error has occurred. Use the troubleshooting section of this manual to see what to do if this happens.

Troubleshooting: Error Symbols

Error Symbols

The AutoTouch® reusable autoinjector makes a chime sound, lights the status button red, and displays an error symbol if there is a problem.

See the following description of each error symbol, possible reasons for the error, and actions you can take.

Low battery

Symbol: Orange battery and error sound.
Problem: The battery is running very low. Less than three weeks or three injections remain. The battery has a life of two years or 130 injections from your first injection. The battery is not replaceable or rechargeable.
Action: Call 1-888-4ENBREL (1-888-436-2735) for a replacement AutoTouch reusable autoinjector.

Battery Dead

Symbol: Orange battery and red triangle with exclamation point, red status button, and error sound.
Problem: The AutoTouch® reusable autoinjector battery is dead.
Action: Call the 1-888-4ENBREL (1-888-436-2735) for a replacement AutoTouch reusable autoinjector.

Too hot or cold

Symbol: Orange sun and a snowflake, and an error sound.
Problem: AutoTouch is too hot or too cold. This will lock the door.
Action: Place AutoTouch at room temperature in a safe, dry place and allow it to naturally cool or warm to room temperature. Then try again. Store the AutoTouch reusable autoinjector in a dry, safe place, such as a cabinet or drawer at 50° F to 104° F (10° C to 40° C).

Troubleshooting: Error Symbols

Enbrel Mini problem

Symbol: Orange Enbrel Mini® single-dose prefilled cartridge with blinking red status button and error alert sound.
Problem: There are five possible reasons you are getting this error. Please read below.

Problem #1: The purple cap was removed before inserting Enbrel Mini.
Action: Wait for the error to clear and close the door without Enbrel Mini in, and try again with a new Enbrel Mini. Make sure to leave the purple cap on until Enbrel Mini has been placed inside the AutoTouch® reusable autoinjector and the door is closed. Call 1-888-4ENBREL (1-888-436-2735) for a replacement Enbrel Mini.

Problem #2: Sensor lost skin contact during injection.
Action: Hold the injection end of AutoTouch on your skin throughout the entire injection until the green status button turns off, even if the motor sounds stop. Lifting or shifting on your skin during injection may lead to an incomplete injection. Call your healthcare provider if you feel you have given yourself an incomplete injection.

Problem #3: Enbrel Mini® single-dose prefilled cartridge is defective or not recognized as an Amgen product.
Action: Remove Enbrel Mini. Replace with a new Enbrel Mini. Call 1-888-4ENBREL (1-888-436-2735) for a replacement Enbrel Mini.

Problem #4: Door is held closed for more than one minute.
Action: Remove your hand from the door. When the door opens, remove Enbrel Mini from AutoTouch®, if present. Wait for the error symbol to stop blinking and close the door. If you have not given yourself an injection, place a new Enbrel Mini in AutoTouch and continue. If the error symbol remains on, call 1-888-4ENBREL (1-888-436-2735).

Problem #5: AutoTouch has been dropped.
Action: A dropped AutoTouch is not safe to use. Call 1-888-4ENBREL (1-888-436-2735) for a replacement.

Troubleshooting: Error Symbols

Needle Exposure

Symbol: Orange Enbrel Mini® single-dose prefilled cartridge, a red triangle with an exclamation point, red status button, and error sound.
Problem: A problem occurred during an injection and the needle may be exposed.
Action: If there is still fluid in Enbrel Mini, an incomplete dose may have been injected. Call your healthcare provider if you feel you have given yourself an incomplete injection. Call 1-888-4ENBREL (1-888-436-2735) for further assistance with your AutoTouch®.

Use caution when both Enbrel Mini problem symbol and the AutoTouch® reusable autoinjector failure symbols are lit as the needle may be exposed. Take special care when removing and handling Enbrel Mini. Remove Enbrel Mini then put it in a FDA-cleared sharps disposal container.

AutoTouch® Reusable Autoinjector Failure

Symbol: Red triangle with an exclamation point, red status button, and error sound.
Problem: Several errors have occurred or AutoTouch has stopped working.
Action: Reset AutoTouch.

To reset AutoTouch:

Hold AutoTouch away from skin and press the status button to wake AutoTouch. The failure symbol should begin blinking and a chime should sound.

While the failure symbol is blinking, press and hold door button until all symbols are temporarily displayed and the status button blinks green. The door button should be held for at least 10 seconds. After a successful reset, if an Enbrel Mini® single-dose prefilled cartridge is still inside AutoTouch, remove it. Close the AutoTouch door. Then, for the next injection, start by pressing the door button to open Enbrel Mini door.

If AutoTouch does not respond after three attempts to reset, call 1-888-4ENBREL (1-888-436-2735).

Troubleshooting: Common Problems

Common Problems

Enbrel Mini® single-dose prefilled cartridge is difficult to insert into the door.

Never force Enbrel Mini into the door. When positioned correctly, it will fall freely and completely into and out of the door. If it is difficult to load, double check that you are holding Enbrel Mini as shown.

- Purple cap is facing down
- Label facing outwards (away from the handle)

Injection does not start when pressing the status button.

Reason #1: Place the AutoTouch® reusable autoinjector on your skin and wait for the status button to turn green. A skin sensor is located on the injection end. You cannot start an injection unless the injection end of AutoTouch is touching your skin. Hold the injection end on your skin throughout the entire injection.

Reason #2: AutoTouch may be asleep. To conserve battery power, AutoTouch goes into a “sleep mode” after three minutes of no activity. If it seems unresponsive/asleep, remove AutoTouch from your skin and press the status button to wake it up.

An Enbrel Mini error symbol appears immediately after loading the Enbrel Mini® single-dose prefilled cartridge.
Reason: This will happen if the purple cap has been removed before inserting Enbrel Mini into the door. Do not reuse or recap. Begin again using a new Enbrel Mini.
Do not remove the purple cap until after Enbrel Mini has been inserted into AutoTouch.

Troubleshooting: Common Problems

Injection aborts or an error symbol appears while the injection is in process.
The AutoTouch® reusable autoinjector will abort an injection if the sensor loses skin contact. Avoid adjusting or moving AutoTouch during an injection. Hold AutoTouch on your skin until the green status light turns off and the injection is finished. Shifting, repositioning or lifting from your skin during injection may lead to an incomplete dose.

AutoTouch door will not remain closed.
Reason #1: At the end of an injection, the door cannot be closed with a used Enbrel Mini® single-dose prefilled cartridge inside.
Reason #2: When AutoTouch experiences a failure, the door will open and remain open. If this occurs, call 1-888-4ENBREL (1-888-436-2735).

A chime is repeating but no error lights are showing.
If the door is left open for more than 45 seconds, a chime will sound. Close the door to silence the chime.

AutoTouch is not producing chiming sounds.
The sound setting may be off. Turn on by sliding the sound switch down.
Enbrel Mini® single-dose prefilled cartridge will not eject.
Reason #1: If the viewing window has no light, press the status button to wake up AutoTouch. Then press and hold the door button for at least two seconds to eject.
Reason #2: If Enbrel Mini does not eject automatically at the end of an injection, there may be a problem. Call 1-888-4ENBREL (1-888-436-2735).

The purple cap is very hard to remove.
The purple cap should not be removed outside of the AutoTouch® reusable autoinjector. It should be removed after it is loaded into AutoTouch, when you are ready to inject. If Enbrel Mini is loaded and the purple cap is difficult to remove, call 1-888-4ENBREL (1-888-436-2735).

The injection speed will not change during injection.
Once the injection starts, the speed cannot be changed. Always set the speed prior to injection.

The injection is faster or slower than expected.
The speed switch may have been moved unintentionally. Check the speed setting prior to starting each injection.

Storage & Handling

Storage
AutoTouch® reusable autoinjector

Do | Do Not
Do store AutoTouch in dry, safe place at room temperature such as a cabinet or drawer. | Do not store AutoTouch in the refrigerator with the Enbrel Mini® single-dose prefilled cartridges.
Do store AutoTouch in its carton when not in use. | Do not store AutoTouch in extreme heat or cold, or in highly humid environments like the bathroom.

Handling
AutoTouch reusable autoinjector

Do

Do Not

Do inspect AutoTouch for physical damage or defects before each use.

Do not use AutoTouch if it has been dropped on a hard surface.
Do not use AutoTouch if any part appears cracked or broken.

Do not leave AutoTouch door open for more than 45 seconds when not in use. (Chime will sound and AutoTouch will go to sleep).

Do not crush, burn, heat, or incinerate the battery as this may cause a risk of fire or explosion.

Do not use AutoTouch if it has been dropped on a hard surface. Call 1-888-4ENBREL
(1-888-436-2735) for a replacement.

Storage and Handling
Enbrel Mini® single-dose prefilled cartridge

Do | Do Not
Do store unused Enbrel Mini in the refrigerator. | Do not freeze the unused Enbrel Mini. Do not warm Enbrel Mini using a heat source such as hot water or a microwave.
Do make sure to hold Enbrel Mini with the labeled side facing out and slide into the door. | Do not force Enbrel Mini into the door. Do not use Enbrel Mini if it has been dropped on a hard surface.
Do put Enbrel Mini in the door before removing the purple cap. | Do not remove the purple cap before inserting into AutoTouch. Do not re-use or recap Enbrel Mini.
Do discard the purple cap immediately after removing to avoid a choking hazard. | Do not use Enbrel Mini if any part appears cracked or broken.

Cleaning Instructions

Cleaning
AutoTouch® reusable autoinjector

Do | Do Not
Do use an alcohol wipe to clean the injection end of AutoTouch before and after injections. | Do not clean AutoTouch with water.
Do use an alcohol wipe to clean all other areas of AutoTouch as desired. | Do not immerse AutoTouch in water.
 | Do not wipe AutoTouch with household cleanser or soap.

Warnings

No modification of the AutoTouch® reusable autoinjector is allowed.

No part of AutoTouch can be repaired or replaced, including the battery.

Do not put anything inside the door other than an Enbrel Mini® single-dose prefilled cartridge.

Do not immerse AutoTouch in water.

Do not reach inside AutoTouch.

Do not crush, burn or heat AutoTouch.

AutoTouch contains moving parts. Keep your fingers out of openings in the injection end or open door.

Keep AutoTouch and Enbrel Mini out of the reach of children.

If AutoTouch fails, the maximum amount of medicine you could receive is the contents of the full Enbrel Mini, which is the correct dose.

Use caution if an error occurs as the needle may be exposed.

Carefully dispose of Enbrel Mini in an FDA approved sharps container.

Call your healthcare provider if you have any concerns regarding an incomplete injection.

When travelling, keep AutoTouch with you, in your carry-on bags.

Do not dispose of AutoTouch in the household trash. Call 1-888-4ENBREL (1-888-436-2735) for a replacement.

Technical Information

International Protection Rating

The international protection code for the AutoTouch® reusable autoinjector when stored in its carton is IP52. Which means it is protected from limited dust ingress and from limited dripping water. AutoTouch is not rated for dust or fluid ingress when not stored in its carton.

Environmental Operating Range

AutoTouch will operate in the temperature range of 50° F to 104° F (10° C to 40° C), and 20% to 90% relative humidity, and at elevations from 197 feet below sea level to 11,483 feet above sea level (-60 m to 3500 m).

Environmental Storage Range

Transport and store AutoTouch in its carton, in a dry place at room temperature: 50° F to 104° F (10° C to 40° C). AutoTouch been tested to a brief exposure at -40° F to 158° F (-40° C to 70° C), 50% relative humidity, and pressure equivalent of 14000 ft (4267 m).

Electromagnetic Compatibility

Avoid operating AutoTouch near microwave ovens, wireless routers, baby monitors or other common household electronics that operate using RF transmission. Two meters (six feet) is a reasonable distance.

Avoid operating AutoTouch near high magnetic or other fields such as those around MRI, CAT, or PET scanners.

AutoTouch does not emit RF.

Electrical characteristics

The AutoTouch® reusable autoinjector uses a non-replaceable, non-rechargeable DL123 Lithium battery. The battery has a nominal voltage of 3.0 V with a capacity of 1400 mAh. The expected service life of AutoTouch is two years or 130 injections from the first injection.

AutoTouch has a Type BF applied part: it has a capacitive electrical sensor that is isolated by plastic from the skin.

Dimensions and weight

AutoTouch weighs 0.4 pounds (180 grams), and is 9 inches (228 mm) tall by 1.5 inches (38 mm) wide by 1.8 inches (45 mm) deep.

Biocompatibility and electrical isolation

The injection end of the reusable autoinjector is intended to come into contact with the skin (see Guide to parts). It is a Type BF applied part. This means that it is electrically isolated from the battery. The injection end and finger grip of AutoTouch are made of ABS plastic. This material has been biocompatibility-tested for skin sensitivity and irritation.

Symbol Table

Do not re-use

Use-by date
(Exp. date)

Lot number

Keep dry

Serial number

Type BF applied part
Injection end of device is a Type BF applied part.

CAUTION, consult accompanying documents

Refer to instructions for use

Do not use if package is damaged

This product contains dry natural rubber

AMGEN®

Manufactured by:
Immunex Corporation
Thousand Oaks, CA 91320-1799
©1998 – 2018 Immunex Corporation. All rights reserved.
[partnumber]
Revised: 12/2018 v5

AMGEN®

INSTRUCTIONS FOR USE

AutoTouch Connect®
reusable autoinjector for use with
Enbrel Mini® (etanercept)
single-dose prefilled cartridge

User Manual

Table of Contents
Getting Started | 4
Resources | 5
Guide to Parts | 6
Troubleshooting: Error Symbols | 16
Troubleshooting: Common Problems | 24
Storage & Handling | 30
Cleaning Instructions | 32
Warnings | 33
Technical Information | 34
Symbol Table | 41

Getting Started

This AutoTouch Connect® User Manual contains helpful information about your AutoTouch Connect reusable autoinjector. It includes resources, care details, and a troubleshooting guide to save for ongoing reference.

To learn how to inject using the autoinjector, see your healthcare provider for injection training and use the Instructions for Use included in the carton.

Instructions for Use

Step-by-step Instructions for Use are provided in the carton, which provides you with full instructions to learn how to give yourself a safe, successful, and accurate injection.

Note: Please read the full Instructions for Use included in the carton.

Resources

We're right here, right when you need us.

Personalized patient support designed for you.

AMGEN Support^+

With financial support resources and other helpful patient services, we are here to help you along the way.

Call 1-888-4ENBREL (1-888-436-2735) or visit enbrel.com/support to find out more.

Scan the QR code for more information

Additional support

Scan the QR code for some helpful things to know as you get started.

ENBRELinjection.com

Guide to Parts

AutoTouch Connect reusable autoinjector

Finger grip

When injecting, hold the autoinjector with fingers wrapped around the gray finger grip.

Door/Power on button

Press this button to power on and open the door for insertion of the cartridge. When your injection is finished, the door will open automatically.

Expiration date (Exp.)

Confirm expiration date printed on the autoinjector label has not passed. If the expiration date is within 1 month, call 1-888-4ENBREL (1-888-436-2735) for a replacement.

Viewing window

During an injection, you can look through this window and see the plunger lowering to deliver your medicine. When the autoinjector is awake, the viewing window will light up. If the cartridge is in the autoinjector, and the viewing window has no light, then press the status button to wake up the autoinjector.

Asleep
(light off)

Awake
(light on)

Door

You will open this door and insert the cartridge into the autoinjector. The door will open automatically when your injection is finished. When inserted properly, the cartridge will slide freely and completely into and out of the door.

Guide to Parts

AutoTouch Connect reusable autoinjector

Status button

Press this button to begin an injection. Lights will indicate the status of your injection.

Green:
Ready to press and start injection.

Flashing green:
The needle is inserted and your injection is in progress.

Red:
An error has occurred. See the Troubleshooting section of this manual.

Progress bar

These stacked green bars are fully lit when your injection starts, and the bar of lights decrease as your injection is in progress. The lights will disappear when your injection is finished.

Speed switch

The autoinjector allows you to choose from 3 injection speeds. The pre-set speed is medium (•).

(+) fast

(•) medium

(–) slow

Guide to Parts

AutoTouch Connect reusable autoinjector

Sound switch

Sounds can be turned off and on.

Note: Error sounds will still be heard if the sounds have been turned off.

Sounds on:
Slide switch down.

Sounds off:
Slide switch up so that the red bar is visible.

Injection end

The entire injection end must be touching your skin during injections. This is also where the needle will come out.

Skin sensor

A skin sensor is located on the injection end. When the injection end is placed on skin the status button light will turn green. Hold the injection end flat and steady on your skin throughout the entire injection process.

Site light

When the cartridge is loaded and the purple needle cap is removed, the injection end will light up to help you see your injection site. Do not remove the purple needle cap on the cartridge before loading it into the autoinjector.

Guide to Parts

Enbrel Mini single-dose prefilled cartridge

Enbrel Mini window

This is where you will look to examine your medicine before starting an injection. See Instructions for Use for more information.

Expiration date

Confirm expiration date printed on the cartridge label has not passed.

Labeled side

When inserting the cartridge make certain that the labeled side is facing out. Then slide the cartridge into the door. It will slide all the way down into the autoinjector.

Purple needle cap

The purple needle cap keeps your medicine safe. Do not remove the purple needle cap on the cartridge before loading it into the autoinjector. Load the cartridge with the purple needle cap on, and remove the cap only when you are ready to give yourself the injection. Do not leave the purple needle cap off for more than 5 minutes. This can dry out the medicine.

See the Instructions for Use for more details about loading the cartridge and when to remove the purple needle cap.

Guide to Parts

AutoTouch Connect reusable autoinjector

How it works.

When you push the status button to start an injection, the autoinjector pushes a hidden needle out of the cartridge into your skin. Then, a plunger rod will push into the cartridge, injecting medicine into your body. After the medicine is injected, the rod will pull back up and the needle will withdraw from your skin. After a successful injection all lights will turn off and the door will open. The needle stays hidden at all times during the injection process.

What you will hear.

Needle insertion and plunger rod are operated by motors. You will hear a motor noise as the rod moves down and then back up again. Whenever you hear a motorized noise, you will know that an injection is in progress.

What you will see.

During the injection, the viewing window light will be on, and the plunger rod will move through the window. Also during the injection, the status light will be flashing green, and the progress bar will decrease. After a successful injection, the progress bar, and status button will turn off, and the autoinjector will open the door.

If the status light turns red, and beeps for more than a few seconds, an error has occurred. Use the Troubleshooting section of this manual to see what to do if this happens.

Troubleshooting:
Error Symbols

Error Symbols

If an error occurs with your autoinjector, you will hear an error sound, the status button will flash red, and an error symbol will be displayed.

See the following description of each error symbol, possible reasons for the error, and actions you can take.

Low battery
See page 18

Needle exposure
See page 18

Battery dead
See page 19

Too hot or too cold
See page 19

Enbrel Mini problem
See page 20-21

Autoinjector detected problem
See page 22-23

Low battery

Symbol: Red battery, solid red status button, and error sound.

Problem: The battery is running very low. Less than 3 weeks or 3 injections remain.

Action: Call 1-888-4ENBREL (1-888-436-2735) for a replacement autoinjector.

Note: Your autoinjector can continue to be used for up to 3 weeks or 3 injections. The battery is not replaceable or rechargeable.

Needle exposure

Symbol: Orange cartridge, red triangle with exclamation point, flashing red status button, and error sound.

Problem: A problem occurred during an injection and the needle may be exposed.

Action: Reset the autoinjector, see "Reset instructions" on page 23.

If there is still fluid in the cartridge, an incomplete dose may have been injected. Call your healthcare provider if you feel you have given yourself an incomplete injection.
Call 1-888-4ENBREL (1-888-436-2735) for further assistance with your autoinjector.

Use caution when both the "Enbrel Mini problem" symbol and the "Autoinjector detected problem" symbols are lit as the needle may be exposed. Take special care when removing and handling the cartridge. Remove the cartridge and put in an FDA-cleared sharps disposal container.

Battery dead

Symbol: Red battery, red triangle with exclamation point, flashing red status button, and error sound.

Problem: The autoinjector battery is dead.

Action: Call 1-888-4ENBREL (1-888-436-2735) for a replacement autoinjector.

Too hot or too cold

Symbol: Orange sun, snowflake, flashing red status button, and error sound.

Problem: The autoinjector is too hot or too cold. This will lock the door.

Action: Place the autoinjector at room temperature in a dry, safe place and allow it to naturally cool or warm to room temperature. Then try again.

Store the autoinjector in a dry, safe place, such as a cabinet or drawer at 50°F to 104°F (10°C to 40°C). Do not store the autoinjector in the refrigerator.

Enbrel Mini problem

Symbol: Orange cartridge, flashing red status button, and error sound.

There are 5 main reasons this error may happen. See list below:

Problem #1: The purple needle cap was removed from the cartridge before inserting into the autoinjector.

Action: Wait 2 minutes for the error to clear. Remove the cartridge. Close the door without the cartridge inserted. Start over with a new cartridge.

Make sure to leave the purple needle cap on until the cartridge has been placed inside the autoinjector and the door is closed.

Call 1-888-4ENBREL (1-888-436-2735) for a replacement cartridge and instructions on what to do with the uncapped cartridge.

- OR -

Problem #2: The autoinjector was lifted from the skin before the injection was complete.

Action: Hold the autoinjector flat and steady on your skin throughout the entire injection until the green status button turns off, even if the motor sounds stop.

Lifting or shifting on your skin during the injection may lead to an incomplete injection. Call your healthcare provider if you feel you have given yourself an incomplete injection.

- OR –

Problem #3: The cartridge is defective or is not recognized as an Amgen product.

Action: Remove the cartridge. Start over with a new cartridge.

Call 1-888-4ENBREL (1-888-436-2735) for a replacement cartridge and instructions on what to do with the defective cartridge.

- OR -

Problem #4: Door is held closed for more than 1 minute.

Action: Remove your hand from the door, and the door will open automatically. When the door opens, remove the cartridge (if one is present). Wait for the error symbol to stop flashing, then close the door.

If you have not given yourself an injection, start over with a new cartridge. If the error symbol remains on, call 1-888-4ENBREL (1-888-436-2735).

- OR -

Problem #5: Autoinjector has been dropped.

Action: A dropped autoinjector is not safe to use. Call 1-888-4ENBREL (1-888-436-2735) for a replacement.

Autoinjector detected problem

Symbol: Red triangle with an exclamation point, flashing red status button, and error sound.

Problem: Several errors have occurred or the autoinjector has stopped working.

Action: Reset the autoinjector by following the steps below.

Reset instructions:

1. Hold the autoinjector away from the skin.
2. Press and release the status button.
3. Press and hold the door button until the status button flashes green. This will take 10-15 seconds.

The autoinjector is reset and ready to use when:

- all error symbols are displayed, and
- the status button flashes green.

4. After a successful reset, if the cartridge is still inside the autoinjector, remove it. Close the autoinjector door.

If the autoinjector does not respond after 3 attempts to reset, call 1-888-4ENBREL (1-888-436-2735).

Troubleshooting:
Common Problems

Common Problems

See the following description of common problems, possible causes, and actions you can take. If you are unable to resolve your issue, please call 1-888-4ENBREL (1-888-436-2735) for additional support.

- Cartridge is difficult to insert into the door. See page 25
- Injection does not start when pressing the status button. See page 26
- The status light will not turn green when placed on skin. See page 26
- An error symbol appears immediately after loading the cartridge. See page 26
- Injection aborts and an error symbol appears while the injection is in process. See page 27
- Autoinjector door will not remain closed. See page 27
- A chime is repeating but no error lights are showing. See page 28
- Autoinjector is not producing chiming sounds. See page 28
- The cartridge will not eject. See page 28
- The purple needle cap is very hard to remove. See page 29
- The injection speed will not change during the injection. See page 29
- The injection is faster or slower than expected. See page 29

Cartridge is difficult to insert into the door.

Problem: The cartridge is not positioned correctly to insert into the autoinjector.

Action: Do not force the cartridge into the door. Insert the cartridge with the purple needle cap down and the labeled side facing out. The cartridge will slide all the way down into the autoinjector.

If the cartridge is difficult to insert, double check that the:

- purple needle cap is down, and
- labeled side is facing out.

Injection does not start when pressing the status button.

Problem: The autoinjector is not in full contact with your skin.

Action: Place the autoinjector with the entire injection end flat against your skin and wait for the status button to turn green.

A skin sensor is located on the injection end. You cannot start an injection unless the injection end of the autoinjector is touching your skin. Hold the injection end on your skin throughout the entire injection.

The status light will not turn green when placed on skin.

Problem: The autoinjector may be asleep.

Action: If the autoinjector seems unresponsive, or the viewing window has no light, remove the autoinjector from your skin and press the status button to wake it up.

Note: To conserve battery power, the autoinjector goes into a "sleep mode" after 3 minutes of no activity.

An error symbol appears immediately after loading the cartridge.

Problem: The purple needle cap has been removed before inserting the cartridge into the autoinjector.

Action: Do not reuse or recap the cartridge. Start over with a new cartridge.

Do not remove the purple needle cap until after the cartridge has been inserted into the autoinjector. Only remove the purple needle cap when you can inject right away (within 5 minutes) as the medicine can dry out.

Injection aborts and an error symbol appears while the injection is in process.

Problem: The autoinjector will abort an injection if the skin sensor loses skin contact.

Action: Avoid adjusting or moving the autoinjector during an injection. Hold the autoinjector flat and steady on your skin until the green status light turns off and the injection is finished. Shifting, repositioning, or lifting from your skin during injection may lead to an incomplete dose.

Autoinjector door will not remain closed.

Problem#1: At the end of an injection, the door cannot be closed with a used cartridge inside.

Action: Remove the cartridge and close the door.

- OR -

Problem#2: When the autoinjector experiences a failure, the door will open and remain open.

Action: See "Reset instructions" on page 23 to reset the autoinjector or call 1-888-4ENBREL (1-888-436-2735).

A chime is repeating but no error lights are showing.

Problem: If the door is left open for more than 45 seconds, a chime will sound.

Action: Close the door to silence the chime.

The autoinjector is not producing chiming sounds.

Problem: The sound setting may be turned off.

Action: Turn on by sliding the sound switch down (see page 11).

The cartridge will not eject.

Problem#1: The autoinjector is asleep.

Action: If the viewing window has no light, press the status button to wake up the autoinjector. Then press and hold the door button for at least 2 seconds to eject.

- OR -

Problem#2: The cartridge does not eject automatically at the end of an injection.

Action: Call 1-888-4ENBREL (1-888-436-2735).

The purple needle cap is very hard to remove.

Problem: The purple needle cap should only be removed after the cartridge is loaded into the autoinjector and you are ready to inject.

Do not remove the purple needle cap until after the cartridge has been inserted into the autoinjector. Do not leave the purple needle cap off for more than 5 minutes. This can dry out the medicine.

Action: If the cartridge is loaded and the purple needle cap is difficult to remove, call 1-888-4ENBREL (1-888-436-2735).

The injection speed will not change during the injection.

Problem: Once the injection starts, the speed cannot be changed.

Action: Always set the speed prior to injection (see page 9).

The injection is faster or slower than expected.

Problem: The speed switch may have been moved unintentionally.

Action: Check the speed setting prior to starting each injection (see page 9).

Storage & Handling

Storage: Autoinjector

Do | Do Not
Do store the autoinjector in dry, safe place at room temperature such as a cabinet or drawer. | Do not store the autoinjector in the refrigerator with the cartridges.
Do store the autoinjector in its carton when not in use. | Do not store the autoinjector in extreme heat or cold, or in highly humid environments like the bathroom.

Handling: Autoinjector

Do | Do Not
Do inspect the autoinjector for physical damage or defects before each use. | Do not use the autoinjector if it has been dropped on a hard surface. Call 1-888-4ENBREL (1-888-436-2735) for a replacement.
Do inspect the autoinjector for physical damage or defects before each use. | Do not use the autoinjector if any part appears cracked or broken.
Do inspect the autoinjector for physical damage or defects before each use. | Do not leave the autoinjector door open for more than 45 seconds when not in use. (Chime will sound and the autoinjector will go to sleep).
Do inspect the autoinjector for physical damage or defects before each use. | Do not crush, burn, heat, or incinerate the battery as this may cause a risk of fire or explosion.

Storage and Handling: Cartridge

Do | Do Not
Do store unused cartridges in the refrigerator. | Do not freeze the unused cartridges. Do not warm the cartridges using a heat source such as hot water or a microwave.
Do make sure to hold the cartridge with the labeled side facing out and slide into the door. | Do not force the cartridge into the door. Do not use the cartridge if it has been dropped on a hard surface.
Do put the cartridge in the door before removing the purple needle cap. | Do not remove the purple needle cap before inserting into the autoinjector. Do not re-use or recap the cartridge.
Do discard the purple cap immediately after removing to avoid a choking hazard. | Do not use the cartridge if any part appears cracked or broken.

Cleaning Instructions

Cleaning: Autoinjector

Do | Do Not
Do use an alcohol wipe to clean the injection end of the autoinjector before and after injections. | Do not clean the autoinjector with water.
Do use an alcohol wipe to clean all other areas of the autoinjector as desired. | Do not immerse the autoinjector in water.
Do use an alcohol wipe to clean all other areas of the autoinjector as desired. | Do not wipe the autoinjector with household cleanser or soap.

Warnings

- No modification of the autoinjector is allowed.
- No part of the autoinjector can be repaired or replaced, including the battery.
- Do not put anything inside the door other than the cartridge.
- Do not immerse the autoinjector in water.
- Do not reach inside the autoinjector.
- Do not crush, burn, or heat the autoinjector.
- The autoinjector contains moving parts. Keep your fingers out of openings in the injection end or door.
- Keep the autoinjector and cartridge out of the reach of children.
- If the autoinjector fails, the maximum amount of medicine you could receive is the contents of the full cartridge, which is the correct dose.
- Use caution if an error occurs as the needle may be exposed.
- Carefully dispose of the cartridge in an FDA-cleared sharps disposal container.
- Call your healthcare provider if you have any concerns regarding an incomplete injection.
- When travelling, keep the autoinjector with you, in your carry-on bags.
- Do not dispose of the autoinjector in the household trash. Call 1-888-4ENBREL (1-888-436-2735) for a replacement.

Technical Information

This AutoTouch Connect® reusable autoinjector has a Bluetooth® wireless feature, which is designed to communicate wirelessly with an application on your mobile device to help you track your injections.

Currently, there is no mobile application available for use with this wireless feature. This wireless feature will not affect your injection steps.

You can inject without using the wireless feature. Always follow all steps found in the Instructions for Use.

Important Information Required by the Federal Communications Commission (FCC)

FCCID: 2AGZ4–ATCONNECT

The AutoTouch Connect® reusable autoinjector contains a Bluetooth® wireless feature.

AutoTouch Connect complies with Part 15 of the FCC Rules.

Operation is subject to the following two conditions:

1. AutoTouch Connect may not cause harmful interference.
2. AutoTouch Connect must accept any interference received, including interference that may cause undesirable operation.

Modification to AutoTouch Connect shall not be made without the written consent of Amgen.

Unauthorized modification may void the authority granted under FCC rules permitting the operation of AutoTouch Connect.

AutoTouch Connect has been tested and found to comply with the limits for a Class B digital device, pursuant to part 15 of the FCC Rules. These limits are designed to provide reasonable protection against harmful interference in a residential installation. AutoTouch Connect generates, uses, and can radiate radio frequency energy and, if not installed and used in accordance with the instructions, may cause harmful interference to radio communications. However, there is no guarantee that interference will not occur in a particular installation.

If AutoTouch Connect® does cause harmful interference to radio or television reception, which can be determined by moving AutoTouch Connect far away and back, the user is encouraged to try to correct the interference by one or more of the following measures:

- Reorient or relocate the receiving antenna.
- Increase the separation between AutoTouch Connect and interference receiver.
- Consult the dealer or an experienced radio/TV technician for help.

The Bluetooth® word mark and logos are registered trademarks owned by Bluetooth Special Interest Group (SIG) Inc. and any use of such marks by Amgen is under license. Other trademarks and trade names are those of their respective owners.

Technical Information

International Protection Rating

The international protection code for the AutoTouch Connect® reusable autoinjector when stored in its carton is IP52. Which means it is protected from limited dust ingress and from limited dripping water. AutoTouch Connect is not rated for dust or fluid ingress when not stored in its carton.

Environmental Operating Range

AutoTouch Connect will operate in the temperature range of 50°F to 104°F (10°C to 40°C), and 20% to 90% relative humidity, and at elevations from 197 feet below sea level to 11,483 feet above sea level (-60 m to 3500 m).

Environmental Storage Range

Transport and store AutoTouch Connect in its carton, in a dry place at room temperature: 50°F to 104°F (10°C to 40°C). AutoTouch Connect has been tested to a brief exposure at −40°F to 158°F (-40°C to 70°C), 50% relative humidity, and pressure equivalent of 14,000 feet (4267 m).

Bluetooth® Characteristics

The Bluetooth technology in the AutoTouch Connect complies with the Bluetooth Core Specification v5.0 and is qualified by Bluetooth SIG. The AutoTouch Connect has been designed to transmit default 0dBm standard industrial, scientific and medical (ISM) 2.4GHz band radio frequency (RF) and covers up to 10 meters communication range.

Quality of Service and Security Information

The AutoTouch Connect autoinjector has a Bluetooth wireless feature to establish an authenticated and encrypted connection with a Bluetooth capable device (e.g. mobile application). Initial setup requires physical access to the autoinjector labeled serial number for user input at initial pairing/secure bonding. There is no mobile application currently available.

Data is transferred from the autoinjector on a one-to-one paired mobile device for ensuring data integrity and quality of service (QoS). Data transferred is read-only and no patient information is stored on the autoinjector.

Data can be sent at any time, and temporary loss of proper QoS will be resolved upon resumed connection to the app. If connection with the app drops and re-establishes, data transfer resumes with data integrity verification. Data transfer latency or asynchronization does not affect drug delivery tracking as data will be confirmed upon reconnection.

Electromagnetic Compatibility

Portable and mobile RF communications equipment can affect medical electrical equipment. Avoid operating AutoTouch Connect near microwave ovens, wireless routers, baby monitors or other common household electronics that operate using RF transmission, including RFID emitters. A minimum distance of 30 cm (12 inches) is recommended.

Avoid operating AutoTouch Connect near high magnetic or other fields such as those around MRI, CAT, or PET scanners.

AutoTouch Connect emits RF.

Technical Information

Electromagnetic Emissions

The autoinjector is intended for use in the electromagnetic environment specified below. The user of the autoinjector should ensure that it is used in such an environment.
Emissions Test | Compliance | Electromagnetic Environment - Guidance
RF Emissions (CISPR 11) | Group 1 | The autoinjector uses RF energy for its internal and system interface functions. Its RF emissions are very low and are not likely to cause any interference in nearby electronic equipment.
RF Emissions (CISPR 11) | Class B | The autoinjector is suitable for use in all establishments, including domestic establishments and those directly connected to the public low-voltage power supply network that supplies buildings used for domestic purposes.
Harmonic emissions IEC 61000-3-2 | Not Applicable | The autoinjector is suitable for use in all establishments, including domestic establishments and those directly connected to the public low-voltage power supply network that supplies buildings used for domestic purposes.
Voltage fluctuations/flicker emissions IEC 61000-3-3 | Not Applicable | The autoinjector is suitable for use in all establishments, including domestic establishments and those directly connected to the public low-voltage power supply network that supplies buildings used for domestic purposes.

Electromagnetic Immunity

The autoinjector is intended for use in the electromagnetic environment specified below.
The user of this autoinjector should ensure that it is used in such an environment.
Immunity Test | IEC 60601 Test Level | Compliance Level | Electromagnetic Environment-Guidance
Electrostatic Discharge (ESD) IEC 61000-4-2 | ±8 kV Contact ±15 kV Air | ±15 kV Contact ±20 kV Air | Floors should be wood, concrete or ceramic tile. If floors are synthetic, the relative humidity should be at least 30%.
Power Frequency 50/60 Hz Magnetic Fields IEC 61000-4-8 | 30 A/m | 30 A/m at 60 Hz | Power frequency magnetic fields should be that of typical commercial or hospital environment.
RF Electro- magnetic Field IEC 61000-4-3 | 10 V/m 80 MHz – 2.5 GHz | (E1) = 10 V/m 26 MHz – 2.7 GHz | Portable and mobile RF communications equipment should be separated from the device by no less than the distances of 30 cm.

Technical Information

Electrical characteristics

The AutoTouch Connect® reusable autoinjector uses a non-replaceable, non-rechargeable DL123 Lithium battery. The battery has a nominal voltage of 3.0 V with a capacity of 1400 mAh.

The autoinjector enclosure is a Type BF applied part:

The skin sensor and other electronics are isolated from the skin.

Dimensions and weight

AutoTouch Connect weighs 0.4 pounds (180 grams), and is 9 inches (228 mm) tall by 1.5 inches (38 mm) wide by 1.8 inches (45 mm) deep.

Biocompatibility and electrical isolation

The autoinjector enclosure is intended to come into contact with the skin (see Guide to Parts). It is a Type BF applied part. This means that it is electrically isolated from the battery. The injection end and finger grip of AutoTouch Connect® are made of ABS plastic. This material has been biocompatibility-tested for skin sensitivity and irritation.

Contraindications

This device is contraindicated for use in a Magnetic Resonance (MR) environment. For contraindications of ENBREL® please refer to ENBREL prescribing information.

Symbol Table

Do not re-use

Use-by date (Exp. date)

Lot number

Keep dry

Serial number

Type BF applied part
The autoinjector enclosure is a Type BF applied part.

CAUTION, consult accompanying documents

Refer to instructions for use

Do not use if package is damaged

Magnetic Resonance (MR) Unsafe

AMGEN

Manufactured by:
Immunex Corporation
Thousand Oaks, CA 91320-1799
©2025 Immunex Corporation.
All rights reserved.
Revised: 12/2025 v5

This printed material is recyclable.

Instructions for Use Enbrel® (en-brel) (etanercept) injection, for subcutaneous use single-dose vial

Read this Instructions for Use before you start taking Enbrel and each time you get a refill. There may be new information. This information does not take the place of talking to your healthcare provider about your medical condition and treatment.

Step 1: Set up

1a. Strength and dose

The strength of the Enbrel single-dose vial is different than the Enbrel multiple-dose vial.

Each single-dose vial contains 25 mg (0.5 mL).

Review your prescription carefully for dose and dosing schedule. Only inject Enbrel after you or your caregiver has received training by your healthcare provider. Your healthcare provider will tell you how often you should use Enbrel. Do not use Enbrel more often than directed by your healthcare provider. If you forget to use Enbrel, inject your dose right away. Inject your next dose at your regular scheduled time. If you do not know when to inject Enbrel, call your healthcare provider or pharmacist.

Keep Enbrel out of the reach of children.

1b. Store Enbrel single-dose vials

Store Enbrel in the refrigerator between 36°F to 46°F (2°C to 8°C). You may also store the Enbrel single-dose vials at room temperature between 68°F to 77°F (20°C to 25°C) for up to 30 days. Throw away Enbrel that has been stored at room temperature after 30 days.

Do not shake.

Do not freeze or store in extreme heat or cold.

Store Enbrel in the original carton to protect from light or damage.

If your dose is 0.5 mL, or LESS

Remove 1 single-dose vial

If your dose is MORE than 0.5 mL

Remove 2 single-dose vials

1c. Remove correct number of vials

Remove the correct number of Enbrel single-dose vials from the original carton.

Check your prescription to determine if your dose will require 1 or 2 single-dose vials.

Your dose is determined in milliliters (mL).

Your child's dose of Enbrel depends on his or her weight. Your child's healthcare provider will tell you which form of Enbrel to use and how much to give your child.

Green vial cap WAIT

1d. Inspect the single-dose vial(s)

Leave the single-dose vial(s) at room temperature, with the green cap(s) on, for at least 30 minutes.

Enbrel is clear and colorless. There may be small white particles in the solution. Check the expiration date.

Keep out of direct sunlight.

Do not use Enbrel if:

- the expiration date has passed
- the green cap is not attached
- it has lumps, is discolored, or is cloudy.

If there are any issues with your Enbrel single-dose vials, please call 1-888-4ENBREL (1-888-436-2735).

1e. Gather all materials and wash hands

Wash your hands with soap and water.

Place the following items on a clean well-lit, flat surface:

- 1 mL syringe
- Long needle: for withdrawal
- Short needle: for injection
- Alcohol wipes
- Cotton balls
- Bandage
- Sharps disposal container

1f. Pop off the green vial cap then wipe the gray stopper

Use an alcohol wipe to clean the gray stopper.

If you require a second single-dose vial, clean the gray stopper of the second single-dose vial with a new alcohol wipe.

1g. Attach the long needle to the syringe

Twist the long needle onto the syringe.

Step 2: Prepare dose

2a. Pull plunger back, insert needle, and push air into single-dose vial

Pull the needle cap straight off and away from your body. Save the needle cap for later.

Pull the syringe plunger back to 0.5 mL.

Hold the single-dose vial on a flat surface with 1 hand. Insert the long needle through the gray rubber stopper above the medicine in the single-dose vial.

Slowly push 0.5 mL of air into the single-dose vial.

2b. Tilt the single-dose vial to withdraw all medicine

Slowly pull back the plunger to fill the syringe with all the medicine from the single-dose vial.

Remove needle from the single-dose vial.

The air in the syringe will be removed later.

2c. Gently tap the syringe with fingers to release bubbles

Gently tap the syringe with your fingers to release air pockets and bubbles until they rise to the top of the syringe.

2d. Push out large air pockets and bubbles

After you have gently tapped the large air pockets and bubbles to the top of the syringe, push the plunger up to remove the air out of the syringe.

Small amounts of tiny air bubbles are ok.

If you need 1 single-dose vial, push the plunger to your total prescribed dose and continue to step 2g.

If you need more than 1 single-dose vial to get your total prescribed dose, follow these 2 steps:

2e. Insert the same needle in the second vial
Tilt vial to withdraw medicine. Slowly pull back
the plunger to fill the syringe with all medicine
from the vial.
Remove the needle from the single-dose vial.
The air will be removed in the next step

2f. Gently tap the syringe to remove the air
Hold the needle pointing up and gently tap the syringe so air bubbles rise to the top.
Push the plunger to your prescribed dose.
Small amounts of tiny air bubbles are ok.

2g. Use 1-handed scoop method to recap
For your safety, place the needle cap on a flat surface.

Using 1 hand, slide the needle into the cap and scoop upwards to cap the needle, without using your other hand.

Then use your other hand to secure the cap and snap into place.

Step 3: Inject and throw away

3a. Replace the long needle with the short needle

Twist the long needle off of the syringe.

Throw away the long needle in the sharps disposal container.

Twist the short needle onto the syringe.

Do not remove the needle cover until you are ready to inject.

3b. Choose and clean the injection site

- thigh or stomach (avoid 2 inches around the navel)
- back of upper arm (only if someone else is giving the injection)

Choose a different site each time you give yourself an injection. Avoid injecting into tender, raised, red or scaly skin.

Clean the injection site with an alcohol wipe and let dry. Do not touch this area again before injecting.

3c. Pinch and inject Enbrel

Gently pinch skin. With a quick firm action, insert the needle into your skin at a 45-degree angle.

When the needle is completely inserted into the skin, slowly push the plunger all the way down.

When the syringe is empty, remove the needle and syringe from your skin. Do not recap the needle.

Do not rub the injection site. If you see drops of blood at the injection site, you can press a cotton ball over the injection site until bleeding has stopped. Apply an adhesive bandage, if needed.

3d. Throw away the used single-dose vials, needles and syringe

Single-dose vials do not contain preservatives and are for 1-time use only. Unused medicine in the single-dose vials must be thrown away in a sharps disposal container.

Additional disposal information

Do not throw away the vials, needles, and syringe in your household trash.

If you do not have a FDA-cleared sharps disposal container, you may use a household container that is:

- made of a heavy-duty plastic
- can be closed with a tight-fitting, puncture-resistant lid without sharps being able to come out
- upright and stable during use
- leak-resistant
- properly labeled to warn of hazardous waste inside the container

When your sharps disposal container is almost full, you will need to follow your community guidelines for the right way to throw away your sharps disposal container. There may be state or local laws about how you should throw away used vials, needles and syringes.

For more information about safe sharps disposal, and for specific information about sharps disposal in the state that you live in, go to the FDA's website at: http://www.fda.gov/safesharpsdisposal

- Do not throw away your used sharps disposal container in your household trash unless your community guidelines permit this. Do not recycle your used sharps disposal container.
- Do not reuse the vials, syringe, or needles.
- Do not recycle the vials, syringe, needles, or sharps disposal container or throw them into household trash.

Important: Always keep the sharps disposal container out of the reach of children.

If you experience any difficulty using your Enbrel single-dose vials, please call 1-888-4ENBREL (1-888-436-2735).

If you have any questions about your Enbrel dosing, please call your healthcare provider.

This Instructions for Use has been approved by the U.S. Food and Drug Administration.

AMGEN

Manufactured by:
Immunex Corporation
Thousand Oaks, CA 91320-1799
U.S. License Number 1132
© 1998-2020, 2022, 2024 Immunex Corporation. All rights reserved.
[part number]
Revised: 10/2024 v3

This printed material is recyclable.

Front Panel

Read these instructions before using Enbrel®
Single-Dose Vial
Instructions for Use

REFERENCE GUIDE

Side
1

Reference Guide
Enbrel® [en-brel]
(etanercept)
injection, for subcutaneous use
50 mg/mL

Read Instructions for Use in carton before injecting
Questions?
Call 1-888-4ENBREL
(1-888-436-2735)

1. Guide to parts

2. Wait 30 minutes
for the autoinjector to reach room temperature before giving your injection.

3. Prepare and clean your injection site.

4. Pull the white cap straight off when you are ready to inject within 5 minutes – the medicine can dry out.

Turn over to continue

Side 2 | Reference Guide Enbrel® [en-brel] (etanercept) injection, for subcutaneous use 50 mg/mL | AMGEN | Read other side first
Side 2 | Reference Guide Enbrel® [en-brel] (etanercept) injection, for subcutaneous use 50 mg/mL | Manufactured by: Immunex Corporation Thousand Oaks, CA 91320 © 1998-2016, 2019-2025 Immunex Corporation All rights reserved. XXXXXXX | This printed material is recyclable.

5. Stretch or pinch the skin to create a firm surface at the injection site until the injection is finished.

6. PUSH and HOLD down against the skin. Do not lift.

7. PRESS purple start button.

8. Keep pushing down for up to 15 seconds.
Wait for the window to turn fully yellow, then your injection is done.

Revised: 6/2025
v11

PRINCIPAL DISPLAY PANEL - 25 mg/0.5 mL Syringe Carton

Contains 4 Single-Dose Prefilled Syringes

NDC 58406-010-04

Enbrel®
etanercept

25
mg/0.5 mL

Not made with
natural rubber latex

25 mg/0.5 mL
Single-Dose Prefilled Syringe

Attention: Not for use in pediatric patients under 31 kg (68 pounds).
For Subcutaneous Use Only
Sterile Solution – No Preservative
Refrigerate at 2° to 8°C (36° to 46°F). DO NOT FREEZE.

Each single-dose prefilled syringe contains 0.5 mL of a clear and
colorless solution containing 25 mg/0.5 mL etanercept and is formulated at
pH 6.3 ± 0.2, with 25 mM L-arginine hydrochloride, 120 mM sodium chloride,
and 1% sucrose.

Specific activity: approximately 1.7 x 10^6 U/mg.

Manufactured by Immunex Corporation, Thousand Oaks, CA 91320
U.S. License No. 1132

©2013, 2017, 2022-2023 Immunex Corporation
Patent: http://pat.amgen.com/enbrel/

This carton is recyclable.

PRINCIPAL DISPLAY PANEL - 50 mg/mL Syringe Carton

Contains 4 Single-Dose Prefilled Syringes

NDC 58406-021-04

Enbrel®
etanercept

50
mg/mL

Not made with
natural rubber latex

50 mg/mL
Single-Dose Prefilled Syringe

Attention: Not for use in pediatric patients under 63 kg (138 pounds).
For Subcutaneous Use Only
Sterile Solution – No Preservative
Refrigerate at 2° to 8°C (36° to 46°F). DO NOT FREEZE.

Each single-dose prefilled syringe contains 1 mL of a clear and
colorless solution containing 50 mg/mL etanercept and is formulated at
pH 6.3 ± 0.2, with 25 mM L-arginine hydrochloride, 120 mM sodium chloride,
and 1% sucrose.

Specific activity: approximately 1.7 x 10^6 U/mg.

Manufactured by Immunex Corporation, Thousand Oaks, CA 91320
U.S. License No. 1132

©2013, 2017, 2022-2023 Immunex Corporation
Patent: http://pat.amgen.com/enbrel/

This carton is recyclable.

PRINCIPAL DISPLAY PANEL - 50 mg/mL Autoinjector Carton - 032-04

4 x Single-Dose Prefilled Autoinjectors

NDC 58406-032-04

Enbrel®
etanercept

50
mg/mL

50 mg/mL
Single-dose Prefilled Autoinjector

Attention: Not for use in pediatric patients under 63 kg
(138 pounds)

For Subcutaneous Use Only

Sterile Solution - No Preservative
Refrigerate at 36°F to 46°F (2°C to 8°C). DO NOT FREEZE.

ATTENTION: Enclosed Medication Guide is required for each patient.

CAUTION, See package insert for full
prescribing information and
Instructions for Use

Keep out of the sight and
reach of children.

Do not re-use

Refrigerate
unit ready
to use

AMGEN
ENBRELinjection.com
Rx Only

PRINCIPAL DISPLAY PANEL - 50 mg/mL Autoinjector Carton - 032-96

1 x Single-Dose Prefilled Autoinjector

NDC 58406-032-96

50
mg/mL

Enbrel®
etanercept

50 mg/mL
Single-dose Prefilled Autoinjector

Attention: Not for use in pediatric patients under 63 kg
(138 pounds)

For Subcutaneous Use Only

Sterile Solution - No Preservative
Refrigerate at 36°F to 46°F (2°C to 8°C). DO NOT FREEZE.

ATTENTION: Enclosed Medication Guide is required for each patient.

CAUTION, See package insert for full
prescribing information and
Instructions for Use

Keep out of the sight and
reach of children

Do not re-use

Refrigerate
until ready
to use

Not for Sale

AMGEN
ENBRELinjection.com
Rx Only

PACKAGE LABEL

PRINCIPAL DISPLAY PANEL
Contains 4 Multi-Dose Trays
NDC 58406-425-34
AMGEN®
Enbrel®
etanercept
25 mg/vial
Multiple-Dose Vial
See package insert for full prescribing information
and instructions for preparation and administration.
25 mg/vial
Each vial contains a sterile lyophilized preparation
of 25 mg etanercept (a recombinant CHO cell-derived
product), 40 mg mannitol, 10 mg sucrose, and
1.2 mg tromethamine.
Specific activitiy: approximately 1.7 x 10^6 U/mg.
No U.S. standard of potency. Volume after reconstitution
with 1 mL diluent is 1 mL.
Before and after reconstitution refrigerate
at 2° to 8°C (36° to 46°F). DO NOT FREEZE.
For Subcutaneous Use Only
AMGEN®
Manufactured by Immunex Corporation, Thousand Oaks, CA 91320
Contains diluent syringes (Made in Germany)
U.S. License No. 1132
©2013, 2016 Immunex Corporation
Patent: http://pat.amgen.com/enbrel/

PRINCIPAL DISPLAY PANEL - 50 mg/mL Cartridge Carton

Contains 4 Single-dose prefilled cartridges

NDC 58406-044-04

Enbrel®
etanercept

50
mg/mL

Not made with
natural rubber latex

Enbrel Mini® prefilled cartridge
50 mg/mL
Single-dose prefilled cartridge
For use with all AutoTouch® reusable autoinjectors only

Attention: Not for use in pediatric patient under 138 lbs.
For Subcutaneous Use Only
Sterile Solution – No Preservative
Refrigerate at 2° to 8°C (36° to 46°F). DO NOT FREEZE. DO NOT SHAKE.

Carton contents (4 prefilled cartridges, 1 package insert with attached
Medication Guide) are intended to be dispensed as a unit.

ATTENTION: Enclosed Medication Guide is required for each patient.

Do not Reuse

CAUTION, See package insert
for full prescribing information
and Instructions for Use

Rx Only

AMGEN®

↓ OPEN HERE ↓

PRINCIPAL DISPLAY PANEL - 50 mg/mL Single-dose Prefilled Cartridge Autoinjector Label

NDC 58406-480-01

AMGEN®

Bluetooth®

AutoTouch Connect™
reusable autoinjector

For use with Enbrel Mini® (etanercept)
single-dose prefilled cartridge

Contains 1 AutoTouch Connect™ reusable autoinjector
For Subcutaneous Use Only

Store in a dry place at room temperature: 50°F to 104°F (10°C to 40°C)
IP52 – This package will resisit drops of water and dust.

Do Not Use if Package is Damaged
Type BF Applied Part
MR unsafe
Exp: Expiry Date
Follow instructions for use

Rx Only

PRINCIPAL DISPLAY PANEL - 25 mg/0.5 mL Vial Carton

4 Single-Dose Vials, each vial is 25 mg/0.5mL
NDC 58406-055-04

AMGEN®

Enbrel®
etanercept
Injection

25
mg

25 mg/0.5 mL
Single-Dose Vial – Discard unused portion

For Subcutaneous Use Only.
Sterile Solution - No Preservative.
Store refrigerated at 2° to 8°C (36° to 46°F). DO NOT FREEZE.
DO NOT SHAKE.
Protect from Light.

U.S. License No. 1132
Manufactured by Immunex Corporation
Thousand Oaks, CA 91320-1799 U.S.A.
© 2020, 2022-2023 Immunex Corporation

Rx Only